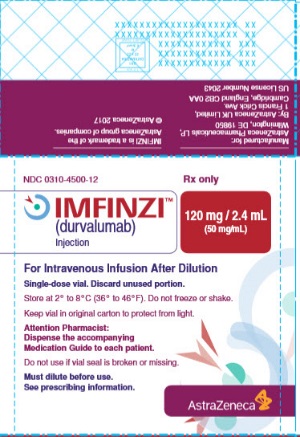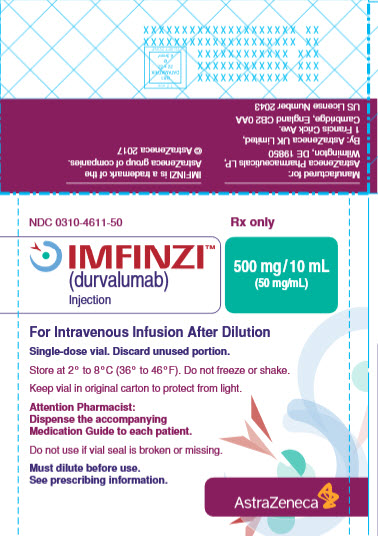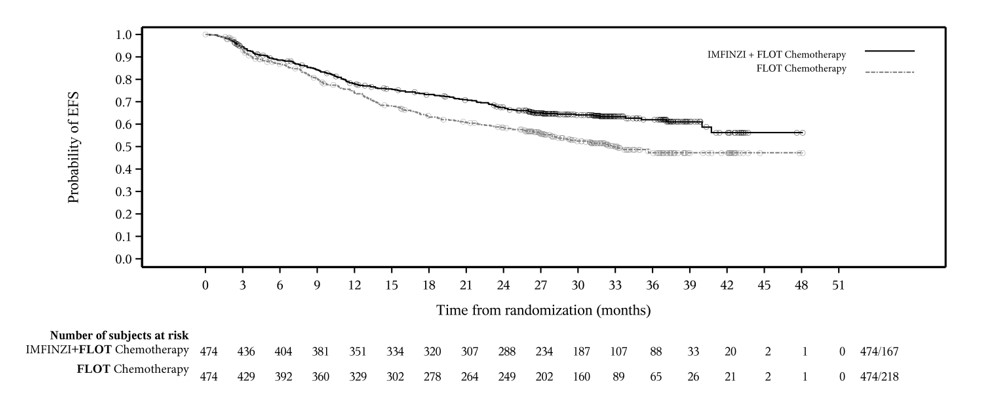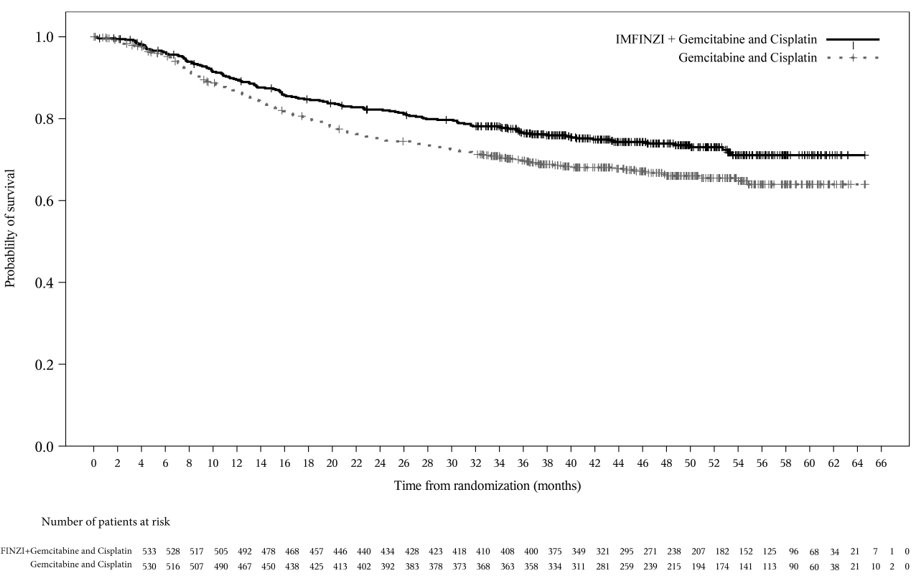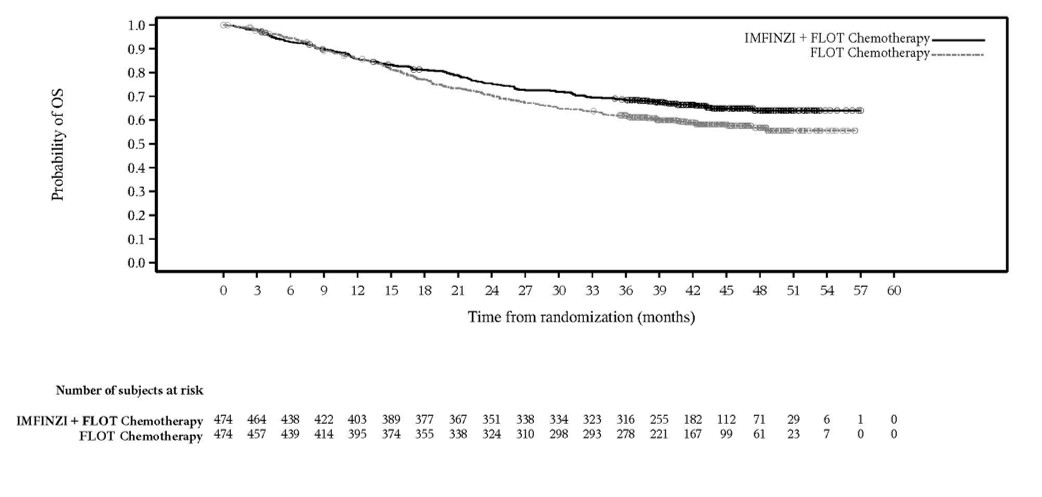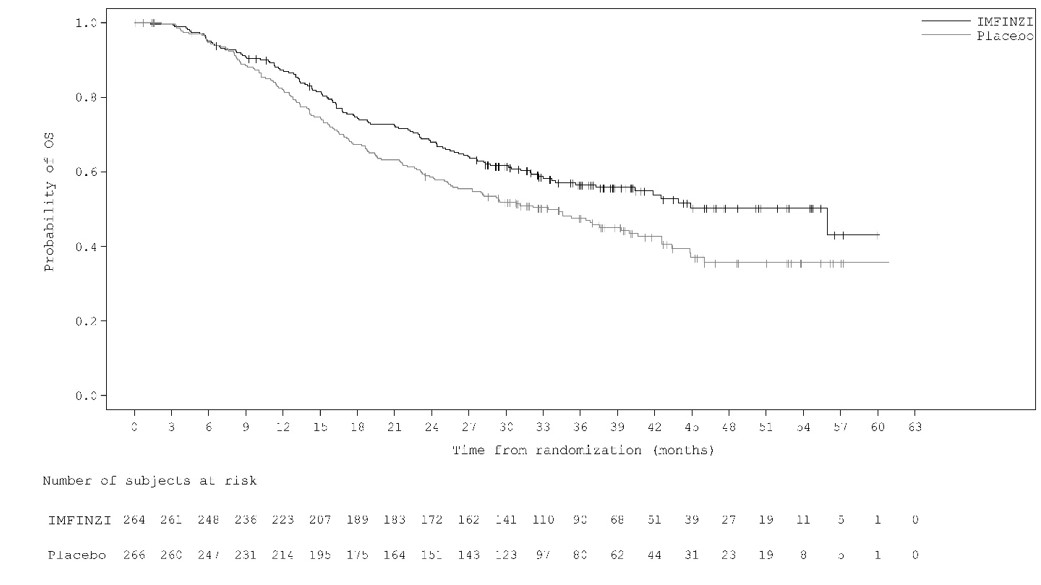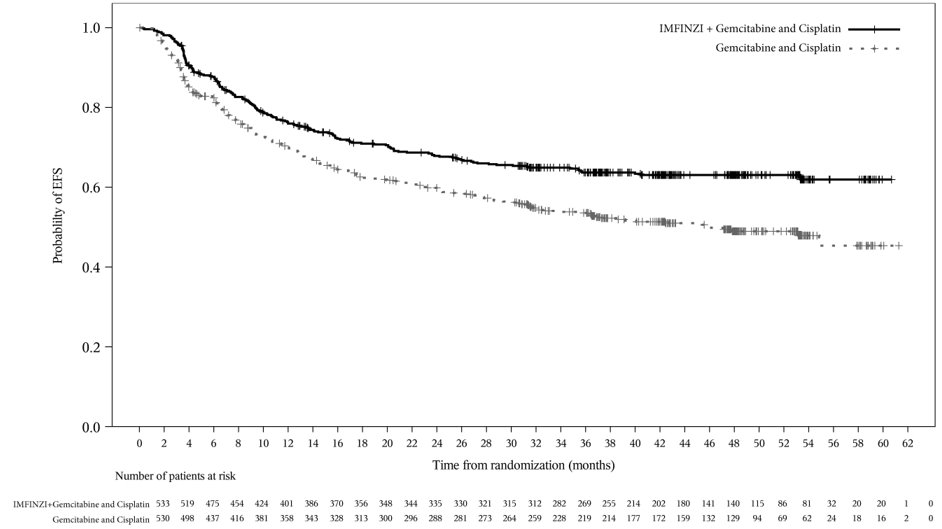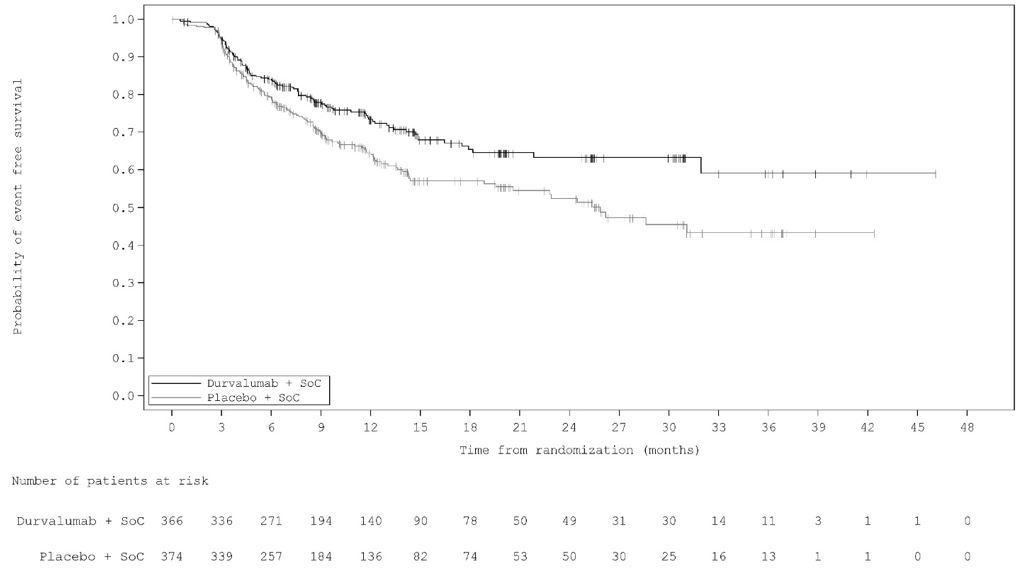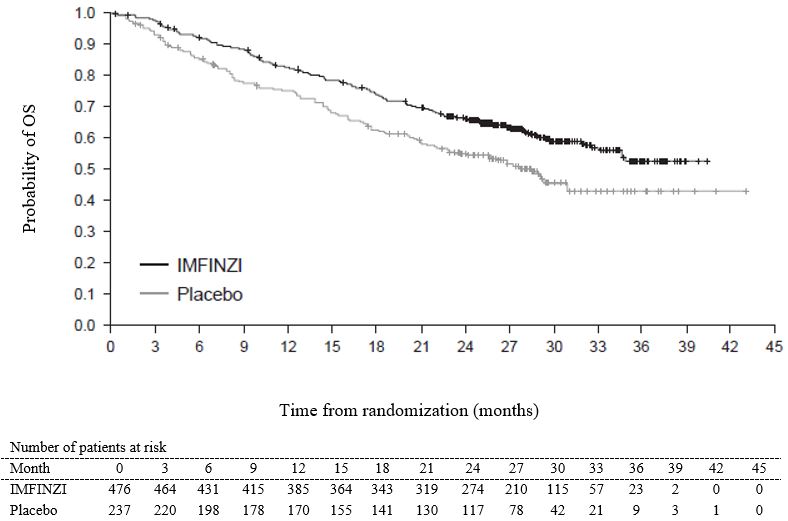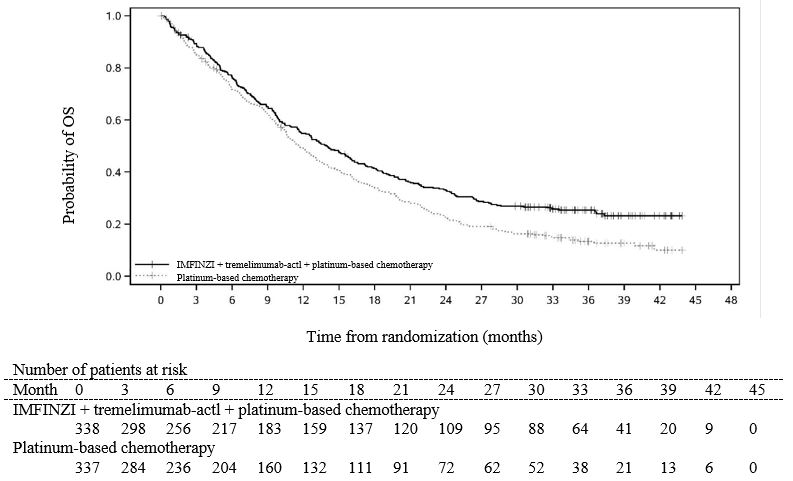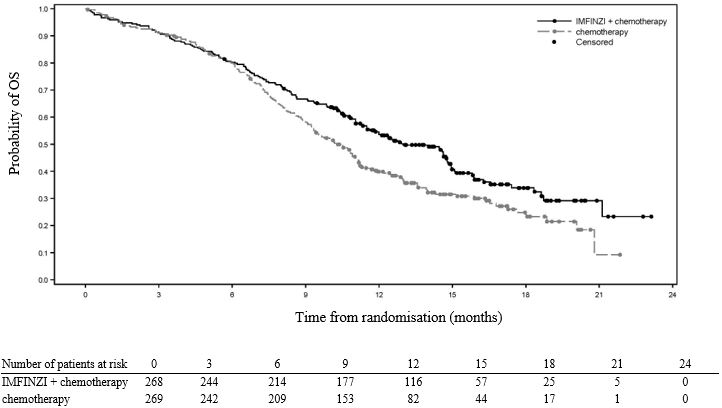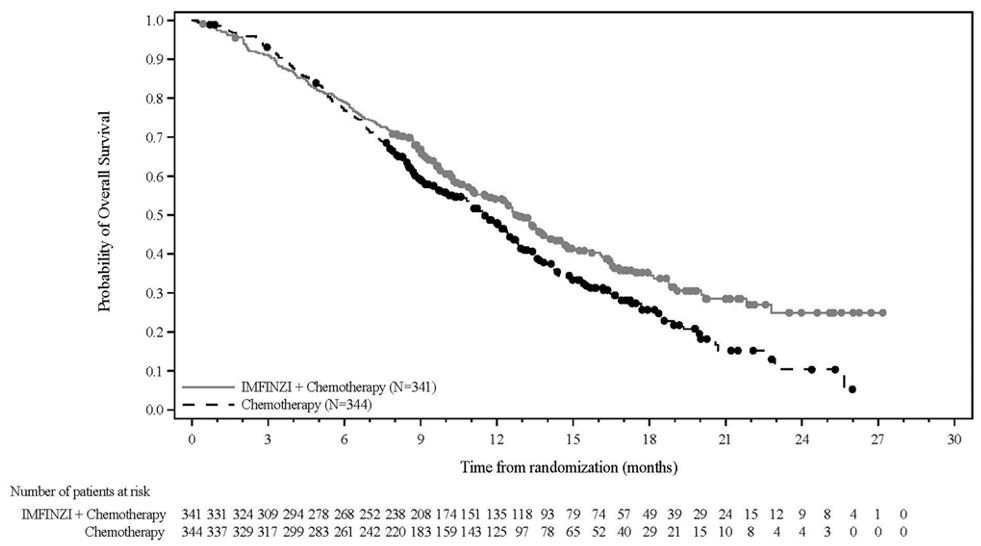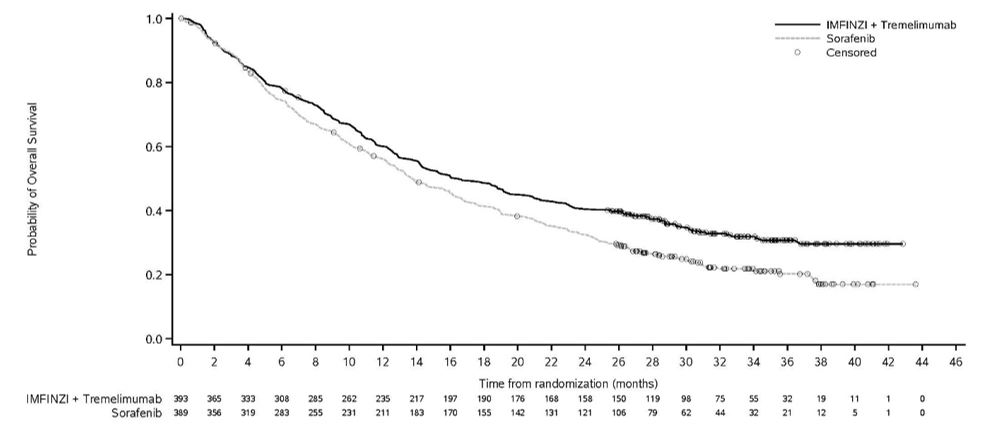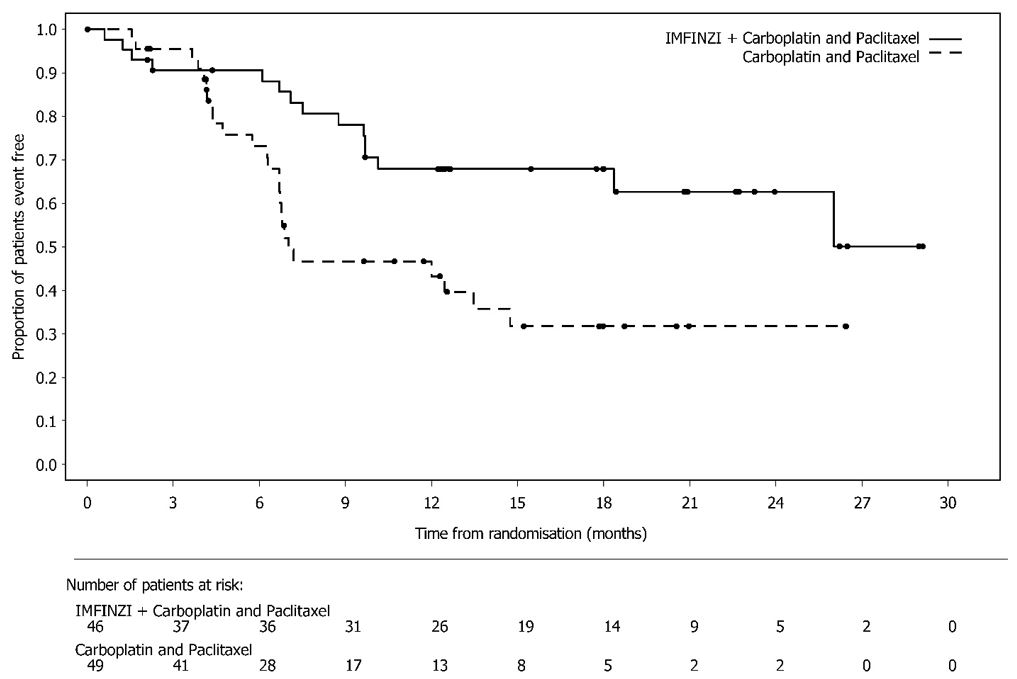 DRUG LABEL: IMFINZI
NDC: 0310-4500 | Form: INJECTION, SOLUTION
Manufacturer: AstraZeneca Pharmaceuticals LP
Category: prescription | Type: HUMAN PRESCRIPTION DRUG LABEL
Date: 20251125

ACTIVE INGREDIENTS: DURVALUMAB 120 mg/2.4 mL
INACTIVE INGREDIENTS: HISTIDINE 4.8 mg/2.4 mL; HISTIDINE MONOHYDROCHLORIDE MONOHYDRATE 6.5 mg/2.4 mL; POLYSORBATE 80 0.5 mg/2.4 mL; TREHALOSE DIHYDRATE 250 mg/2.4 mL; WATER

HIGHLIGHTS OF PRESCRIBING INFORMATION

These highlights do not include all the information needed to use IMFINZI safely and effectively. See full prescribing information for IMFINZI.
IMFINZI® (durvalumab) injection, for intravenous use
Initial U.S. Approval: 2017

RECENT MAJOR CHANGES

Indications and Usage (1.1, 1.2) 12/2024

Indications and Usage (1.5) 02/2025

Indications and Usage (1.6) 03/2025

Indications and Usage (1.7) 11/2025

Dosage and Administration (2.1) 02/2025

Dosage and Administration (2.1, 2.2, 2.3, 2.4) 12/2024

Dosage and Administration (2.2, 2.4) 03/2025

Dosage and Administration (2.2) 11/2025

Warnings and Precautions (5.1) 12/2024

1 INDICATIONS AND USAGE

IMFINZI is a programmed death-ligand 1 (PD-L1) blocking antibody indicated:

- in combination with platinum-containing chemotherapy as neoadjuvant treatment, followed by IMFINZI continued as a single agent as adjuvant treatment after surgery, for the treatment of adult patients with resectable (tumors ≥ 4 cm and/or node positive) non-small cell lung cancer (NSCLC) and no known epidermal growth factor receptor (EGFR) mutations or anaplastic lymphoma kinase (ALK) rearrangements. (1.1)
- as a single agent, for the treatment of adult patients with unresectable, Stage III NSCLC whose disease has not progressed following concurrent platinum-based chemotherapy and radiation therapy. (1.1)
- in combination with tremelimumab-actl and platinum-based chemotherapy, for the treatment of adult patients with metastatic NSCLC with no sensitizing EGFR mutations or ALK genomic tumor aberrations. (1.1)
- as a single agent, for the treatment of adult patients with limited-stage small cell lung cancer (LS-SCLC) whose disease has not progressed following concurrent platinum-based chemotherapy and radiation therapy. (1.2)
- in combination with etoposide and either carboplatin or cisplatin, as first-line treatment of adult patients with extensive-stage small cell lung cancer (ES-SCLC). (1.2)
- in combination with gemcitabine and cisplatin, as treatment of adult patients with locally advanced or metastatic biliary tract cancer (BTC). (1.3)
- in combination with tremelimumab-actl, for the treatment of adult patients with unresectable hepatocellular carcinoma (uHCC). (1.4)
- in combination with carboplatin and paclitaxel followed by IMFINZI as a single agent, for the treatment of adult patients with primary advanced or recurrent endometrial cancer that is mismatch repair deficient (dMMR) as determined by an FDA-approved test. (1.5, 2.1)
- in combination with gemcitabine and cisplatin as neoadjuvant treatment, followed by single agent IMFINZI as adjuvant treatment following radical cystectomy, for the treatment of adult patients with muscle invasive bladder cancer (MIBC). (1.6)
- in combination with fluorouracil, leucovorin, oxaliplatin, and docetaxel (FLOT) chemotherapy as neoadjuvant and adjuvant treatment, followed by single agent IMFINZI, for the treatment of adult patients with resectable gastric or gastroesophageal junction adenocarcinoma (GC/GEJC). (1.7)

2 DOSAGE AND ADMINISTRATION

- Administer IMFINZI as an intravenous infusion over 60 minutes after dilution. (2.4)
- Neoadjuvant and Adjuvant Treatment of Resectable NSCLC:
  ∘ Weight ≥ 30 kg:

Neoadjuvant: IMFINZI 1,500 mg in combination with chemotherapy every 3 weeks for up to 4 cycles prior to surgery.

Adjuvant: IMFINZI 1,500 mg as a single agent every 4 weeks for up to 12 cycles after surgery. (2.2)

  ∘ Weight < 30 kg

Neoadjuvant: IMFINZI 20 mg/kg every 3 weeks in combination with chemotherapy for up to 4 cycles prior to surgery.

Adjuvant: 20 mg/kg every 4 weeks as a single agent for up to 12 cycles after surgery. (2.2)

- Unresectable Stage III NSCLC, following concurrent platinum-based chemotherapy and radiation therapy:
  ∘ Weight ≥ 30 kg: IMFINZI 10 mg/kg every 2 weeks or 1,500 mg every 4 weeks. (2.2)
  ∘ Weight < 30 kg: IMFINZI 10 mg/kg every 2 weeks. (2.2)
- Metastatic NSCLC:
  ∘ Weight ≥ 30 kg: IMFINZI 1,500 mg every 3 weeks in combination with tremelimumab-actl 75 mg and platinum-based chemotherapy for 4 cycles, and then administer IMFINZI 1,500 mg every 4 weeks as a single agent with histology-based pemetrexed maintenance therapy every 4 weeks, and a fifth dose of tremelimumab-actl 75 mg in combination with IMFINZI dose 6 at week 16. (2.2)
  ∘ Weight < 30 kg: IMFINZI 20 mg/kg every 3 weeks in combination with tremelimumab-actl 1 mg/kg and platinum-based chemotherapy, and then administer IMFINZI 20 mg/kg every 4 weeks as a single agent with histology-based pemetrexed therapy every 4 weeks, and a fifth dose of tremelimumab-actl 1 mg/kg in combination with IMFINZI dose 6 at week 16. (2.2)
- LS-SCLC, following concurrent platinum-based chemotherapy and radiation therapy:
  ∘ Weight ≥ 30 kg: 1,500 mg every 4 weeks. (2.2)
  ∘ Weight < 30 kg: 20 mg/kg every 4 weeks. (2.2)
- ES-SCLC:
  ∘ Weight ≥ 30 kg: With etoposide and either carboplatin or cisplatin, administer IMFINZI 1,500 mg every 3 weeks in combination with chemotherapy, and then 1,500 mg every 4 weeks as a single agent. (2.2)
  ∘ Weight < 30 kg: With etoposide and either carboplatin or cisplatin, administer IMFINZI 20 mg/kg every 3 weeks in combination with chemotherapy, and then 10 mg/kg every 2 weeks as a single agent. (2.2)
- BTC:
  ∘ Weight ≥ 30 kg: administer IMFINZI 1,500 mg every 3 weeks in combination with chemotherapy, and then 1,500 mg every 4 weeks as a single agent. (2.2)
  ∘ Weight < 30 kg: administer IMFINZI 20 mg/kg every 3 weeks in combination with chemotherapy, and then 20 mg/kg every 4 weeks as a single agent. (2.2)
- uHCC:
  ∘ Weight ≥ 30 kg: IMFINZI 1,500 mg in combination with tremelimumab-actl 300 mg as a single dose at Cycle 1/Day 1, followed by IMFINZI as a single agent every 4 weeks. (2.2)
  ∘ Weight < 30 kg: IMFINZI 20 mg/kg in combination with tremelimumab-actl 4 mg/kg as a single dose at Cycle 1/Day 1, followed by IMFINZI as a single agent every 4 weeks. (2.2)
- dMMR endometrial cancer:
  ∘ Weight ≥ 30 kg: IMFINZI 1,120 mg in combination with carboplatin and paclitaxel every 3 weeks for 6 cycles, followed by IMFINZI 1,500 mg every 4 weeks as a single agent. (2.1, 2.2)
  ∘ Weight < 30 kg: IMFINZI 15 mg/kg in combination with carboplatin and paclitaxel every 3 weeks for 6 cycles, followed by IMFINZI 20 mg/kg every 4 weeks as a single agent. (2.1, 2.2)
- MIBC:
  ∘ Weight ≥ 30 kg:

Neoadjuvant: IMFINZI 1,500 mg in combination with gemcitabine and cisplatin every 3 weeks for 4 cycles prior to surgery.

Adjuvant: IMFINZI 1,500 mg every 4 weeks as a single agent for up to 8 cycles after surgery. (2.2)

  ∘ Weight < 30 kg:

Neoadjuvant: IMFINZI 20 mg/kg in combination with gemcitabine and cisplatin every 3 weeks for 4 cycles prior to surgery.

Adjuvant: IMFINZI 20 mg/kg every 4 weeks as a single agent for up to 8 cycles after surgery. (2.2)

- See full Prescribing Information for preparation and administration instructions and dosage modifications for adverse reactions.

3 DOSAGE FORMS AND STRENGTHS

- Injection: 500 mg/10 mL (50 mg/mL) solution in a single-dose vial. (3)
- Injection: 120 mg/2.4 mL (50 mg/mL) solution in a single-dose vial. (3)

4 CONTRAINDICATIONS

None. (4)

5 WARNINGS AND PRECAUTIONS

- Immune-Mediated Adverse Reactions (5.1)
  ∘ Immune-mediated adverse reactions, which may be severe or fatal, can occur in any organ system or tissue, including the following: immune-mediated pneumonitis, immune-mediated colitis, immune-mediated hepatitis, immune-mediated endocrinopathies, immune-mediated dermatologic adverse reactions, immune-mediated nephritis and renal dysfunction, solid organ transplant rejection, and immune-mediated pancreatitis.
    - Monitor for early identification and management. Evaluate liver enzymes, creatinine, and thyroid function at baseline and periodically during treatment.
    - Withhold or permanently discontinue based on severity and type of reaction.
- Infusion-Related Reactions: Interrupt, slow the rate of infusion, or permanently discontinue IMFINZI based on the severity of the reaction. (5.2)
- Complications of Allogeneic HSCT: Fatal and other serious complications can occur in patients who receive allogeneic HSCT before or after being treated with a PD-1/PD-L1 blocking antibody. (5.3)
- Embryo-Fetal Toxicity: Can cause fetal harm. Advise females of reproductive potential of the potential risk to a fetus and use of effective contraception. (5.4, 8.1, 8.3)

6 ADVERSE REACTIONS

IMFINZI in Combination with Chemotherapy

- Most common adverse reactions (≥ 20%) of patients with resectable, Stage II/III NSCLC [neoadjuvant /adjuvant]) are anemia, nausea, constipation, fatigue, musculoskeletal pain, and rash. (6.1)

IMFINZI as a Single Agent

- Most common adverse reactions (≥ 20%) of patients with unresectable, Stage III NSCLC) are cough, fatigue, pneumonitis/radiation pneumonitis, upper respiratory tract infections, dyspnea, and rash. (6.1)

IMFINZI in Combination with Tremelimumab-actl and Platinum-Based Chemotherapy

- Most common adverse reactions (≥ 20%) of patients with metastatic NSCLC) are nausea, fatigue, musculoskeletal pain, decreased appetite, rash, and diarrhea. (6.1)

IMFINZI as a Single Agent

- Most common adverse reactions (≥ 20%) of patients with limited-stage SCLC) are pneumonitis or radiation pneumonitis, and fatigue. (6.1)

IMFINZI in Combination with Platinum-Based Chemotherapy

- Most common adverse reactions (≥ 20%) of patients with extensive-stage SCLC) are nausea, fatigue/asthenia, and alopecia. (6.1)

IMFINZI in Combination with Gemcitabine and Cisplatin

- Most common adverse reactions (≥ 20%) of patients with BTC) are fatigue, nausea, constipation, decreased appetite, abdominal pain, rash, and pyrexia. (6.1)

IMFINZI in Combination with Tremelimumab-actl

- Most common adverse reactions (≥ 20%) of patients with uHCC) are rash, diarrhea, fatigue, pruritus, musculoskeletal pain, and abdominal pain. (6.1)

IMFINZI in Combination with Carboplatin and Paclitaxel, followed by IMFINZI as a single agent

- Most common adverse reactions (≥ 20%) of patients with endometrial cancer) were peripheral neuropathy, musculoskeletal pain, nausea, alopecia, fatigue, abdominal pain, constipation, rash, decreased magnesium, increased ALT, increased AST, diarrhea, vomiting, cough, decreased potassium, dyspnea, headache, and increased alkaline phosphatase. (6.1)

IMFINZI in Combination with Gemcitabine and Cisplatin, followed by IMFINZI as a single agent

- Most common adverse reactions (≥ 20% of patients with MIBC) were decreased hemoglobin, decreased neutrophils, increased blood creatinine, decreased sodium, nausea, increased ALT, decreased calcium, decreased platelets, fatigue, increased potassium, decreased lymphocytes, increased AST, constipation, decreased magnesium, decreased appetite, increased alkaline phosphate, rash, pyrexia, diarrhea, vomiting and abdominal pain. (6.1)

IMFINZI in Combination with FLOT Chemotherapy followed by IMFINZI as a single agent

- Most common adverse reactions (≥ 20% of patients with resectable GC/GEJC) were diarrhea, nausea, peripheral neuropathy, fatigue, alopecia, decreased appetite, rash, abdominal pain, vomiting, musculoskeletal pain, pyrexia, and stomatitis (6.1).

To report SUSPECTED ADVERSE REACTIONS, contact AstraZeneca at 1-800-236-9933 or FDA at 1-800-FDA-1088 or www.fda.gov/medwatch.

8 USE IN SPECIFIC POPULATIONS

Lactation: Advise not to breastfeed. (8.2)

FULL PRESCRIBING INFORMATION

1 INDICATIONS AND USAGE

1.1 Non-Small Cell Lung Cancer

- IMFINZI in combination with platinum-containing chemotherapy as neoadjuvant treatment, followed by IMFINZI continued as a single agent as adjuvant treatment after surgery, is indicated for the treatment of adult patients with resectable (tumors ≥ 4 cm and/or node positive) non-small cell lung cancer (NSCLC) and no known epidermal growth factor receptor (EGFR) mutations or anaplastic lymphoma kinase (ALK) rearrangements.
- IMFINZI, as a single agent, is indicated for the treatment of adult patients with unresectable Stage III NSCLC whose disease has not progressed following concurrent platinum-based chemotherapy and radiation therapy (cCRT).
- IMFINZI, in combination with tremelimumab-actl and platinum-based chemotherapy, is indicated for the treatment of adult patients with metastatic NSCLC with no sensitizing EGFR mutations or ALK genomic tumor aberrations.

1.2 Small Cell Lung Cancer

- IMFINZI, as a single agent, is indicated for the treatment of adult patients with limited-stage small cell lung cancer (LS-SCLC) whose disease has not progressed following concurrent platinum-based chemotherapy and radiation therapy (cCRT).
- IMFINZI, in combination with etoposide and either carboplatin or cisplatin, is indicated for the first-line treatment of adult patients with extensive-stage small cell lung cancer (ES-SCLC).

1.3 Biliary Tract Cancers

IMFINZI, in combination with gemcitabine and cisplatin, is indicated for the treatment of adult patients with locally advanced or metastatic biliary tract cancer (BTC).

1.4 Hepatocellular Carcinoma

IMFINZI, in combination with tremelimumab-actl, is indicated for the treatment of adult patients with unresectable hepatocellular carcinoma (uHCC).

1.5 Endometrial Cancer

IMFINZI, in combination with carboplatin and paclitaxel followed by IMFINZI as a single agent, is indicated for the treatment of adult patients with primary advanced or recurrent endometrial cancer that is mismatch repair deficient (dMMR) as determined by an FDA-approved test [see Dosage and Administration (2.1)].

1.6 Bladder Cancer

IMFINZI in combination with gemcitabine and cisplatin as neoadjuvant treatment, followed by single agent IMFINZI as adjuvant treatment following radical cystectomy, is indicated for the treatment of adult patients with muscle invasive bladder cancer (MIBC).

1.7 Gastric or gastroesophageal junction adenocarcinoma

IMFINZI in combination with fluorouracil, leucovorin, oxaliplatin and docetaxel (FLOT) as neoadjuvant and adjuvant treatment, followed by single-agent IMFINZI, is indicated for the treatment of adult patients with resectable gastric or gastroesophageal junction adenocarcinoma (GC/GEJC).

2 DOSAGE AND ADMINISTRATION

2.1 Patient Selection

Advanced or Recurrent dMMR Endometrial Cancer

Select patients for treatment based on the presence of dMMR in tumor specimens [see Clinical Studies (14.5)].

Information on FDA-approved tests for the detection of dMMR status in endometrial cancer is available at https://www.fda.gov/companiondiagnostics.

2.2 Recommended Dosage

The recommended dosages for IMFINZI as a single agent and IMFINZI in combination with other therapeutic agents are presented in Table 1. The recommended dosage schedule and regimens for IMFINZI for the treatment of metastatic NSCLC are provided in Tables 2 and 3 [see Indications and Usage (1.1)].

Administer IMFINZI as a 60 minute intravenous infusion after dilution [see Dosage and Administration (2.3)].

Table 1. Recommended Dosages of IMFINZI
Indication | Recommended IMFINZI Dosage | Duration of Therapy
Neoadjuvant and Adjuvant Treatment of Resectable NSCLC | Patients with a body weight of ≥ 30 kg: Neoadjuvant: IMFINZI 1,500 mg in combination with chemotherapy [Administer IMFINZI prior to chemotherapy on the same day. Refer to the Prescribing Information for the agent administered in combination with IMFINZI for recommended dosage information, as appropriate.] every 3 weeks for up to 4 cycles prior to surgery Adjuvant: IMFINZI 1,500 mg as a single agent every 4 weeks for up to 12 cycles after surgery. Patients with a body weight of < 30 kg: Neoadjuvant: IMFINZI 20 mg/kg every 3 weeks in combination with chemotherapy for up to 4 cycles prior to surgery. Adjuvant: IMFINZI 20 mg/kg every 4 weeks for up to 12 cycles as a single agent after surgery. | Until disease progression that precludes definitive surgery, recurrence, unacceptable toxicity, or a maximum of 12 cycles after surgery
Unresectable Stage III NSCLC | Following concurrent platinum-based chemotherapy and radiation therapy: Patients with a body weight of ≥ 30 kg: 10 mg/kg every 2 weeks or 1,500 mg every 4 weeks Patients with a body weight of < 30 kg: 10 mg/kg every 2 weeks | Until disease progression, unacceptable toxicity, or a maximum of 12 months
Limited Stage SCLC | Following concurrent platinum-based chemotherapy and radiation therapy: Patients with a body weight of ≥ 30 kg: 1,500 mg every 4 weeks Patients with a body weight of < 30 kg: 20 mg/kg every 4 weeks | Until disease progression, unacceptable toxicity, or a maximum of 24 months
Extensive Stage SCLC | Patients with a body weight of ≥ 30 kg: 1,500 mg in combination with chemotherapy every 3 weeks (21 days) for 4 cycles, followed by 1,500 mg every 4 weeks as a single agent Patients with a body weight of < 30 kg: 20 mg/kg in combination with chemotherapy every 3 weeks (21 days) for 4 cycles, followed by 10 mg/kg every 2 weeks as a single agent | Until disease progression or until unacceptable toxicity
BTC | Patients with a body weight of ≥ 30 kg: 1,500 mg in combination with chemotherapy every 3 weeks (21 days) up to 8 cycles followed by 1,500 mg every 4 weeks as a single agent Patients with a body weight of < 30 kg: 20 mg/kg in combination with chemotherapy every 3 weeks (21 days) up to 8 cycles, followed by 20 mg/kg every 4 weeks as a single agent | Until disease progression or until unacceptable toxicity
uHCC | Patients with a body weight of ≥ 30 kg: IMFINZI 1,500 mg following a single dose of tremelimumab-actl [Administer tremelimumab-actl prior to IMFINZI on the same day. When tremelimumab-actl is administered in combination with IMFINZI, refer to the Prescribing Information for tremelimumab-actl dosing information.] 300 mg at Day 1 of Cycle 1; Continue IMFINZI 1,500 mg as a single agent every 4 weeks Patients with a body weight of < 30 kg: IMFINZI 20 mg/kg following a single dose of tremelimumab-actl 4 mg/kg at Day 1 of Cycle 1; Continue IMFINZI 20 mg/kg as a single agent every 4 weeks | After Cycle 1 of combination therapy, administer IMFINZI as a single agent every 4 weeks until disease progression or unacceptable toxicity
dMMR endometrial cancer | Patients with a body weight of ≥ 30 kg: IMFINZI 1,120 mg in combination with carboplatin and paclitaxel every 3 weeks (21 days) for 6 cycles, followed by IMFINZI 1,500 mg every 4 weeks as a single agent Patients with a body weight of < 30 kg: IMFINZI 15 mg/kg in combination with carboplatin and paclitaxel every 3 weeks (21 days) for 6 cycles, followed by IMFINZI 20 mg/kg every 4 weeks as a single agent | Until disease progression or unacceptable toxicity
Neoadjuvant and Adjuvant Treatment of MIBC | Patients with a body weight of ≥30 kg: Neoadjuvant: 1,500 mg in combination with gemcitabine and cisplatin every 3 weeks for 4 cycles prior to surgery Adjuvant: IMFINZI 1,500 mg as a single agent every 4 weeks for up to 8 cycles after surgery Patients with a body weight of < 30 kg: Neoadjuvant: 20 mg/kg in combination with gemcitabine and cisplatin every 3 weeks for 4 cycles prior to surgery Adjuvant: IMFINZI 20 mg/kg as a single agent every 4 weeks for up to 8 cycles after surgery | Until disease progression that precludes definitive surgery, recurrence, or unacceptable toxicity or a maximum of 8 cycles after surgery
Neoadjuvant and Adjuvant Treatment of Resectable GC/GEJC | Patients with a body weight of ≥ 30 kg: Neoadjuvant: IMFINZI 1,500 mg every 4 weeks with FLOT [FLOT chemotherapy is administered on days 1 and 15 of each 4 week cycle [See Clinical Studies (14.7)].] for up to 2 cycles prior to surgery Adjuvant: IMFINZI 1,500 mg every 4 weeks with FLOT for up to 2 cycles, followed by IMFINZI 1,500 mg as a single agent every 4 weeks for up to 10 cycles Patients with a body weight of < 30 kg: Neoadjuvant: IMFINZI 20 mg/kg every 4 weeks with FLOT*± for up to 2 cycles prior to surgery Adjuvant: IMFINZI 20 mg/kg every 4 weeks with FLOT for up to 2 cycles, followed by IMFINZI 20 mg/kg as a single agent every 4 weeks for up to 10 cycles | Neoadjuvant: Until disease progression that precludes definitive surgery or unacceptable toxicity

IMFINZI in Combination with Tremelimumab-actl and Platinum-Based Chemotherapy

The recommended dosage schedule and regimens for IMFINZI for the treatment of metastatic NSCLC are provided in Tables 2 and 3.

Weigh patients prior to each infusion.

Calculate the appropriate dose using Table 3 below based on the patient’s weight and tumor histology.

Table 2. Recommended Dosage Schedule for Metastatic NSCLC
 | Week [continue IMFINZI until disease progression or intolerable toxicity.] [note the dosing interval change from every 3 weeks to every 4 weeks starting at cycle 5.]
 | 0 | 1 | 2 | 3 | 4 | 5 | 6 | 7 | 8 | 9 | 10 | 11 | 12 | 13 | 14 | 15 | 16 | 17 | 18 | 19 | 20 | 21 | 22 | 23 | 24
Cycle: | 1 |  |  | 2 |  |  | 3 |  |  | 4 |  |  | 5 |  |  |  | 6 |  |  |  | 7 |  |  |  | 8
IMFINZI [intravenous infusion over 60 minutes [see Dosage and Administration (2.4)].] | X |  |  | X |  |  | X |  |  | X |  |  | X |  |  |  | X |  |  |  | X |  |  |  | X
Tremelimumab-actl [if patients receive fewer than 4 cycles of platinum-based chemotherapy, the remaining cycles of tremelimumab-actl (up to a total of 5) should be given after the platinum-based chemotherapy phase, in combination with IMFINZI, every 4 weeks.] | X |  |  | X |  |  | X |  |  | X |  |  |  |  |  |  | X
Chemotherapy | X |  |  | X |  |  | X |  |  | X |  |  | X [optional pemetrexed therapy from week 12 until disease progression or intolerable toxicity for patients with non-squamous disease who received treatment with pemetrexed and carboplatin/cisplatin.] |  |  |  | X |  |  |  | X |  |  |  | X

Table 3. Recommended Regimen and Dosage for Metastatic NSCLC
Tumor Histology | Patient Weight | IMFINZI Dosage | Tremelimumab-actl Dosage [Refer to the Prescribing Information for dosing information.] | Platinum-based Chemotherapy Regimen
Non-Squamous | ≥ 30 kg | 1,500 mg | 75 mg | - carboplatin & nab-paclitaxel; OR; - carboplatin or cisplatin & pemetrexed
Non-Squamous | < 30 kg | 20 mg/kg | 1 mg/kg | - carboplatin & nab-paclitaxel; OR; - carboplatin or cisplatin & pemetrexed
Squamous | ≥ 30 kg | 1,500 mg | 75 mg | - carboplatin & nab-paclitaxel; OR; - carboplatin or cisplatin & gemcitabine
Squamous | < 30 kg | 20 mg/kg | 1 mg/kg | - carboplatin & nab-paclitaxel; OR; - carboplatin or cisplatin & gemcitabine

2.3 Dosage Modifications for Adverse Reactions

No dose reduction for IMFINZI is recommended. In general, withhold IMFINZI for severe (Grade 3) immune-mediated adverse reactions. Permanently discontinue IMFINZI for life-threatening (Grade 4) immune-mediated adverse reactions, recurrent severe (Grade 3) immune-mediated reactions that require systemic immunosuppressive treatment, or an inability to reduce corticosteroid dose to 10 mg or less of prednisone or equivalent per day within 12 weeks of initiating corticosteroids.

Dosage modifications for IMFINZI or IMFINZI in combination with tremelimumab-actl or chemotherapy for adverse reactions that require management different from these general guidelines are summarized in Table 4.

Table 4. Recommended Dosage Modifications for Adverse Reactions
Adverse Reaction | Severity [Based on National Cancer Institute Common Terminology Criteria for Adverse Events, version 4.03.] | Dosage Modification
Immune-Mediated Adverse Reactions [see Warnings and Precautions (5.1)]
Pneumonitis | Grade 2 | Withhold [Resume in patients with complete or partial resolution (Grade 0 to 1) after corticosteroid taper. Permanently discontinue if no complete or partial resolution within 12 weeks of initiating corticosteroids or an inability to reduce corticosteroid dose to 10 mg of prednisone or less per day (or equivalent) within 12 weeks of initiating corticosteroids.]
Pneumonitis | Grade 3 or 4 | Permanently discontinue
Colitis | Grade 2 | Withhold
Colitis | Grade 3 | Withhold or permanently discontinue [Permanently discontinue IMFINZI for Grade 3 colitis when administered as part of a tremelimumab-actl containing regimen.]
Colitis | Grade 4 | Permanently discontinue
Intestinal perforation | Any grade | Permanently discontinue
Hepatitis with no tumor involvement of the liver | ALT or AST increases to more than 3 and up to 8 times the ULN; or; total bilirubin increases to more than 1.5 and up to 3 times ULN | Withhold
Hepatitis with no tumor involvement of the liver | ALT or AST increases to more than 8 times ULN; or; total bilirubin increases to more than 3 times the ULN | Permanently discontinue
Hepatitis with tumor involvement of the liver [If AST and ALT are less than or equal to ULN at baseline in patients with liver involvement, withhold or permanently discontinue IMFINZI based on recommendations for hepatitis with no liver involvement.] | AST or ALT is more than 1 and up to 3 times ULN at baseline and increases to more than 5 and up to 10 times ULN; or; AST or ALT is more than 3 and up to 5 times ULN at baseline and increases to more than 8 and up to 10 times ULN | Withhold
Hepatitis with tumor involvement of the liver [If AST and ALT are less than or equal to ULN at baseline in patients with liver involvement, withhold or permanently discontinue IMFINZI based on recommendations for hepatitis with no liver involvement.] | AST or ALT increases to more than 10 times ULN; or; total bilirubin increases to more than 3 times ULN | Permanently discontinue
Endocrinopathies | Grade 3 or 4 | Withhold until clinically stable or permanently discontinue depending on severity
Nephritis with Renal Dysfunction | Grade 2 or 3 increased blood creatinine | Withhold
Nephritis with Renal Dysfunction | Grade 4 increased blood creatinine | Permanently discontinue
Exfoliative Dermatologic Conditions | Suspected SJS, TEN, or DRESS | Withhold
Exfoliative Dermatologic Conditions | Confirmed SJS, TEN, or DRESS | Permanently discontinue
Myocarditis | Grade 2, 3, or 4 | Permanently discontinue
Neurological Toxicities | Grade 2 | Withhold
Neurological Toxicities | Grade 3 or 4 | Permanently discontinue
Other Adverse Reactions
Infusion-related reactions [see Warnings and Precautions (5.2)] | Grade 1 or 2 | Interrupt or slow the rate of infusion
Infusion-related reactions [see Warnings and Precautions (5.2)] | Grade 3 or 4 | Permanently discontinue
ALT = alanine aminotransferase, AST = aspartate aminotransferase, DRESS = Drug Rash with Eosinophilia and Systemic Symptoms, SJS = Stevens Johnson Syndrome, TEN = toxic epidermal necrolysis, ULN = upper limit normal.

2.4 Preparation and Administration

Preparation

- Visually inspect drug product for particulate matter and discoloration prior to administration, whenever solution and container permit. Discard the vial if the solution is cloudy, discolored, or visible particles are observed.
- Do not shake the vial.
- Withdraw the required volume from the vial(s) of IMFINZI and transfer into an intravenous bag containing 0.9% Sodium Chloride Injection, USP or 5% Dextrose Injection, USP. Mix diluted solution by gentle inversion. Do not shake the solution. The final concentration of the diluted solution should be between 1 mg/mL and 15 mg/mL.
- Discard partially used or empty vials of IMFINZI.

Storage of Infusion Solution

- IMFINZI does not contain a preservative.
- Administer infusion solution immediately once prepared. If the infusion solution is not administered immediately and needs to be stored, the time from preparation until the completion of the infusion should not exceed:
  ∘ 28 days in a refrigerator at 2°C to 8°C (36°F to 46°F)
  ∘ 8 hours at room temperature up to 25°C (77°F)
- Do not freeze.
- Do not shake.

Administration

- Administer infusion solution intravenously over 60 minutes through an intravenous line containing a sterile, low-protein binding 0.2 or 0.22 micron in-line filter.
- Use separate infusion bags and filters for each drug product.

IMFINZI in Combination with Other Products

- Administer all intravenous drug products as separate infusions.
- Do not co-administer other intravenous drugs through the same infusion line.
- For platinum-based chemotherapy, refer to Prescribing Information for administration information.
- For pemetrexed therapy, refer to Prescribing Information for administration information.

Combination Regimens: Order of Infusions

IMFINZI in Combination with Tremelimumab-actl

- Infuse tremelimumab-actl first, followed by IMFINZI on the same day of dosing.

IMFINZI in Combination with Tremelimumab-actl and Platinum-Based Chemotherapy

- Infuse tremelimumab-actl first, followed by IMFINZI and then platinum-based chemotherapy on the day of dosing.

IMFINZI in Combination with Tremelimumab-actl and Pemetrexed Therapy

- Infuse tremelimumab-actl first, followed by IMFINZI and then pemetrexed therapy on the day of dosing.

IMFINZI in Combination with Chemotherapy

- Infuse IMFINZI first and then chemotherapy on the same day of dosing.

Combination Regimens: Infusion Instructions

IMFINZI in Combination with Tremelimumab-actl

- Administer tremelimumab-actl over 60 minutes followed by a 60 minute observation period. Then administer IMFINZI as a separate intravenous infusion over 60 minutes.

IMFINZI in Combination with Tremelimumab-actl and Platinum-Based Chemotherapy/ Pemetrexed Therapy

Cycle 1

- Infuse tremelimumab-actl over 60 minutes. One to two hours after completion of tremelimumab-actl infusion, infuse IMFINZI over 60 minutes. One to two hours after completion of IMFINZI infusion, administer platinum-based chemotherapy.

Subsequent Cycles

- If there are no infusion reactions during cycle 1, subsequent cycles of IMFINZI can be given immediately after tremelimumab-actl. The time between the end of the IMFINZI infusion and the start of chemotherapy can be reduced to 30 minutes.

3 DOSAGE FORMS AND STRENGTHS

Injection: 120 mg/2.4 mL (50 mg/mL) and 500 mg/10 mL (50 mg/mL) clear to opalescent, colorless to slightly yellow solution in a single-dose vial.

4 CONTRAINDICATIONS

None.

5 WARNINGS AND PRECAUTIONS

5.1 Immune-Mediated Adverse Reactions

IMFINZI is a monoclonal antibody that belongs to a class of drugs that bind to either the programmed death-receptor 1 (PD-1) or the PD-ligand 1 (PD-L1), blocking the PD-1/PD-L1 pathway, thereby removing inhibition of the immune response, potentially breaking peripheral tolerance and inducing immune-mediated adverse reactions. Important immune-mediated adverse reactions listed under Warnings and Precautions may not include all possible severe and fatal immune-mediated reactions.

The incidence and severity of immune-mediated adverse reactions were similar when IMFINZI was administered as a single agent or in combination with chemotherapy or in combination with tremelimumab-actl and platinum-based chemotherapy, unless otherwise noted.

Immune-mediated adverse reactions, which may be severe or fatal, can occur in any organ system or tissue. Immune-mediated adverse reactions can occur at any time after starting treatment with a PD 1/PD L1 blocking antibody. While immune-mediated adverse reactions usually manifest during treatment with PD-1/PD-L1 blocking antibodies, immune-mediated adverse reactions can also manifest after discontinuation of PD-1/PD-L1 blocking antibodies.

Early identification and management of immune-mediated adverse reactions are essential to ensure safe use of PD-1/PD-L1 blocking antibodies. Monitor patients closely for symptoms and signs that may be clinical manifestations of underlying immune-mediated adverse reactions. Evaluate liver enzymes, creatinine, and thyroid function at baseline and periodically during treatment. In cases of suspected immune-mediated adverse reactions, initiate appropriate workup to exclude alternative etiologies, including infection. Institute medical management promptly, including specialty consultation as appropriate.

Withhold or permanently discontinue IMFINZI depending on severity [see Dosage and Administration (2.3)]. In general, if IMFINZI requires interruption or discontinuation, administer systemic corticosteroid therapy (1 mg to 2 mg/kg/day prednisone or equivalent) until improvement to Grade 1 or less. Upon improvement to Grade 1 or less, initiate corticosteroid taper and continue to taper over at least 1 month. Consider administration of other systemic immunosuppressants in patients whose immune-mediated adverse reactions are not controlled with corticosteroid therapy.

Toxicity management guidelines for adverse reactions that do not necessarily require systemic steroids (e.g., endocrinopathies and dermatologic reactions) are discussed below.

Immune-Mediated Pneumonitis

IMFINZI can cause immune-mediated pneumonitis. The incidence of pneumonitis is higher in patients who have received prior thoracic radiation.

IMFINZI as a Single Agent

In Patients Who Did Not Receive Recent Prior Radiation

In patients who received IMFINZI on clinical studies in which radiation therapy was generally not administered immediately prior to initiation of IMFINZI, the incidence of immune-mediated pneumonitis was 2.4% (34/1414), including fatal (< 0.1%), and Grade 3-4 (0.4%) adverse reactions. Events resolved in 19 of the 34 patients and resulted in permanent discontinuation in 5 patients. Systemic corticosteroids were required in 19 patients (19/34) with pneumonitis who did not receive chemoradiation prior to initiation of IMFINZI.

The frequency and severity of immune-mediated pneumonitis in patients who did not receive definitive chemoradiation prior to IMFINZI were similar whether IMFINZI was given as a single agent in patients with various cancers in a pooled data set or in patients with ES-SCLC or BTC when given in combination with chemotherapy.

In Patients Who Received Recent Prior Radiation

The incidence of pneumonitis (including radiation pneumonitis) in patients with unresectable Stage III NSCLC following definitive chemoradiation within 42 days prior to initiation of IMFINZI in PACIFIC was 18.3% (87/475) in patients receiving IMFINZI and 12.8% (30/234) in patients receiving placebo. Of the patients who received IMFINZI (475), 1.1% had a fatal adverse reaction and 2.7% had Grade 3 adverse reactions. Events resolved in 50 of the 87 (57%) patients and resulted in permanent discontinuation in 27 of the 87 (31%) patients. Systemic corticosteroids were required in 64 patients (64/87) with pneumonitis who had received chemoradiation prior to initiation of IMFINZI, while 2 patients required use of infliximab with high-dose steroids.

The incidence of pneumonitis (including radiation pneumonitis) in patients with LS-SCLC following chemoradiation within 42 days prior to initiation of IMFINZI in ADRIATIC was 14% (37/262) in patients receiving IMFINZI and 6% (16/265) in patients receiving placebo. Of the patients who received IMFINZI (262), 0.4% had a fatal adverse reaction and 2.7% had Grade 3 adverse reactions. Events resolved in 19 of the 37 (51%) patients and resulted in permanent discontinuation in 18 of the 37 (49%) patients. Systemic corticosteroids were required in all patients, while 1 patient required use of infliximab with high-dose steroids.

IMFINZI with Tremelimumab-actl

Immune-mediated pneumonitis occurred in 1.3% (5/388) of patients receiving IMFINZI in combination with tremelimumab-actl, including fatal (0.3%) and Grade 3 (0.2%) adverse reactions. Events resolved in 3 of the 5 patients and resulted in permanent discontinuation in 1 patient. Systemic corticosteroids were required in all patients; of these, 4 patients required high-dose corticosteroid treatment (at least 40 mg prednisone or equivalent per day). One patient (1/5) required other immunosuppressants.

IMFINZI with Tremelimumab-actl and Platinum-Based Chemotherapy

Immune-mediated pneumonitis occurred in 3.5% (21/596) of patients receiving IMFINZI in combination with tremelimumab-actl and platinum-based chemotherapy, including fatal (0.5%), and Grade 3 (1%) adverse reactions. Events resolved in 11 of the 21 patients and resulted in permanent discontinuation in 7 patients. Systemic corticosteroids were required in all patients with immune-mediated pneumonitis, while 1 patient (1/21) required other immunosuppressants.

Immune-Mediated Colitis

IMFINZI can cause immune-mediated colitis that is frequently associated with diarrhea. Cytomegalovirus (CMV) infection/reactivation has been reported in patients with corticosteroid-refractory immune-mediated colitis. In cases of corticosteroid-refractory colitis, consider repeating infectious workup to exclude alternative etiologies.

IMFINZI as a Single Agent

Immune-mediated colitis occurred in 2% (37/1889) of patients receiving IMFINZI, including Grade 4 (< 0.1%) and Grade 3 (0.4%) adverse reactions. Events resolved in 27 of the 37 patients and resulted in permanent discontinuation in 8 patients. Systemic corticosteroids were required in all patients with immune-mediated colitis, while 2 patients (2/37) required other immunosuppressants (e.g., infliximab, mycophenolate).

IMFINZI with Tremelimumab-actl

Immune-mediated colitis or diarrhea occurred in 6% (23/388) of patients receiving IMFINZI in combination with tremelimumab-actl, including Grade 3 (3.6%) adverse reactions. Events resolved in 22 of the 23 patients and resulted in permanent discontinuation in 5 patients. All patients received systemic corticosteroids, and 20 of the 23 patients received high-dose corticosteroid treatment (at least 40 mg prednisone or equivalent per day). Three patients also received other immunosuppressants.

Intestinal perforation has been observed in other studies of IMFINZI in combination with tremelimumab-actl.

IMFINZI with Tremelimumab-actl and Platinum-Based Chemotherapy

Immune-mediated colitis occurred in 6.5% (39/596) of patients receiving IMFINZI in combination with tremelimumab-actl including fatal (0.2%) and Grade 3 (2.5%) adverse reactions. Events resolved in 33 of 39 patients and resulted in permanent discontinuation in 11 patients. Systemic corticosteroids were required in all patients with immune-mediated colitis, while 4 patients (4/39) required other corticosteroids.

Intestinal perforation and large intestine perforation were reported in 0.1% of patients receiving IMFINZI in combination with tremelimumab-actl.

Immune-Mediated Hepatitis

IMFINZI can cause immune-mediated hepatitis.

IMFINZI as a Single Agent

Immune-mediated hepatitis occurred in 2.8% (52/1889) of patients receiving IMFINZI, including fatal (0.2%), Grade 4 (0.3%) and Grade 3 (1.4%) adverse reactions. Events resolved in 21 of the 52 patients and resulted in permanent discontinuation of IMFINZI in 6 patients. Systemic corticosteroids were required in all patients with immune-mediated hepatitis, while 2 patients (2/52) required use of mycophenolate with high-dose steroids.

IMFINZI with Tremelimumab-actl

Immune-mediated hepatitis occurred in 7.5% (29/388) of patients receiving IMFINZI in combination with tremelimumab-actl, including fatal (0.8%), Grade 4 (0.3%), and Grade 3 (4.1%) adverse reactions. Events resolved in 12 of the 29 patients and resulted in permanent discontinuation in 9 patients. Systemic corticosteroids were required in all 29 patients and all 29 patients required high-dose corticosteroid treatment (at least 40 mg prednisone or equivalent per day). Eight patients (8/29) required other immunosuppressants.

IMFINZI with Tremelimumab-actl and Platinum-Based Chemotherapy

Immune-mediated hepatitis occurred in 3.9% (23/596) of patients receiving IMFINZI in combination with tremelimumab-actl, including fatal (0.3%), Grade 4 (0.5%), and Grade 3 (2.0%) adverse reactions. Events resolved in 12 of the 23 patients and resulted in permanent discontinuation in 10 patients. Systemic corticosteroids were required in all patients with immune-mediated hepatitis, while 2 patients (2/23) required use of other immunosuppressants.

Immune-Mediated Endocrinopathies

Adrenal Insufficiency

IMFINZI can cause primary or secondary adrenal insufficiency. For Grade 2 or higher adrenal insufficiency, initiate symptomatic treatment, including hormone replacement as clinically indicated. Withhold or permanently discontinue IMFINZI based on the severity [see Dosage and Administration (2.3)].

IMFINZI as a Single Agent

Immune-mediated adrenal insufficiency occurred in 0.5% (9/1889) of patients receiving IMFINZI, including Grade 3 (< 0.1%) adverse reactions. Events resolved in 1 of the 9 patients and did not lead to permanent discontinuation of IMFINZI in any patients. Systemic corticosteroids were required in all patients with adrenal insufficiency; of these, the majority remained on systemic corticosteroids.

IMFINZI with Tremelimumab-actl

Immune-mediated adrenal insufficiency occurred in 1.5% (6/388) of patients receiving IMFINZI in combination with tremelimumab-actl, including Grade 3 (0.3%) adverse reactions. Events resolved in 2 of the 6 patients. Systemic corticosteroids were required in all 6 patients, and of these, 1 patient required high-dose corticosteroid treatment (at least 40 mg prednisone or equivalent per day).

IMFINZI with Tremelimumab-actl and Platinum-Based Chemotherapy

Immune-mediated adrenal insufficiency occurred in 2.2% (13/596) of patients receiving IMFINZI in combination with tremelimumab-actl, including Grade 3 (0.8%) adverse reactions. Events resolved in 2 of the 13 patients and resulted in permanent discontinuation in 1 patient. Systemic corticosteroids were required in all patients with adrenal insufficiency. One patient also required endocrine therapy.

Hypophysitis

IMFINZI can cause immune-mediated hypophysitis. Hypophysitis can present with acute symptoms associated with mass effect such as headache, photophobia, or visual field cuts. Hypophysitis can cause hypopituitarism. Initiate symptomatic treatment including hormone replacement as clinically indicated. Withhold or permanently discontinue IMFINZI depending on severity [see Dosage and Administration (2.3)].

IMFINZI as a Single Agent

Grade 3 hypophysitis/hypopituitarism occurred in < 0.1% (1/1889) of patients who received IMFINZI. Treatment with systemic corticosteroids was administered in this patient. The event did not lead to permanent discontinuation of IMFINZI.

IMFINZI with Tremelimumab-actl

Immune-mediated hypophysitis/hypopituitarism occurred in 1% (4/388) of patients receiving IMFINZI in combination with tremelimumab-actl. Events resolved in 2 of the 4 patients. Systemic corticosteroids were required in 3 patients, and of these, 1 patient received high-dose corticosteroid treatment (at least 40 mg prednisone or equivalent per day). Two patients also required endocrine therapy.

IMFINZI with Tremelimumab-actl and Platinum-Based Chemotherapy

Immune-mediated hypophysitis occurred in 1.3% (8/596) of patients receiving IMFINZI in combination with tremelimumab-actl, including Grade 3 (0.5%) adverse reactions. Events resulted in permanent discontinuation in 1 patient. Systemic corticosteroids were required in 6 patients with immune-mediated hypophysitis; of these, 2 of the 8 patients received high-dose corticosteroid treatment (at least 40 mg prednisone or equivalent per day). Four patients also required endocrine therapy.

Thyroid Disorders

IMFINZI can cause immune-mediated thyroid disorders. Thyroiditis can present with or without endocrinopathy. Hypothyroidism can follow hyperthyroidism. Initiate hormone replacement therapy for hypothyroidism or institute medical management of hyperthyroidism as clinically indicated. Withhold or discontinue IMFINZI based on the severity [see Dosage and Administration (2.3)].

Thyroiditis

IMFINZI as a Single Agent

Immune-mediated thyroiditis occurred in 0.5% (9/1889) of patients receiving IMFINZI, including Grade 3 (< 0.1%) adverse reactions. Events resolved in 4 of the 9 patients and resulted in permanent discontinuation in 1 patient. Systemic corticosteroids were required in 3 patients (3/9) with immune-mediated thyroiditis, while 8 patients (8/9) required endocrine therapy.

IMFINZI with Tremelimumab-actl

Immune-mediated thyroiditis occurred in 1.5% (6/388) of patients receiving IMFINZI in combination with tremelimumab-actl. Events resolved in 2 of the 6 patients. Systemic corticosteroids were required in 2 patients (2/6) with immune-mediated thyroiditis; of these, 1 patient required high-dose corticosteroid treatment (at least 40 mg prednisone or equivalent per day). All patients required other therapy including hormone replacement therapy, thiamazole, carbimazole, propylthiouracil, perchlorate, calcium channel blocker, or beta-blocker.

IMFINZI with Tremelimumab-actl and Platinum-Based Chemotherapy

Immune-mediated thyroiditis occurred in 1.2% (7/596) of patients receiving IMFINZI in combination with tremelimumab-actl. Events resolved in 2 of the 7 patients and one resulted in permanent discontinuation. Systemic corticosteroids were required in 2 patients (2/7) with immune-mediated thyroiditis, while all patients required endocrine therapy.

Hyperthyroidism

IMFINZI as a Single Agent

Immune-mediated hyperthyroidism occurred in 2.1% (39/1889) of patients receiving IMFINZI. Events resolved in 30 of the 39 patients and did not lead to permanent discontinuation of IMFINZI in any patients. Systemic corticosteroids were required in 9 patients (9/39) with immune-mediated hyperthyroidism, while 35 patients (35/39) required endocrine therapy.

IMFINZI with Tremelimumab-actl

Immune-mediated hyperthyroidism occurred in 4.6% (18/388) of patients receiving IMFINZI in combination with tremelimumab-actl, including Grade 3 (0.3%) adverse reactions. Events resolved in 15 of the 18 patients. Two patients (2/18) required high-dose corticosteroid treatment (at least 40 mg prednisone or equivalent per day). Seventeen patients required other therapy (thiamazole, carbimazole, propylthiouracil, perchlorate, calcium channel blocker, or beta-blocker).

IMFINZI with Tremelimumab-actl and Platinum-Based Chemotherapy

Immune-mediated hyperthyroidism occurred in 5% (30/596) of patients receiving IMFINZI in combination with tremelimumab-actl, including Grade 3 (0.2%) adverse reactions. Events resolved in 21 of the 30 patients. Systemic corticosteroids were required in 5 patients (5/30) with immune-mediated hyperthyroidism, while 28 patients (28/30) required endocrine therapy.

Hypothyroidism

IMFINZI as a Single Agent

Immune-mediated hypothyroidism occurred in 8.3% (156/1889) of patients receiving IMFINZI, including Grade 3 (<0.1%) adverse reactions. Events resolved in 31 of the 156 patients and did not lead to permanent discontinuation of IMFINZI in any patients. Systemic corticosteroids were required in 11 patients (11/156) and the majority of patients (152/156) required long-term thyroid hormone replacement.

IMFINZI with Tremelimumab-actl

Immune-mediated hypothyroidism occurred in 11% (42/388) of patients receiving IMFINZI in combination with tremelimumab-actl. Events resolved in 5 of the 42 patients. One patient received high-dose corticosteroid treatment (at least 40 mg prednisone or equivalent per day). All patients required other therapy (thiamazole, carbimazole, propylthiouracil, perchlorate, calcium channel blocker, or beta-blocker).

IMFINZI with Tremelimumab-actl and Platinum-Based Chemotherapy

Immune-mediated hypothyroidism occurred in 8.6% (51/596) of patients receiving IMFINZI in combination with tremelimumab-actl, including Grade 3 (0.5%) adverse reactions. Systemic corticosteroids were required in 2 patients (2/51) and all patients required endocrine therapy.

IMFINZI with Carboplatin and Paclitaxel

Immune-mediated hypothyroidism occurred in 14% (34/235) of patients receiving IMFINZI in combination with carboplatin and paclitaxel. Events resolved in 8 of the 34 patients. Endocrine therapy was required in 34 of the 34 patients.

Type 1 Diabetes Mellitus, which can present with diabetic ketoacidosis

Monitor patients for hyperglycemia or other signs and symptoms of diabetes. Initiate treatment with insulin as clinically indicated. Withhold or permanently discontinue IMFINZI based on the severity [see Dosage and Administration (2.3)].

IMFINZI as a Single Agent

Grade 3 immune-mediated type 1 diabetes mellitus occurred in < 0.1% (1/1889) of patients receiving IMFINZI. This patient required long-term insulin therapy and IMFINZI was permanently discontinued. Two additional patients (0.1%, 2/1889) had events of hyperglycemia requiring insulin therapy that did not resolve at the time of reporting.

IMFINZI with Tremelimumab-actl

Two patients (0.5%, 2/388) had events of hyperglycemia requiring insulin therapy that had not resolved at last follow-up.

IMFINZI with Tremelimumab-actl and Platinum-Based Chemotherapy

Immune-mediated Type 1 diabetes mellitus occurred in 0.5% (3/596) of patients receiving IMFINZI in combination with tremelimumab-actl, including Grade 3 (0.3%) adverse reactions. All patients required endocrine therapy.

Immune-Mediated Nephritis with Renal Dysfunction

IMFINZI can cause immune-mediated nephritis.

IMFINZI as a Single Agent

Immune-mediated nephritis occurred in 0.5% (10/1889) of patients receiving IMFINZI, including Grade 3 (< 0.1%) adverse reactions. Events resolved in 5 of the 10 patients and resulted in permanent discontinuation in 3 patients. Systemic corticosteroids were required in all patients with immune-mediated nephritis.

IMFINZI with Tremelimumab-actl

Immune-mediated nephritis occurred in 1% (4/388) of patients receiving IMFINZI in combination with tremelimumab-actl, including Grade 3 (0.5%) adverse reactions. Events resolved in 3 of the 4 patients and resulted in permanent discontinuation in 2 patients. Systemic corticosteroids were required in all patients with immune-mediated nephritis; of these, 3 patients required high-dose corticosteroid treatment (at least 40 mg prednisone or equivalent per day).

IMFINZI with Tremelimumab-actl and Platinum-Based Chemotherapy

Immune-mediated nephritis occurred in 0.7% (4/596) of patients receiving IMFINZI in combination with tremelimumab-actl, including Grade 3 (0.2%) adverse reactions. Events resolved in 1 of the 4 patients and resulted in permanent discontinuation in 3 patients. Systemic corticosteroids were required in all patients with immune-mediated nephritis.

Immune-Mediated Dermatology Reactions

IMFINZI can cause immune-mediated rash or dermatitis. Exfoliative dermatitis, including Stevens Johnson Syndrome (SJS), drug rash with eosinophilia and systemic symptoms (DRESS), and toxic epidermal necrolysis (TEN), has occurred with PD-1/L-1 blocking antibodies. Topical emollients and/or topical corticosteroids may be adequate to treat mild to moderate non-exfoliative rashes. Withhold or permanently discontinue IMFINZI depending on severity [see Dosage and Administration (2.3)].

IMFINZI as a Single Agent

Immune-mediated rash or dermatitis occurred in 1.8% (34/1889) of patients receiving IMFINZI, including Grade 3 (0.4%) adverse reactions. Events resolved in 19 of the 34 patients and resulted in permanent discontinuation in 2 patients. Systemic corticosteroids were required in all patients with immune-mediated rash or dermatitis.

IMFINZI with Tremelimumab-actl

Immune-mediated rash or dermatitis occurred in 4.9% (19/388) of patients receiving IMFINZI in combination with tremelimumab-actl, including Grade 4 (0.3%) and Grade 3 (1.5%) adverse reactions. Events resolved in 13 of the 19 patients and resulted in permanent discontinuation in 2 patients. Systemic corticosteroids were required in all patients with immune-mediated rash or dermatitis; of these, 12 patients required high-dose corticosteroid treatment (at least 40 mg prednisone or equivalent per day). One patient received other immunosuppressants.

IMFINZI with Tremelimumab-actl and Platinum-Based Chemotherapy

Immune-mediated rash or dermatitis occurred in 7.2% (43/596) of patients receiving IMFINZI in combination with tremelimumab-actl, including Grade 3 (0.3%) adverse reactions. Events resolved in 32 of the 43 patients and resulted in permanent discontinuation in 2 patients. Systemic corticosteroids were required in all patients with immune-mediated rash or dermatitis.

Immune-Mediated Pancreatitis

IMFINZI in combination with tremelimumab-actl can cause immune-mediated pancreatitis.

IMFINZI with Tremelimumab-actl

Immune-mediated pancreatitis occurred in 2.3% (9/388) of patients receiving IMFINZI in combination with tremelimumab-actl, including Grade 4 (0.3%) and Grade 3 (1.5%) adverse reactions. Events resolved in 6 of the 9 patients. Systemic corticosteroids were required in all 9 patients, and of these 7 patients required high-dose corticosteroid treatment (at least 40 mg prednisone or equivalent per day).

Other Immune-Mediated Adverse Reactions

The following clinically significant, immune-mediated adverse reactions occurred at an incidence of less than 1% each in patients who received IMFINZI or IMFINZI in combination with tremelimumab-actl, or were reported with the use of other PD-1/PD-L1 blocking antibodies.

Cardiac/vascular: Myocarditis, pericarditis, vasculitis.

Nervous system: Meningitis, encephalitis, myelitis and demyelination, myasthenic syndrome/myasthenia gravis (including exacerbation), Guillain-Barré syndrome, nerve paresis, autoimmune neuropathy.

Ocular: Uveitis, iritis, and other ocular inflammatory toxicities can occur. Some cases can be associated with retinal detachment. Various grades of visual impairment to include blindness can occur. If uveitis occurs in combination with other immune-mediated adverse reactions, consider a Vogt-Koyanagi-Harada-like syndrome, as this may require treatment with systemic steroids to reduce the risk of permanent vision loss.

Gastrointestinal: Pancreatitis including increases in serum amylase and lipase levels, gastritis, duodenitis.

Musculoskeletal and connective tissue disorders: Myositis/polymyositis, rhabdomyolysis and associated sequelae including renal failure, arthritis, polymyalgia rheumatic.

Endocrine: Hypoparathyroidism.

Other (hematologic/immune): Hemolytic anemia, aplastic anemia, hemophagocytic lymphohistiocytosis, systemic inflammatory response syndrome, histiocytic necrotizing lymphadenitis (Kikuchi lymphadenitis), sarcoidosis, immune thrombocytopenia, solid organ transplant rejection, other transplant (including corneal graft) rejection.

5.2 Infusion-Related Reactions

IMFINZI can cause severe or life-threatening infusion-related reactions.

Monitor for signs and symptoms of infusion-related reactions. Interrupt, slow the rate of, or permanently discontinue IMFINZI based on the severity [see Dosage and Administration (2.3)]. For Grade 1 or 2 infusion-related reactions, consider using pre-medications with subsequent doses.

IMFINZI as a Single Agent

Infusion-related reactions occurred in 2.2% (42/1889) of patients receiving IMFINZI, including Grade 3 (0.3%) adverse reactions.

IMFINZI in Combination with Tremelimumab-actl

Infusion-related reactions occurred in 2.6% (10/388) of patients receiving IMFINZI in combination with tremelimumab-actl.

IMFINZI with Tremelimumab-actl and Platinum-Based Chemotherapy

Infusion-related reactions occurred in 2.9% (17/596) of patients receiving IMFINZI in combination with tremelimumab-actl, including Grade 3 (0.3%) adverse reactions.

5.3 Complications of Allogeneic HSCT after IMFINZI

Fatal and other serious complications can occur in patients who receive allogeneic hematopoietic stem cell transplantation (HSCT) before or after being treated with a PD-1/L-1 blocking antibody. Transplant-related complications include hyperacute graft-versus-host-disease (GVHD), acute GVHD, chronic GVHD, hepatic veno-occlusive disease (VOD) after reduced intensity conditioning, and steroid-requiring febrile syndrome (without an identified infectious cause). These complications may occur despite intervening therapy between PD-1/L-1 blockade and allogeneic HSCT.

Follow patients closely for evidence of transplant-related complications and intervene promptly. Consider the benefit versus risks of treatment with a PD-1/L-1 blocking antibody prior to or after an allogeneic HSCT.

5.4 Embryo-Fetal Toxicity

Based on its mechanism of action and data from animal studies, IMFINZI can cause fetal harm when administered to a pregnant woman. In animal reproduction studies, administration of durvalumab to cynomolgus monkeys from the onset of organogenesis through delivery resulted in increased premature delivery, fetal loss and premature neonatal death. Advise pregnant women of the potential risk to a fetus. Advise females of reproductive potential to use effective contraception during treatment with IMFINZI and for 3 months after the last dose of IMFINZI [see Use in Specific Populations (8.1, 8.3)].

6 ADVERSE REACTIONS

The following adverse reactions are discussed in greater detail in other sections of the labeling.

- Immune-Mediated Adverse Reactions [see Warnings and Precautions (5.1)].
- Infusion-Related Reactions [see Warnings and Precautions (5.2)].

6.1 Clinical Trials Experience

Because clinical trials are conducted under widely varying conditions, adverse reaction rates observed in the clinical trials of a drug cannot be directly compared to rates in the clinical trials of another drug and may not reflect the rates observed in practice.

The data described in the WARNINGS AND PRECAUTIONS section reflect exposure to IMFINZI as a single agent in a total of 1,889 patients enrolled in the PACIFIC study (a randomized, placebo-controlled study that enrolled 475 patients with unresectable Stage III NSCLC), Study 1108 (an open-label, single-arm, multicohort study that enrolled 970 patients with advanced solid tumors), and an additional open-label, single-arm study (ATLANTIC Study) that enrolled 444 patients with advanced solid tumors, including NSCLC. In these studies, IMFINZI was administered at a dose of 10 mg/kg every 2 weeks. Among the 1889 patients, 38% were exposed for 6 months or more and 18% were exposed for 12 months or more. The data also reflect exposure to IMFINZI 1,500 mg every 4 weeks as a single agent in 262 patients from the ADRIATIC study (a randomized, double-blind study in patients with LS-SCLC) and to IMFINZI in combination with chemotherapy in 265 patients from the CASPIAN study (a randomized, open-label study in patients with ES-SCLC) and in 338 patients from the TOPAZ-1 study (a randomized, double-blind study in patients with BTC). In the CASPIAN and TOPAZ-1 studies, IMFINZI was administered at a dose of 1,500 mg every 3 or 4 weeks.

The data also reflect exposure to IMFINZI 1,120 mg in combination with carboplatin and paclitaxel (every 3 weeks for up to 6 cycles) followed by IMFINZI 1,500 mg (every 4 weeks) as a single agent in 235 patients in DUO-E (a randomized, placebo-controlled trial in endometrial cancer). Among the 235 patients, 77% (181 patients) were exposed to IMFINZI for 6 months or more and 41% (96 patients) for 12 months or more.

The data also reflect exposure to IMFINZI 1,500 mg in combination with tremelimumab-actl 300 mg in 388 patients in HIMALAYA. In the HIMALAYA study patients received IMFINZI 1,500 mg in combination with tremelimumab-actl as a single intravenous infusion of 300 mg, followed by IMFINZI 1,500 mg every 4 weeks. The pooled safety population (N = 596) described in the WARNINGS AND PRECAUTIONS section reflect exposure to IMFINZI 1,500 mg in combination with tremelimumab-actl 75 mg and histology-based platinum chemotherapy regimens in 330 patients in POSEIDON [see Clinical Studies (14.1)], and 266 patients with ES-SCLC in CASPIAN who received up to four cycles of platinum-etoposide plus IMFINZI 1,500 mg with tremelimumab-actl 75 mg every 3 weeks, followed by IMFINZI 1,500 mg every 4 weeks (an unapproved regimen for extensive stage small cell lung cancer). Among the 596 patients, 55% were exposed to IMFINZI for 6 months or more and 24% were exposed for 12 months or more.

The data described in this section reflect exposure to IMFINZI in patients with unresectable Stage III NSCLC enrolled in the PACIFIC study, in patients with metastatic NSCLC enrolled in the POSEIDON study, in patients with LS-SCLC enrolled in the ADRIATIC study, in patients with ES-SCLC enrolled in the CASPIAN study, in patients with BTC enrolled in the TOPAZ‑1 study, in patients with uHCC included in the HIMALAYA study, in patients with dMMR endometrial cancer enrolled in the DUO-E study, in patients with resectable NSCLC enrolled in the AEGEAN study, in patients with MIBC enrolled in the NIAGARA study and in patients with resectable GC/GEJC enrolled in the MATTERHORN study.

Non-Small Cell Lung Cancer

Neoadjuvant and Adjuvant Treatment of Resectable NSCLC – AEGEAN

The safety of IMFINZI in combination with neoadjuvant platinum-containing chemotherapy followed by surgery, and continued adjuvant treatment with IMFINZI as a single agent after surgery, was investigated in AEGEAN, a randomized, double-blind, placebo-controlled, multicenter study for patients with resectable NSCLC (Stage IIA to select Stage IIIB [AJCC, 8th edition]); squamous or non-squamous) [see Clinical Studies (14.1)].

Safety data are available for the 799 patients who received IMFINZI in combination with chemotherapy (n=401) or placebo in combination with chemotherapy (n=398).

The median duration of exposure to IMFINZI 1,500 mg every 3 weeks in the neoadjuvant phase was 12 weeks (range: 0 to 19 weeks). The median duration of exposure to IMFINZI 1,500 mg every 4 weeks in the adjuvant phase was 37 weeks (range: 4 to 67 weeks). The median age of patients who received IMFINZI was 65 years (range: 30 to 88), 52% age 65 or older, 12% age 75 or older; 65% male; 54% White, 41% Asian, 1% Black, 3% Other races; and 17% Hispanic or Latino.

The most common adverse reactions (occurring in ≥ 20% of patients) were anemia, nausea, constipation, fatigue, musculoskeletal pain, and rash.

Table 5 summarizes the adverse reactions that occurred in (≥ 10%) patients treated with IMFINZI in combination with chemotherapy.

Table 5. Adverse Reactions Occurring in ≥ 10% of Patients in the AEGEAN Study
Adverse Reaction | IMFINZI with Chemotherapy; N=401 |  | Placebo with Chemotherapy; N=398
Adverse Reaction | All Grades (%) | Grade 3 or 4 (%) | All Grades (%) | Grade 3 or 4 (%)
Gastrointestinal disorders
Nausea | 25 | 0.2 | 29 | 0.3
Constipation | 25 | 0.2 | 21 | 0
Diarrhea [includes colitis, diarrhea, enteritis, and proctitis.] | 14 | 1 | 13 | 1.3
Vomiting | 11 | 0.7 | 11 | 1.0
General disorders and administration site conditions
Fatigue [includes fatigue and asthenia.] | 25 | 0 | 25 | 1.5
Skin and subcutaneous tissue disorders
Rash [includes dermatitis, dermatitis acneiform, drug eruption, eczema, eczema asteatotic, erythema, palmar‑erythrodysaesthesia syndrome, pemphigoid, rash, rash erythematous, rash macular, rash maculo-papular, rash papular, rash pruritic, and rash pustular, skin exfoliation, and urticarial dermatitis.] | 22 | 0.5 | 14 | 0.3
Pruritus | 12 | 0.2 | 6 | 0
Musculoskeletal and connective tissue disorders
Musculoskeletal pain [includes arthralgia, arthritis, back pain, bone pain, chest pain, musculoskeletal chest pain, musculoskeletal pain, musculoskeletal discomfort, musculoskeletal stiffness,myalgia, neck pain, non-cardiac chest pain, pain in extremity, and spinal pain.] | 24 | 1 | 29 | 0.5
Metabolism and nutrition disorders
Decreased appetite | 18 | 0.2 | 18 | 0.3
Nervous system disorders
Peripheral neuropathy [includes dysaesthesia, hypoaesthesia, neuralgia, neuropathy peripheral, paraesthesia, peripheral sensory neuropathy, and polyneuropathy.] | 16 | 0.5 | 22 | 0.8
Endocrine disorders
Hypothyroidism [includes blood thyroid stimulating hormone increased and hypothyroidism.] | 11 | 0 | 3.8 | 0
Respiratory, thoracic and mediastinal disorders
Cough / Productive cough | 11 | 0 | 13 | 0
Pneumonia [includes lower respiratory tract infection, lung abscess, paracancerous pneumonia, pneumonia, pneumonia aspiration, pneumonia bacterial, pneumonia chlamydial, pneumonia cryptococcal, pneumonia fungal, pneumonia pseudomonal, pneumonia streptococcal, pneumonia viral, and post-procedural pneumonia.] , [Five Grade 5 events in the IMFINZI arm and four Grade 5 events in the Placebo arm.] | 11 | 3.5 | 10 | 3
COVID-19 [Includes COVID-19 and COVID-19 Pneumonia. Five Grade 5 events in the IMFINZI arm and One Grade 5 event in the placebo arm.] | 11 | 0.2 | 9 | 0.8
Psychiatric Disorders
Insomnia | 10 | 0 | 12 | 0

Table 6 summarizes the laboratory abnormalities in patients treated with IMFINZI in combination with chemotherapy.

Table 6. Select Laboratory Abnormalities (≥20%) That Worsened from Baseline in Patients with Disease Who Received IMFINZI with Chemotherapy in AEGEAN
Laboratory Abnormality [Graded per NCI CTCAE V5.] | IMFINZI with Chemotherapy [The denominator used to calculate the rate varied from 349 to 399 based on the number of patients with a baseline value and at least one post-treatment value.] |  | Placebo with; Chemotherapy [The denominator used to calculate the rate varied from 333 to 398 based on the number of patients with a baseline value and at least one post-treatment value.]
Laboratory Abnormality [Graded per NCI CTCAE V5.] | All Grades; (%) | Grade; 3 or 4; (%) | All; Grades; (%) | Grade; 3 or 4; (%)
Hematology
Hemoglobin decreased | 78 | 10 | 75 | 9
Leukocytes decreased | 63 | 12 | 64 | 11
Neutrophils decreased | 52 | 24 | 56 | 27
Platelets decreased | 46 | 7 | 44 | 8
Lymphocytes decreased | 41 | 11 | 37 | 9
Chemistry
Calcium corrected, decreased | 51 | 3.3 | 52 | 4.5
Alanine aminotransferase increased | 49 | 6 | 42 | 2
Aspartate aminotransferase increased | 47 | 3.5 | 37 | 1.8
Potassium increased | 33 | 1.5 | 29 | 2
Sodium decreased | 35 | 5 | 33 | 6
Gamma glutamyl transferase increased | 36 | 4.7 | 35 | 2.1
Creatinine increased | 32 | 2.3 | 27 | 3.3
Amylase increased | 25 | 4.7 | 24 | 3.6
Magnesium decreased | 22 | 2.8 | 20 | 3.6
Lipase increased | 23 | 4.9 | 24 | 7

Neoadjuvant Phase of AEGEAN

A total of 401 patients received at least 1 dose of IMFINZI in combination with platinum-containing chemotherapy as neoadjuvant treatment and 398 patients received at least 1 dose of placebo in combination with platinum-containing chemotherapy as neoadjuvant treatment.

Serious adverse reactions occurred in 21% of patients who received IMFINZI in combination with platinum-containing chemotherapy as neoadjuvant treatment; the most frequent (≥1%) serious adverse reactions were pneumonia (2.7%), anemia (1.5%), myelosuppression (1.5%), vomiting (1.2%), neutropenia (1%), and acute kidney injury (1%). Fatal adverse reactions occurred in 2% of patients, including death due to COVID-19 pneumonia (0.5%), sepsis (0.5%), myocarditis (0.2%), decreased appetite (0.2%), hemoptysis (0.2%), and death not otherwise specified (0.2%).

Permanent discontinuation of any study drug due to an adverse reaction occurred in 14% of patients who received IMFINZI in combination with platinum-containing chemotherapy as neoadjuvant treatment; the most frequent (>0.5%) adverse reactions that led to permanent discontinuation of any study drug were anemia (1.5%), neutropenia (0.7%), myelosuppression (0.7%), and periphery sensory neuropathy (0.7%). Permanent discontinuation of IMFINZI due to an adverse reaction occurred in 6.7% of patients who received IMFINZI in combination with platinum-containing chemotherapy as neoadjuvant treatment; the most frequent (≥0.5%) adverse reactions that led to permanent discontinuation of IMFINZI were peripheral sensory neuropathy (0.7%) and pneumonitis (0.5%).

Of the 401 IMFINZI-treated patients and 398 placebo-treated patients who received neoadjuvant treatment, 1.7% (n=7) and 1% (n=4), respectively, did not receive surgery due to adverse reactions. Adverse reactions that led to cancellation of surgery in the IMFINZI arm were COVID-19 pneumonia, HIV infection, pneumonitis, prostate cancer, colon cancer, pruritus, and colitis.

Of the 325 IMFINZI-treated patients who received surgery, 4% (n=15) experienced delay of surgery (a surgical delay is defined as on-study surgery occurring more than 40 days after the last dose of study treatment in the neoadjuvant period) due to adverse reactions. Of the 326 placebo-treated patients who received surgery, 4% (n=16) experienced delay of surgery due to adverse reactions.

Of the 325 IMFINZI-treated patients who received surgery, 6.5% (n=21) did not receive adjuvant treatment due to adverse reactions. Of the 326 placebo-treated patients who received surgery, 5.8% (n=19) did not receive adjuvant treatment due to adverse reactions.

Adjuvant Phase of AEGEAN

A total of 265 patients in the IMFINZI arm and 254 patients in the placebo arm received at least 1 dose of adjuvant treatment.

Of the patients who received single agent IMFINZI as adjuvant treatment, 13% experienced serious adverse reactions. The most frequent serious adverse reactions reported in >1% of patients were pneumonia (1.9%), pneumonitis (1.1%), and COVID-19 (1.1%). Four fatal adverse reactions occurred during the adjuvant phase of the study, including COVID-19 pneumonia, pneumonia aspiration, interstitial lung disease and aortic aneurysm. Permanent discontinuation of adjuvant IMFINZI due to an adverse reaction occurred in 8% of patients. The most frequent (≥0.5%) adverse reaction that led to permanent discontinuation of adjuvant IMFINZI was pneumonitis (1.1%) and rash (0.8%).

Unresectable Stage III NSCLC - PACIFIC

The safety of IMFINZI in patients with Stage III NSCLC who completed concurrent platinum-based chemoradiotherapy within 42 days prior to initiation of study drug was evaluated in the PACIFIC study, a multicenter, randomized, double-blind, placebo-controlled study. A total of 475 patients received IMFINZI 10 mg/kg intravenously every 2 weeks. The study excluded patients who had disease progression following chemoradiation, with active or prior autoimmune disease within 2 years of initiation of the study or with medical conditions that required systemic immunosuppression [see Clinical Studies (14.1)].

The study population characteristics were: median age of 64 years (range: 23 to 90), 45% age 65 years or older, 70% male, 69% White, 27% Asian, 75% former smoker, 16% current smoker, and 51% had WHO performance status (PS) of 1. All patients received definitive radiotherapy as per protocol, of which 92% received a total radiation dose of 54 Gy to 66 Gy. The median duration of exposure to IMFINZI was 10 months (range: 0.2 to 12.6).

IMFINZI was discontinued due to adverse reactions in 15% of patients. The most common adverse reactions leading to IMFINZI discontinuation were pneumonitis or radiation pneumonitis in 6% of patients. Serious adverse reactions occurred in 29% of patients receiving IMFINZI. The most frequent serious adverse reactions reported in at least 2% of patients were pneumonitis or radiation pneumonitis (7%) and pneumonia (6%). Fatal pneumonitis or radiation pneumonitis and fatal pneumonia occurred in < 2% of patients and were similar across arms. The most common adverse reactions (occurring in ≥ 20% of patients) were cough, fatigue, pneumonitis or radiation pneumonitis, upper respiratory tract infections, dyspnea, and rash.

Table 7 summarizes the adverse reactions that occurred in at least 10% of patients treated with IMFINZI.

Table 7. Adverse Reactions Occurring in ≥ 10% of Patients in the PACIFIC Study
 | IMFINZI; N = 475 |  | Placebo; N = 234
Adverse Reaction | All Grades; (%) | Grades 3-4; (%) | All Grades; (%) | Grades 3-4; (%)
Respiratory, Thoracic, and Mediastinal Disorders
Cough/Productive Cough | 40 | 0.6 | 30 | 0.4
Pneumonitis [Includes acute interstitial pneumonitis, interstitial lung disease, pneumonitis, pulmonary fibrosis.] /Radiation Pneumonitis | 34 | 3.4 | 25 | 3
Dyspnea [Includes dyspnea, and exertional dyspnea.] | 25 | 1.5 | 25 | 2.6
General Disorders
Fatigue [Includes asthenia and fatigue.] | 34 | 0.8 | 32 | 1.3
Pyrexia | 15 | 0.2 | 9 | 0
Infections
Upper respiratory tract infections [Includes laryngitis, nasopharyngitis, peritonsillar abscess, pharyngitis, rhinitis, sinusitis, tonsillitis, tracheobronchitis, and upper respiratory tract infection.] | 26 | 0.4 | 19 | 0
Pneumonia [Includes lung infection, pneumocystis jirovecii pneumonia, pneumonia, pneumonia adenoviral, pneumonia bacterial, pneumonia cytomegaloviral, pneumonia haemophilus, pneumonia klebsiella, pneumonia necrotizing, pneumonia pneumococcal, and pneumonia streptococcal.] | 17 | 7 | 12 | 6
Skin and Subcutaneous Tissue Disorders
Rash [Includes rash erythematous, rash generalized, rash macular, rash maculopapular, rash papular, rash pruritic, rash pustular, erythema, eczema, rash, and dermatitis.] | 23 | 0.6 | 12 | 0
Pruritus [Includes pruritus generalized and pruritus.] | 12 | 0 | 6 | 0
Gastrointestinal Disorders
Diarrhea | 18 | 0.6 | 19 | 1.3
Abdominal pain [Includes abdominal pain, abdominal pain lower, abdominal pain upper, and flank pain.] | 10 | 0.4 | 6 | 0.4
Endocrine Disorders
Hypothyroidism [Includes autoimmune hypothyroidism and hypothyroidism.] | 12 | 0.2 | 1.7 | 0

Other adverse reactions occurring in less than 10% of patients treated with IMFINZI were dysphonia, dysuria, night sweats, peripheral edema, and increased susceptibility to infections.

Table 8 summarizes the laboratory abnormalities that occurred in at least 20% of patients treated with IMFINZI.

Table 8. Laboratory Abnormalities Worsening from Baseline Occurring in ≥ 20% of Patients in the PACIFIC Study
 | IMFINZI |  | Placebo
Laboratory Abnormality | All Grades [Graded according to NCI CTCAE version 4.0.]; (%) [Each test incidence is based on the number of patients who had both baseline and at least one on-study laboratory measurement available: IMFINZI (range: 464 to 470) and placebo (range: 224 to 228).] | Grade 3 or 4; (%) | All Grades; (%) | Grade 3 or 4; (%)
Chemistry
Hyperglycemia | 52 | 8 | 51 | 8
Hypocalcemia | 46 | 0.2 | 41 | 0
Increased ALT | 39 | 2.3 | 22 | 0.4
Increased AST | 36 | 2.8 | 21 | 0.4
Hyponatremia | 33 | 3.6 | 30 | 3.1
Hyperkalemia | 32 | 1.1 | 29 | 1.8
Increased GGT | 24 | 3.4 | 22 | 1.7
Hematology
Lymphopenia | 43 | 17 | 39 | 18

Metastatic NSCLC - POSEIDON

The safety of IMFINZI in combination with tremelimumab-actl and platinum-based chemotherapy in patients with metastatic NSCLC was evaluated in POSEIDON (NCT03164616), a randomized, open-label, multicenter, active-controlled study. A total of 330 patients received IMFINZI 1,500 mg in combination with tremelimumab-actl (≥ 30 kg body weight received 75 mg and < 30 kg body weight received 1 mg/kg) and histology-based platinum chemotherapy regimens [see Clinical Studies (14.1)]. Of these patients, 66% received the maximum 5 doses of tremelimumab-actl and 79% received at least 4 doses. Treatment was continued with IMFINZI as a single agent (or with IMFINZI and histologically-based pemetrexed for non-squamous patients based on the investigator’s decision) until disease progression or unacceptable toxicity. The study excluded patients with active or prior autoimmune disease or with medical conditions that required systemic corticosteroids or immunosuppressants [see Clinical Studies (14.1)].

The median age of patients who received IMFINZI in combination with tremelimumab-actl and platinum-based chemotherapy was 63 years (range: 27 to 87); 80% male; 61% White, 29% Asian, 58% former smoker, 25% current smoker, and 68% ECOG performance of 1.

Serious adverse reactions occurred in 44% of patients receiving IMFINZI in combination with tremelimumab-actl and platinum-based chemotherapy. The most frequent serious adverse reactions reported in at least 2% of patients were pneumonia (11%), anemia (5%), diarrhea (2.4%), thrombocytopenia (2.4%), pyrexia (2.4%), and febrile neutropenia (2.1%). Fatal adverse reactions occurred in a total of 4.2% of patients receiving IMFINZI in combination with tremelimumab-actl and platinum-based chemotherapy. These include hepatitis, nephritis, myocarditis, pancreatitis (all in the same patient), death (2 patients), sepsis (2 patients), pneumonitis (2 patients), acute kidney injury (2 patients), febrile neutropenia (1 patient), chronic obstructive pulmonary disease (COPD) (1 patient), dyspnea (1 patient), sudden death (1 patient), and ischemic stroke (1 patient).

Permanent discontinuation of IMFINZI or tremelimumab-actl due to an adverse reaction occurred in 17% of the patients. Adverse reactions which resulted in permanent discontinuation of IMFINZI or tremelimumab-actl in > 2% of patients included pneumonia.

Dosage interruption or delay of IMFINZI and tremelimumab-actl due to an adverse reaction occurred in 41% of patients. Adverse reactions which required dosage interruption or delay of IMFINZI and tremelimumab-actl in > 1% of patients included anemia, leukopenia/white blood cell count decreased, pneumonia, pneumonitis, colitis, diarrhea, hepatitis, rash, asthenia, amylase increased, alanine aminotransferase increased, aspartate aminotransferase increased, lipase increased, neutropenia/ neutrophil count decreased, and thrombocytopenia/platelet count decreased.

The most common adverse reactions (occurring in ≥ 20% of patients) were nausea, fatigue, musculoskeletal pain, decreased appetite, rash, and diarrhea. Grade 3 or 4 laboratory abnormalities (≥ 10%) were neutropenia, anemia, leukopenia, lymphocytopenia, lipase increased, hyponatremia and thrombocytopenia.

Table 9 summarizes the adverse reactions in POSEIDON.

Table 9. Adverse Reactions (≥ 10%) in Patients with NSCLC Who Received IMFINZI in the POSEIDON Study
 | IMFINZI with tremelimumab-actl and platinum-based chemotherapy; N = 330 |  | Platinum-based chemotherapy; N = 333
Adverse Reaction | All Grades (%) | Grade 3 or 4 (%) | All Grades (%) | Grade 3 or 4 (%)
Gastrointestinal disorders
Nausea | 42 | 1.8 | 37 | 2.1
Diarrhea | 22 | 1.5 | 15 | 1.5
Constipation | 19 | 0 | 24 | 0.6
Vomiting | 18 | 1.2 | 14 | 1.5
Stomatitis [Includes mucosal inflammation and stomatitis.] | 10 | 0 | 6 | 0.3
General disorders and administration site conditions
Fatigue/Asthenia [Includes asthenia and fatigue.] | 36 | 5 | 32 | 4.5
Pyrexia [Includes body temperature increased, hyperpyrexia, hyperthermia, and pyrexia.] | 19 | 0 | 8 | 0
Edema [Includes face edema, localized edema, and edema peripheral.] | 10 | 0 | 10 | 0.6
Musculoskeletal and connective tissue disorders
Musculoskeletal Pain [Includes arthralgia, arthritis, back pain, bone pain, musculoskeletal chest pain, musculoskeletal pain, myalgia, neck pain, non-cardiac chest pain, and spinal pain.] | 29 | 0.6 | 22 | 1.5
Metabolism and nutrition disorders
Decreased appetite | 28 | 1.5 | 25 | 1.2
Skin and subcutaneous tissue disorders
Rash [Includes eczema, erythema, dermatitis, drug eruption, erythema multiforme, pemphigoid, rash, rash maculo-papular, rash papular, rash pruritic, and rash pustular.] | 27 | 2.4 | 10 | 0.6
Pruritus | 11 | 0 | 4.5 | 0
Alopecia | 10 | 0 | 6 | 0
Infections and Infestations
Pneumonia [Includes lower respiratory tract infection, pneumocystis jirovecii pneumonia, pneumonia, pneumonia aspiration, and pneumonia bacterial.] | 17 | 8 | 12 | 4.2
Upper respiratory tract infections [Includes laryngitis, nasopharyngitis, pharyngitis, rhinitis, sinusitis, tonsillitis, tracheobronchitis and upper respiratory tract infection.] | 15 | 0.6 | 9 | 0.9
Endocrine disorders
Hypothyroidism [Includes blood thyroid stimulating hormone increased and hypothyroidism.] | 13 | 0 | 2.1 | 0
Respiratory, thoracic and mediastinal disorders
Cough/Productive Cough [Includes cough and productive cough.] | 12 | 0 | 8 | 0.3
Nervous system disorders
Headache [Includes headache and migraine.] | 11 | 0 | 8 | 0.6

Table 10 summarizes the laboratory abnormalities in POSEIDON.

Table 10. Select Laboratory Abnormalities (≥ 10%) That Worsened from Baseline in Patients with NSCLC Who Received IMFINZI in the POSEIDON Study
Laboratory Abnormality [Graded according to NCI CTCAE version 4.03.] | IMFINZI with tremelimumab-actl and platinum-based chemotherapy [The denominator used to calculate the rate varied from 45 to 326 based on the number of patients with a baseline value and at least one post-treatment value.] |  | Platinum-based chemotherapy [The denominator used to calculate the rate varied from 43 to 323 based on the number of patients with a baseline value and at least one post-treatment value.]
Laboratory Abnormality [Graded according to NCI CTCAE version 4.03.] | All Grades; (%) | Grade 3 or 4; (%) | All Grades; (%) | Grade 3 or 4; (%)
Chemistry
Blood creatinine increased | 89 | 4 | 83 | 1.9
Increased ALT | 64 | 6 | 56 | 4.7
Increased AST | 63 | 5 | 55 | 2.2
Hypocalcemia | 58 | 0.9 | 49 | 0.9
Hyponatremia | 55 | 13 | 50 | 11
Hyperkalemia | 49 | 2.2 | 35 | 2.8
Hyperglycemia | 42 | 6 | 37 | 3.1
Amylase increased | 41 | 9 | 25 | 6
Gamma Glutamyl Transferase increased | 38 | 2.2 | 35 | 4.7
Lipase increased | 35 | 14 | 25 | 5
Increased Alkaline Phosphatase | 33 | 3.4 | 26 | 1.2
Albumin decreased | 27 | 1.9 | 18 | 0.9
Hypokalemia | 21 | 7 | 17 | 2.8
Bilirubinemia | 16 | 0.9 | 8 | 0.3
Hypernatremia | 15 | 0 | 14 | 0
Hypomagnesemia | 12 | 4 | 23 | 0
Hematology
Anemia | 84 | 24 | 84 | 25
Leukopenia | 77 | 21 | 81 | 18
Neutropenia | 71 | 37 | 69 | 32
Lymphocytopenia | 67 | 20 | 60 | 19
Thrombocytopenia | 53 | 11 | 54 | 12

Small Cell Lung Cancer

Limited Stage Small Cell Lung Cancer – ADRIATIC

The safety of IMFINZI as a single agent in patients with LS-SCLC without disease progression following completion of concurrent platinum-based chemoradiotherapy (60-66 Gy once daily over 6 weeks or 45 Gy twice daily over 3 weeks) within 42 days prior to initiation of study drug, was evaluated in the ADRIATIC study, a multicenter, randomized, double-blind, placebo-controlled study [see Clinical Studies (14.2)]. A total of 262 patients received IMFINZI 1,500 mg every 4 weeks until disease progression or unacceptable toxicity or a maximum of 24 months. The study excluded patients with Stage I or II LS-SCLC who were considered medically operable and patients with active or prior autoimmune disease or with medical conditions that required systemic corticosteroids or immunosuppressants.

The study population characteristics were: median age of 62 years (range: 28 to 84); 39% age 65 years or older, 6% age 75 years or older; 69% male; 50% white, 48% Asian, 1.3% other races; 4.2% Hispanic or Latino; 68% former smoker, 22% current smoker; and 51% had WHO performance status of 1. Sixty-seven percent of patients received a total radiation dose of 60 Gy to 66 Gy once daily and 27% of patients received a total radiation dose of 45 Gy twice daily. The median duration of exposure to IMFINZI was 9.2 months (range: 0.92 to 25) in the IMFINZI arm.

Serious adverse reactions occurred in 30% of patients receiving IMFINZI. The most frequent serious adverse reactions reported in ≥ 1% of patients receiving IMFINZI were pneumonitis or radiation pneumonitis (12%), and pneumonia (5%). Fatal adverse reactions occurred in 2.7% of patients who received IMFINZI including pneumonia (1.5%), cardiac failure, encephalopathy and pneumonitis (0.4% each). Permanent discontinuation of IMFINZI due to adverse reactions occurred in 16% of the patients. Adverse reactions which resulted in permanent discontinuation of IMFINZI in ≥ 1% of patients included pneumonitis or radiation pneumonitis (9%) and pneumonia (1.5%). Dosage interruptions of IMFINZI due to an adverse reaction occurred in 35% of patients. Adverse reactions which required dosage interruption in ≥ 5% of patients included pneumonitis or radiation pneumonitis (17%). The most common adverse reactions occurring in ≥ 20% of patients receiving IMFINZI were pneumonitis or radiation pneumonitis (38%), and fatigue (21%).

Table 11 summarizes the adverse reactions that occurred in patients treated with IMFINZI in the ADRIATIC study.

Table 11. Adverse Reactions (≥ 10%) in Patients with LS-SCLC Who Received IMFINZI in the ADRIATIC Study
 | IMFINZI; (N=262) |  | Placebo; (N=265)
Adverse Reaction | All Grades (%) | Grade 3 or 4; (%) | All Grades (%) | Grade 3 or 4; (%)
Respiratory, thoracic and mediastinal disorders
Pneumonitis or Radiation pneumonitis [Includes pneumonitis, immune-mediated lung disease, interstitial lung disease, radiation pneumonitis, and lung radiation fibrosis] | 38 | 3.1 | 30 | 2.6
Cough/Productive cough | 17 | 0 | 14 | 0
Dyspnea [Includes dyspnea and exertional dyspnea.] | 11 | 0.4 | 7 | 0
General disorders
Fatigue [Includes fatigue and asthenia.] | 21 | 0.4 | 20 | 2.3
Skin and subcutaneous tissue disorders
Rash [Includes dermatitis, acneiform dermatitis, eczema, rash, maculo-papular rash, papular rash, pruritic rash, and skin exfoliation.] | 18 | 0.4 | 11 | 0
Pruritus | 13 | 0 | 7 | 0
Endocrine disorders
Hypothyroidism [Includes hypothyroidism, increased blood thyroid stimulating hormone, and decreased thyroxine free.] | 17 | 0 | 4.9 | 0
Hyperthyroidism [Includes hyperthyroidism, decreased blood thyroid stimulating hormone, increased thyroxine free, increased thyroxine, increased tri-iodothyronine free, and increased tri-iodothyronine.] | 12 | 0 | 1.9 | 0
Metabolism and nutrition disorders
Decreased appetite | 17 | 0 | 13 | 0
Nervous system disorders
Dizziness [Includes dizziness, postural dizziness, vertigo, and positional vertigo.] | 14 | 0 | 9 | 0
Infections and infestations
Pneumonia [Includes pneumonia, atypical pneumonia, lower respiratory tract infection, bacterial pneumonia, pneumocystis jirovecii pneumonia, legionella pneumonia, and viral pneumonia.] | 13 | 3.1 | 9 | 4.2
Gastrointestinal disorders
Nausea | 13 | 0 | 11 | 0
Diarrhea | 11 | 1.9 | 8 | 0
Constipation | 10 | 0 | 10 | 0

Table 12 summarizes the laboratory abnormalities that occurred in at least 20% of patients treated with IMFINZI.

Table 12. Select Laboratory Abnormalities (≥ 20%) That Worsened from Baseline in Patients with LS-SCLC Who Received IMFINZI in the ADRIATIC Study
Laboratory Abnormality [Graded according to NCI CTCAE version 4.03, except creatinine increased which is graded according to NCI CTCAE version 5.0.] | IMFINZI [The denominator used to calculate the rate varied from 63 to 259 based on the number of patients with a baseline value and at least one post-treatment value.] |  | Placebo [The denominator used to calculate the rate varied from 65 to 262 based on the number of patients with a baseline value and at least one post-treatment value.]
Laboratory Abnormality [Graded according to NCI CTCAE version 4.03, except creatinine increased which is graded according to NCI CTCAE version 5.0.] | All Grades (%) | Grade 3 or 4 (%) | All Grades; (%) | Grade 3 or 4; (%)
Chemistry
Hypocalcemia | 43 | 0 | 43 | 0.8
Hyperglycemia | 38 | 3.2 | 45 | 1.5
ALT increased | 36 | 2.3 | 29 | 2.3
AST increased | 33 | 2.3 | 28 | 1.5
Gamma Glutamyl Transferase increased | 32 | 7 | 27 | 2.9
Hyponatremia | 32 | 5 | 29 | 6.2
Hyperkalemia | 23 | 1.2 | 17 | 0.8
Creatinine increased | 21 | 0 | 17 | 0.8
Hematology
Lymphocytes decreased | 34 | 10 | 33 | 10
Leukocytes decreased | 26 | 0.4 | 33 | 1.1

Extensive Stage Small Cell Lung Cancer – CASPIAN

The safety of IMFINZI in combination with etoposide and either carboplatin or cisplatin in previously untreated ES-SCLC was evaluated in CASPIAN, a randomized, open-label, multicenter, active-controlled study. A total of 265 patients received IMFINZI 1,500 mg in combination with chemotherapy every 3 weeks for 4 cycles followed by IMFINZI 1,500 mg every 4 weeks until disease progression or unacceptable toxicity. The study excluded patients with active or prior autoimmune disease or with medical conditions that required systemic corticosteroids or immunosuppressants [see Clinical Studies (14.2)]. Among 265 patients receiving IMFINZI, 49% were exposed for 6 months or longer and 19% were exposed for 12 months or longer.

Among 266 patients receiving chemotherapy alone, 57% of the patients received 6 cycles of chemotherapy and 8% of the patients received prophylactic cranial irradiation (PCI) after chemotherapy.

IMFINZI was discontinued due to adverse reactions in 7% of the patients receiving IMFINZI plus chemotherapy. These include pneumonitis, hepatotoxicity, neurotoxicity, sepsis, diabetic ketoacidosis and pancytopenia (1 patient each). Serious adverse reactions occurred in 31% of patients receiving IMFINZI plus chemotherapy. The most frequent serious adverse reactions reported in at least 1% of patients were febrile neutropenia (4.5%), pneumonia (2.3%), anemia (1.9%), pancytopenia (1.5%), pneumonitis (1.1%) and COPD (1.1%). Fatal adverse reactions occurred in 4.9% of patients receiving IMFINZI plus chemotherapy. These include pancytopenia, sepsis, septic shock, pulmonary artery thrombosis, pulmonary embolism, and hepatitis (1 patient each) and sudden death (2 patients). The most common adverse reactions (occurring in ≥ 20% of patients) were nausea, fatigue/asthenia and alopecia.

Table 13 summarizes the adverse reactions that occurred in patients treated with IMFINZI plus chemotherapy.

Table 13. Adverse Reactions Occurring in ≥ 10% of Patients in the CASPIAN Study
 | IMFINZI with etoposide and either carboplatin or cisplatin; N = 265 |  | Etoposide and either carboplatin or cisplatin; N = 266
Adverse Reaction | All Grades (%) | Grade 3-4 (%) | All Grades (%) | Grade 3-4 (%)
Gastrointestinal disorders
Nausea | 34 | 0.4 | 34 | 1.9
Constipation | 17 | 0.8 | 19 | 0
Vomiting | 15 | 0 | 17 | 1.1
Diarrhea | 10 | 1.1 | 11 | 1.1
General disorders and administration site conditions
Fatigue/Asthenia | 32 | 3.4 | 32 | 2.3
Skin and subcutaneous tissue disorders
Alopecia | 31 | 1.1 | 34 | 0.8
Rash [Includes rash erythematous, rash generalized, rash macular, rash maculopapular, rash papular, rash pruritic, rash pustular, erythema, eczema, rash and dermatitis.] | 11 | 0 | 6 | 0
Metabolism and nutrition disorders
Decreased appetite | 18 | 0.8 | 17 | 0.8
Respiratory, thoracic and mediastinal disorders
Cough/Productive Cough | 15 | 0.8 | 9 | 0
Endocrine disorders
Hyperthyroidism [Includes hyperthyroidism and Basedow's disease.] | 10 | 0 | 0.4 | 0

Table 14 summarizes the laboratory abnormalities that occurred in at least 20% of patients treated with IMFINZI plus chemotherapy.

Table 14. Laboratory Abnormalities Worsening from Baseline Occurring in ≥ 20% [The frequency cut off is based on any grade change from baseline.] of Patients in the CASPIAN Study
 | IMFINZI with Etoposide and either Carboplatin or Cisplatin | Etoposide and either Carboplatin or Cisplatin
Laboratory Abnormality | Grade [Graded according to NCI CTCAE version 4.03.] 3 or 4 (%) [Each test incidence is based on the number of patients who had both baseline and at least one on-study laboratory measurement available: IMFINZI (range: 258 to 263) and chemotherapy (range: 253 to 262) except magnesium IMFINZI with chemotherapy (18) and chemotherapy (16).] | Grade 3 or 4 (%)
Chemistry
Hyponatremia | 11 | 13
Hypomagnesemia | 11 | 6
Hyperglycemia | 5 | 5
Increased Alkaline Phosphatase | 4.9 | 3.5
Increased ALT | 4.9 | 2.7
Increased AST | 4.6 | 1.2
Hypocalcemia | 3.5 | 2.4
Blood creatinine increased | 3.4 | 1.1
Hyperkalemia | 1.5 | 3.1
TSH decreased < LLN [LLN = lower limit of normal.] and ≥ LLN at baseline | NA | NA
Hematology
Neutropenia | 41 | 48
Lymphopenia | 14 | 13
Anemia | 13 | 22
Thrombocytopenia | 12 | 15

Biliary Tract Cancer

Locally Advanced or Metastatic BTC - TOPAZ-1

The safety of IMFINZI in combination with gemcitabine and cisplatin in locally advanced or metastatic BTC was evaluated in TOPAZ-1, a randomized, double-blind, placebo-controlled, multicenter study. A total of 338 patients received IMFINZI 1,500 mg in combination with gemcitabine and cisplatin every 3 weeks up to 8 cycles followed by IMFINZI 1,500 mg every 4 weeks until disease progression or unacceptable toxicity. Patients with active or prior documented autoimmune or inflammatory disorders, HIV infection or other active infections, including tuberculosis or hepatitis C were ineligible [see Clinical Studies (14.3)].

IMFINZI was discontinued due to adverse reactions in 6% of the patients receiving IMFINZI plus chemotherapy. The most frequently reported events resulting in discontinuation were sepsis (3 patients) and ischemic stroke (2 patients). The remaining events were dispersed across system organ classes and reported in 1 patient each. Serious adverse reactions occurred in 47% of patients receiving IMFINZI plus chemotherapy. The most frequent serious adverse reactions reported in at least 2% of patients were cholangitis (7%), pyrexia (3.8%), anemia (3.6%), sepsis (3.3%) and acute kidney injury (2.4%). Fatal adverse reactions occurred in 3.6% of patients receiving IMFINZI plus chemotherapy. These include ischemic or hemorrhagic stroke (4 patients), sepsis (2 patients) and upper gastrointestinal hemorrhage (2 patients). The most common adverse reactions (occurring in ≥ 20% of patients) were fatigue, nausea, constipation, decreased appetite, abdominal pain, rash and pyrexia. Table 15 summarizes the adverse reactions that occurred in patients treated with IMFINZI plus chemotherapy.

Table 15. Adverse Reactions Occurring in ≥ 10% of Patients in the TOPAZ-1 Study
 | IMFINZI with Gemcitabine and Cisplatin; N = 338 |  | Placebo with Gemcitabine and Cisplatin; N = 342
Adverse Reaction | All Grades [Graded according to NCI CTCAE version 5.0.] (%) | Grade 3-4 (%) | All Grades (%) | Grade 3-4 (%)
General disorders and administration site conditions
Fatigue [Includes fatigue, malaise, cancer fatigue and asthenia.] | 42 | 6 | 43 | 6
Pyrexia | 20 | 1.5 | 16 | 0.6
Gastrointestinal disorders
Nausea | 40 | 1.5 | 34 | 1.8
Constipation | 32 | 0.6 | 29 | 0.3
Abdominal pain [Includes abdominal pain, abdominal pain lower, abdominal pain upper and flank pain.] | 24 | 0.6 | 23 | 2.9
Vomiting | 18 | 1.5 | 18 | 2.0
Diarrhea | 17 | 1.2 | 15 | 1.8
Metabolism and nutrition disorders
Decreased appetite | 26 | 2.1 | 23 | 0.9
Skin and subcutaneous tissue disorders
Rash [Includes rash macular, rash maculopapular, rash morbilliform, rash papular, rash pruritic, rash pustular, rash erythematous, dermatitis acneiform, dermatitis bullous, drug eruption, eczema, erythema, dermatitis and rash.] | 23 | 0.9 | 14 | 0
Pruritus | 11 | 0 | 8 | 0
Psychiatric disorders
Insomnia | 10 | 0 | 11 | 0

Table 16 summarizes the laboratory abnormalities in patients treated with IMFINZI plus chemotherapy.

Table 16. Laboratory Abnormalities Worsening from Baseline Occurring in ≥ 20% [The frequency cut off is based on any grade change from baseline.] of Patients in the TOPAZ-1 Study
 | IMFINZI with Gemcitabine and Cisplatin | Placebo with Gemcitabine and Cisplatin
Laboratory Abnormality | Grade [Graded according to NCI CTCAE version 5.0. Each test incidence is based on the number of patients who had both baseline and at least one on-study laboratory measurement available: IMFINZI with gemcitabine/cisplatin (range: 312 to 335) and Placebo with gemcitabine/cisplatin (range: 319 to 341).] 3 or 4 (%) | Grade 3 or 4 (%)
Chemistry
Hyponatremia | 18 | 13
Gamma-glutamyltransferase increased | 12 | 13
Increased bilirubin | 10 | 14
Hypokalemia | 8 | 4.4
Increased AST | 8 | 8
Increased ALT | 7 | 6
Blood creatinine increased | 5 | 2.1
Hypomagnesemia | 4.5 | 2.2
Hypoalbuminemia | 3.6 | 2.9
Hyperkalemia | 2.1 | 2.1
Increased Alkaline Phosphatase | 1.8 | 3.8
Hypocalcemia | 1.8 | 2.4
Hematology
Neutropenia | 48 | 49
Anemia | 31 | 28
Leukopenia | 28 | 28
Lymphopenia | 23 | 15
Thrombocytopenia | 18 | 18

Hepatocellular Carcinoma

Unresectable HCC - HIMALAYA

The safety of IMFINZI in combination with tremelimumab-actl was evaluated in a total of 388 patients with uHCC in HIMALAYA, a randomized, open-label, multicenter study [see Clinical Studies (14.1)]. Patients received IMFINZI 1,500 mg administered as a single intravenous infusion in combination with tremelimumab-actl 300 mg on the same day, followed by IMFINZI every 4 weeks or sorafenib 400 mg given orally twice daily.

Serious adverse reactions occurred in 41% of patients who received IMFINZI in combination with tremelimumab-actl. Serious adverse reactions in > 1% of patients included hemorrhage (6%), diarrhea (4%), sepsis (2.1%), pneumonia (2.1%), rash (1.5%), vomiting (1.3%), acute kidney injury (1.3%), and anemia (1.3%). Fatal adverse reactions occurred in 8% of patients who received IMFINZI in combination with tremelimumab-actl, including death (1%), hemorrhage intracranial (0.5%), cardiac arrest (0.5%), pneumonitis (0.5%), hepatic failure (0.5%), and immune-mediated hepatitis (0.5%). The most common adverse reactions (occurring in ≥ 20% of patients) were rash, diarrhea, fatigue, pruritus, musculoskeletal pain, and abdominal pain.

Permanent discontinuation of treatment regimen due to an adverse reaction occurred in 14% of patients; the most common adverse reactions leading to treatment discontinuation (≥ 1%) were hemorrhage (1.8%), diarrhea (1.5%), AST increased (1%), and hepatitis (1%).

Dosage interruptions or delay of the treatment regimen due to an adverse reaction occurred in 35% of patients. Adverse reactions which required dosage interruption or delay in ≥ 1% of patients included ALT increased (3.6%), diarrhea (3.6%), rash (3.6%), amylase increased (3.4%), AST increased (3.1%), lipase increased (2.8%), pneumonia (1.5%), hepatitis (1.5%), pyrexia (1.5%), anemia (1.3%), thrombocytopenia (1%), hyperthyroidism (1%), pneumonitis (1%), and blood creatinine increased (1%).

Table 17 summarizes the adverse reactions that occurred in patients treated with IMFINZI in combination with tremelimumab-actl in the HIMALAYA study.

Table 17. Adverse Reactions Occurring in ≥ 10% of Patients in the HIMALAYA Study
 | IMFINZI and Tremelimumab-actl; (N = 388) |  | Sorafenib; (N = 374)
Adverse Reaction | All Grades (%) | Grade 3-4 (%) | All Grades (%) | Grade 3-4 (%)
Skin and subcutaneous tissue disorders
Rash [Represents a composite of multiple related terms.] | 32 | 2.8 | 57 | 12
Pruritus | 23 | 0 | 6 | 0.3
Gastrointestinal disorders
Diarrhea | 27 | 6 | 45 | 4.3
Abdominal pain | 20 | 1.8 | 24 | 4
Nausea | 12 | 0 | 14 | 0
General disorders and administration site conditions
Fatigue | 26 | 3.9 | 30 | 6
Pyrexia | 13 | 0.3 | 9 | 0.3
Musculoskeletal and Connective Tissue Disorders
Musculoskeletal pain | 22 | 2.6 | 17 | 0.8
Metabolism and nutrition disorders
Decreased appetite | 17 | 1.3 | 18 | 0.8
Endocrine disorders
Hypothyroidism | 14 | 0 | 6 | 0
Psychiatric disorders
Insomnia | 10 | 0.3 | 4.3 | 0

Table 18 summarizes the laboratory abnormalities that occurred in patients treated with IMFINZI in combination with tremelimumab-actl in the HIMALAYA study.

Table 18. Laboratory Abnormalities Worsening from Baseline Occurring in ≥ 20% of Patients in the HIMALAYA Study
 | IMFINZI and Tremelimumab-actl |  | Sorafenib
Laboratory Abnormality | Any grade [Graded according to NCI CTCAE version 4.03.] (%) [Each test incidence is based on the number of patients who had both baseline and at least one on-study laboratory measurement available: IMFINZI with tremelimumab-actl (range: 367-378) and sorafenib (range:344-352).] | Grade 3 or 4 (%) | Any grade (%) | Grade 3 or 4 (%)
Chemistry
Aspartate Aminotransferase increased | 63 | 27 | 55 | 21
Alanine Aminotransferase increased | 56 | 18 | 53 | 12
Sodium decreased | 46 | 15 | 40 | 11
Bilirubin increased | 41 | 8 | 47 | 11
Alkaline Phosphatase increased | 41 | 8 | 44 | 5
Glucose increased | 39 | 14 | 29 | 4
Calcium decreased | 34 | 0 | 43 | 0.3
Albumin decreased | 31 | 0.5 | 37 | 1.7
Potassium increased | 28 | 3.8 | 21 | 2.6
Creatinine increased | 21 | 1.3 | 15 | 0.9
Hematology
Hemoglobin decreased | 52 | 4.8 | 40 | 6
Lymphocytes decreased | 41 | 11 | 39 | 10
Platelets decreased | 29 | 1.6 | 35 | 3.1
Leukocytes decreased | 20 | 0.8 | 30 | 1.1

Endometrial Cancer

Advanced or Recurrent dMMR Endometrial Cancer – DUO-E

The safety of IMFINZI in combination with carboplatin and paclitaxel followed by IMFINZI as a single agent was evaluated in 44 patients with dMMR advanced or recurrent endometrial cancer in DUO-E, a randomized, double-blind, placebo-controlled trial [See Clinical Studies (14.5)]. Patients received IMFINZI 1,120 mg with carboplatin and paclitaxel every 3 weeks for up to six 21-day cycles followed by IMFINZI 1,500 mg every 4 weeks or carboplatin and paclitaxel every 3 weeks for up to six 21-day cycles alone. Treatment was continued until disease progression or unacceptable toxicity. The median duration of exposure to IMFINZI with carboplatin and paclitaxel was 14.8 months (range: 0.7 to 31.7).

Serious adverse reactions occurred in 30% of patients who received IMFINZI with carboplatin and paclitaxel. The most common serious adverse reactions (≥4%) were constipation (4.5%) and rash (4.5%).

Permanent discontinuation of IMFINZI due to adverse reactions occurred in 11% of patients. The adverse reaction which resulted in permanent discontinuation of IMFINZI (≥4%) was rash (4.5%).

Dosage interruptions of IMFINZI due to adverse reactions occurred in 52% of patients. Adverse reactions which required dosage interruptions of IMFINZI (≥ 4%) were anemia (11%), thrombocytopenia (9%), neutropenia (9%), COVID-19 (9%), increased ALT (4.5%), and pneumonitis (4.5%).

The most common adverse reactions (> 20%), including laboratory abnormalities, were peripheral neuropathy, musculoskeletal pain, nausea, alopecia, fatigue, abdominal pain, constipation, rash, decreased magnesium, increased ALT, increased AST, diarrhea, vomiting, cough, decreased potassium, dyspnea, headache, increased alkaline phosphatase, and decreased appetite.

Tables 19 and 20 summarize adverse reactions and laboratory abnormalities in DUO-E, respectively.

Table 19. Adverse Reactions Occurring in ≥ 10% of Patients with dMMR tumors in DUO-E
Adverse Reactions | IMFINZI with Carboplatin and Paclitaxel; (N=44) |  | Carboplatin and Paclitaxel; (N=46)
Adverse Reactions | All Grades; (%) | Grade 3-4; (%) | All Grades; (%) | Grade 3-4; (%)
Nervous system disorders
Peripheral neuropathy [Includes neuropathy peripheral, peripheral sensory neuropathy, hypoasthesia, peripheral motor neuropathy, and parasthesia.] | 61 | 2.3 | 61 | 4.3
Headache | 23 | 0 | 17 | 0
Musculoskeletal and connective tissue disorders
Musculoskeletal pain [Includes arthralgia, pain in extremity, back pain, non-cardiac chest pain, myalgia, musculoskeletal pain, musculoskeletal chest pain, arthritis, bone pain, musculoskeletal stiffness, neck pain, musculoskeletal discomfort, and spinal pain.] | 59 | 2.3 | 52 | 2.2
Gastrointestinal disorders
Nausea | 59 | 0 | 48 | 2.2
Abdominal pain [Includes abdominal pain, abdominal pain lower, flank pain, abdominal discomfort, and abdominal pain upper.] | 39 | 0 | 24 | 2.2
Constipation [Includes constipation and fecaloma.] | 39 | 4.5 | 35 | 2.2
Diarrhea | 27 | 2.3 | 24 | 2.2
Vomiting | 27 | 0 | 22 | 4.3
Skin and subcutaneous tissue disorders
Alopecia | 52 | 0 | 41 | 0
Rash [Includes eczema, rash, rash erythematous, rash maculo-papular, dermatitis, rash pustular, skin exfoliation, and symmetrical drug-related intertriginous, and flexural exanthema.] | 39 | 2.3 | 17 | 2.2
Pruritus | 16 | 0 | 11 | 0
General disorders and administration site conditions
Fatigue [Includes asthenia and fatigue.] | 41 | 4.5 | 57 | 11
Peripheral edema [Includes peripheral edema, peripheral swelling, and edema.] | 16 | 0 | 13 | 2.2
Respiratory, thoracic and mediastinal disorders
Cough / productive cough | 27 | 0 | 20 | 0
Dyspnea [Includes dyspnea and exertional dyspnea.] | 25 | 2.3 | 9 | 0
Metabolism and nutrition disorders
Decreased appetite | 18 | 0 | 18 | 0
Infections and infestations
Upper respiratory tract infection [Includes nasopharyngitis, pharyngitis, rhinitis, sinusitis, tracheobronchitis, and upper respiratory tract infection.] | 14 | 0 | 4.3 | 0
Endocrine disorders
Hypothyroidism [Includes blood thyroid stimulating hormone increased, and hypothyroidism.] | 11 | 0 | 4.3 | 0

Clinically relevant adverse reactions in < 10% of patients who received IMFINZI with carboplatin and paclitaxel included autoimmune hemolytic anemia, colitis, immune-mediated thyroiditis, infusion related reaction, interstitial lung disease, myositis, pneumonitis, pulmonary embolism, and sepsis.

Table 20 summarizes the laboratory abnormalities that occurred in patients treated with IMFINZI with carboplatin and paclitaxel followed by IMFINZI as a single agent.

Table 20. Select Laboratory Abnormalities Worsening from Baseline Occurring in ≥ 20% of Patients with dMMR tumors in DUO-E
Laboratory Abnormality | IMFINZI with Carboplatin and Paclitaxel [Each test incidence is based on the number of patients who had both baseline and at least one on-study laboratory measurement available: IMFINZI with carboplatin and paclitaxel (range: 40 to 44), and carboplatin and paclitaxel (range: 37 to 46)] |  | Carboplatin and Paclitaxel
Laboratory Abnormality | All Grades; (%) | Grade 3-4; (%) | All Grades; (%) |  | Grade 3-4; (%)
Chemistry
Magnesium decreased | 36 | 0 | 30 | 2.5
ALT increased | 32 | 2.3 | 22 | 2.2
AST increased | 30 | 2.3 | 22 | 0
Potassium decreased | 25 | 0 | 24 | 2.2
Alkaline phosphatase increased | 20 | 0 | 16 | 0

Muscle Invasive Bladder Cancer (MIBC)

Neoadjuvant and adjuvant treatment of MIBC – NIAGARA

The safety of IMFINZI in combination with neoadjuvant gemcitabine and cisplatin followed by surgery and continued IMFINZI treatment as adjuvant, single-agent therapy was evaluated in NIAGARA, a randomized, open-label, multicenter trial. Patients received IMFINZI in combination with chemotherapy (n=530) or received chemotherapy alone (n=526) [see Clinical Studies (14.6)].

The median duration of exposure to IMFINZI 1,500 mg every 3 weeks in the neoadjuvant phase was 12 weeks (range: 1.1 to 84 weeks). The median duration of exposure to IMFINZI 1,500 mg every 4 weeks in the adjuvant phase was 32 weeks (range: 2.4 to 50 weeks).

The most common adverse reactions, including laboratory abnormalities, in the overall study (occurring in ≥ 20% of patients) were decreased hemoglobin, decreased neutrophils, increased blood creatinine, decreased sodium, nausea, increased ALT, decreased calcium, decreased platelets, fatigue, increased potassium, decreased lymphocytes, increased AST, constipation, decreased magnesium, decreased appetite, increased alkaline phosphate, rash, pyrexia, diarrhea, vomiting, and abdominal pain.

Table 21 summarizes the adverse reactions that occurred in patients treated with IMFINZI plus chemotherapy.

Table 21. Adverse Reactions Occurring in ≥ 10% of Patients in the NIAGARA Study
 | IMFINZI with gemcitabine and; cisplatin; N = 530 |  | Gemcitabine and cisplatin; N = 526
Adverse Reaction | All Grades [Graded according to NCI CTCAE version 5.0.] (%) | Grade 3-4 (%) | All Grades (%) | Grade 3-4 (%)
Gastrointestinal disorders
Nausea | 54 | 1.5 | 48 | 1
Constipation | 39 | 0.8 | 39 | 0.8
Diarrhea | 21 | 1.5 | 14 | 0.4
Vomiting [Includes multiple similar terms.] | 20 | 0.9 | 19 | 0.2
Abdominal pain | 20 | 0.9 | 13 | 1
General disorders and administration site conditions
Fatigue | 52 | 2.3 | 49 | 3
Pyrexia | 22 | 0.4 | 17 | 0
Edema | 13 | 0.4 | 13 | 0
Metabolism and nutrition disorders
Decreased appetite | 27 | 0.6 | 25 | 0.6
Skin and subcutaneous tissue disorders
Rash | 23 | 1.3 | 12 | 0.6
Pruritus | 15 | 0 | 7 | 0
Nervous system disorders
Peripheral neuropathy | 16 | 0.2 | 14 | 0
Headache | 11 | 0 | 11 | 0
Dizziness | 11 | 0 | 10 | 0.2
Endocrine disorders
Hypothyroidism | 13 | 0.4 | 2.3 | 0
Vascular disorders
Hypertension | 12 | 4.5 | 9 | 2.9
Hemorrhage | 11 | 0.9 | 10 | 2.1

Table 22 summarizes the laboratory abnormalities in patients treated with IMFINZI plus chemotherapy.

Table 22. Select Laboratory Abnormalities That Worsened from Baseline in ≥ 20% of Patients Who Received IMFINZI with Chemotherapy in the NIAGARA study
Laboratory Abnormality | IMFINZI with gemcitabine and cisplatin [Each test incidence is based on the number of patients who had both baseline and at least one on-study laboratory measurement available: IMFINZI plus chemotherapy (range: 482 to 528), and chemotherapy (range: 467 to 521).] |  | Gemcitabine and cisplatin
Laboratory Abnormality | All Grades [Graded per NCI CTCAE V5.]; (%) | Grade; 3 or 4; (%) | All; Grades; (%) | Grade; 3 or 4; (%)
Chemistry
Increased blood creatinine | 63 | 9 | 58 | 7
Decreased sodium | 54 | 9 | 55 | 10
Increased ALT | 53 | 2.3 | 54 | 4.0
Decreased calcium | 52 | 1.3 | 43 | 1.2
Increased potassium | 51 | 4.2 | 49 | 4.4
Increased AST | 42 | 1.5 | 39 | 2.1
Decreased magnesium | 38 | 1.9 | 37 | 2.3
Increased alkaline phosphate | 26 | 0.8 | 25 | 0.4
Hematology
Decreased hemoglobin | 88 | 13 | 87 | 13
Decreased neutrophils | 76 | 31 | 74 | 34
Decreased platelets | 52 | 6 | 50 | 7
Decreased lymphocytes | 44 | 10 | 40 | 8

Neoadjuvant Phase of NIAGARA

A total of 530 patients received at least 1 dose of IMFINZI in combination with chemotherapy as neoadjuvant treatment in the IMFINZI treatment arm, and 526 patients received at least 1 dose of chemotherapy as neoadjuvant treatment in the chemotherapy treatment arm. In the neoadjuvant phase, serious adverse reactions occurred in 24% of patients who received IMFINZI in combination with chemotherapy; the most frequent (≥1%) serious adverse reactions were pulmonary embolism (1.9%), febrile neutropenia (1.5%), acute kidney injury (1.3%), thrombocytopenia (1.3%), urinary tract infection (1.3%) and pneumonia (1.3%). Fatal adverse reactions occurred in 1.1% of patients including sepsis (0.2%), myocardial infarction (0.2%), and pulmonary embolism (0.2%). One fatal adverse reaction of pneumonia was reported in 1 (0.2%) patient in the post-surgery phase before adjuvant treatment started.

Permanent discontinuation of IMFINZI due to an adverse reaction in the neoadjuvant phase occurred in 9% of patients while receiving IMFINZI in combination with chemotherapy. The most frequent (≥ 0.5%) adverse reactions that led to permanent discontinuation of IMFINZI were blood creatinine increased (0.9%), neutropenia (0.6%), acute kidney injury (0.6%), asthenia (0.6%) and fatigue (0.6%).

Of the 530 patients in the IMFINZI treatment arm and 526 patients in the chemotherapy treatment arm who received neoadjuvant treatment, 1 (0.2%) patient in each treatment arm did not receive surgery due to adverse reactions. The adverse reaction that led to cancellation of surgery in the IMFINZI treatment arm was interstitial lung disease.

Of the 469 patients in the IMFINZI treatment arm who underwent radical cystectomy, 4 (0.8%) patients experienced delay of surgery (defined as occurring more than 56 days after the last dose of neoadjuvant treatment) due to adverse reactions.

Adjuvant Phase of NIAGARA

A total of 383 patients (72%) in the IMFINZI treatment arm received at least 1 dose of adjuvant treatment.

Serious adverse reactions occurred in 26% of patients receiving IMFINZI as adjuvant treatment. The most frequent serious adverse reactions (occurring in ≥1% of patients) were urinary tract infection (7%), acute kidney injury (3.7%), hydronephrosis (2.1%), pyelonephritis (2.1%), urosepsis (1.8%), and sepsis (1.6%). Fatal adverse reactions occurred in 1.8% of patients, including COVID-19 (0.3%), severe acute respiratory syndrome (0.3%), cardiopulmonary failure (0.3%), gastrointestinal haemorrhage (0.3%), and chronic hepatic failure (0.3%).

Permanent discontinuation of adjuvant IMFINZI due to an adverse reaction occurred in 5% of patients. The most frequent (≥0.5%) adverse reactions that led to permanent discontinuation of adjuvant IMFINZI were nephritis (0.8%), fatigue (0.5%), diarrhea (0.5%), decreased appetite (0.5%) and pneumonitis (0.5%).

Gastric or Gastroesophageal Junction Adenocarcinoma (GC/GEJC)

Neoadjuvant and Adjuvant Treatment of Resectable GC/GEJC – MATTERHORN

The safety of IMFINZI with FLOT as neoadjuvant and adjuvant treatment, followed by single-agent IMFINZI, was evaluated in MATTERHORN, a randomized, double-blind, placebo-controlled, multicenter study of patients with resectable GC/GEJC (Stage II to Stage IVA [AJCC, 8th edition]) [see Clinical Studies (14.7)].

Safety data are available for the 944 patients who received IMFINZI with FLOT (n=475) or placebo with FLOT (n=469).

The median duration of exposure to IMFINZI 1,500 mg every 4 weeks in the neoadjuvant phase was 8 weeks (range: 1.4 to 8.7 weeks). The median duration of exposure to IMFINZI 1,500 mg every 4 weeks in the adjuvant phase was 48 weeks (range: 1.9 to 50.1 weeks).

The most common adverse reactions (occurring in ≥ 20% of patients) were diarrhea, nausea, peripheral neuropathy, fatigue, alopecia, decreased appetite, rash, abdominal pain, vomiting, musculoskeletal pain, pyrexia, and stomatitis.

Table 23 summarizes the adverse reactions that occurred in ≥ 10% of patients treated with IMFINZI in combination with FLOT chemotherapy.

Table 23: Adverse Reactions Occurring in ≥ 10% of Patients in the MATTERHORN study
Adverse Reaction | IMFINZI with FLOT Chemotherapy; N=475 |  | Placebo with FLOT Chemotherapy; N=469
Adverse Reaction | All Grades (%) | Grade 3 or 4 (%) | All Grades (%) | Grade 3 or 4 (%)
Gastrointestinal disorders
Diarrhea [Includes multiple similar terms.] | 64 | 8 | 59 | 7
Nausea | 51 | 2.5 | 51 | 1.5
Vomiting | 26 | 2.1 | 26 | 3
Abdominal pain | 27 | 2.3 | 29 | 1.3
Stomatitis | 20 | 1.1 | 15 | 0.6
Constipation | 16 | 0 | 17 | 0.9
Dysphagia | 10 | 1.5 | 8 | 1.5
Nervous system disorders
Peripheral neuropathy | 51 | 3.6 | 47 | 2.3
Dysgeusia | 19 | 0 | 15 | 0
General disorders and administration site conditions
Fatigue | 47 | 5 | 45 | 5
Pyrexia | 20 | 0.8 | 16 | 1.3
Skin and subcutaneous tissue disorders
Alopecia | 31 | 0 | 32 | 0
Rash | 30 | 1.5 | 20 | 0.4
Pruritus | 11 | 0 | 5 | 0
Metabolism and nutrition disorders
Decreased appetite | 31 | 3.2 | 30 | 2.1
Musculoskeletal and connective tissue disorders
Musculoskeletal pain | 21 | 1.5 | 19 | 0.6
Infections and infestations
COVID-19 | 19 | 1.7 | 16 | 0.6
Pneumonia | 11 | 3.8 | 10 | 4.3
Investigations
Weight decreased | 15 | 2.1 | 19 | 3.4
Vascular disorders
Hemorrhage | 14 | 2.5 | 15 | 2.8
Respiratory, thoracic and mediastinal disorders
Cough | 10 | 0 | 10 | 0

Table 24 summarizes the laboratory abnormalities in patients treated with IMFINZI in combination with FLOT chemotherapy.

Table 24: Laboratory Abnormalities (> 20%) That Worsened from Baseline in Patients with Disease Who Received IMFINZI with FLOT Chemotherapy in MATTERHORN
Laboratory Abnormality [Graded per NCI CTCAE v5.0] | IMFINZI with FLOT Chemotherapy [The denominator used to calculate the rate varied from 444 to 472 based on the number of patients with a baseline value and at least one post-treatment value.] |  | Placebo with FLOT Chemotherapy [The denominator used to calculate the rate varied from 443 to 468 based on the number of patients with a baseline value and at least one post-treatment value.]
Laboratory Abnormality [Graded per NCI CTCAE v5.0] | All Grades; (%) | Grade; 3 or 4; (%) | All; Grades; (%) | Grade; 3 or 4; (%)
Hematology
Decreased leukocytes | 75 | 14 | 79 | 17
Decreased neutrophils | 70 | 41 | 74 | 44
Decreased hemoglobin | 68 | 7 | 73 | 8
Decreased lymphocytes | 49 | 13 | 45 | 13
Decreased platelets | 47 | 1.1 | 46 | 1.9
Chemistry
Increased AST | 72 | 6 | 69 | 6
Increased ALT | 70 | 7 | 65 | 6
Increased GGT | 57 | 10 | 51 | 6
Increased lipase | 55 | 16 | 55 | 15
Increased alkaline phosphatase | 53 | 3.2 | 51 | 1.5
Decreased calcium | 45 | 0.8 | 47 | 2.6
Increased amylase | 42 | 6 | 39 | 4.5
Decreased potassium | 39 | 8 | 40 | 8
Decreased sodium | 33 | 4.4 | 32 | 4.7
Decreased albumin | 31 | 1.5 | 31 | 0.2
Increased potassium | 22 | 0.6 | 26 | 1.3

Adverse Reactions by Phase of Treatment

Table 25 summarizes safety profile by Phase of treatment.

Table 25: Safety Profile by Phase of Treatment
 | IMFINZI with FLOT Chemotherapy | Placebo with FLOT Chemotherapy
Neoadjuvant Phase
Number of Patients | 475 | 469
Serious Adverse Reactions | 21% | 18%
Deaths during Treatment-emergent period | 1.9% | 1.7%
Permanent discontinuation of IMFINZI or Placebo | 2.5% | 2.1%
No surgery due to Adverse Reaction | 0.6% | 0.4%
Delay in surgery due to Adverse Reaction | 2.3% | 2.6%
Adjuvant Phase
Number of Patients | 365 | 351
Serious Adverse Reactions | 29% | 26%
Deaths during Treatment-emergent period | 2.2% | 2.6%
Permanent discontinuation of IMFINZI or Placebo | 7% | 4.6%
Adjuvant Phase (IMFINZI as a single-agent)
Number of Patients | 345 | 331
Serious Adverse Reactions | 14% | 15%
Deaths during Treatment-emergent period | 1.7% | 2.4%
Permanent discontinuation of IMFINZI or Placebo | 6% | 2.7%

Serious adverse reactions (≥2%) in the IMFINZI arm were diarrhea (2.5%) during the neoadjuvant phase, and pneumonia (2.5%) in the adjuvant phase.

Deaths (≥2 patients) in the IMFINZI arm were septic shock (0.6%) and acute coronary syndrome (0.4%) during the neoadjuvant phase; gastrointestinal perforation (0.5%) and COVID-19 (0.5%) during adjuvant phase; and gastrointestinal perforation (0.6%) and COVID-19 (0.6%) in the single-agent adjuvant phase.

Permanent discontinuation of IMFINZI (≥2 patients) due an adverse reaction in the IMFINZI arm were nephritis (0.4%) during the neoadjuvant phase; hepatitis (1.1%), pneumonitis (1.1%), rash (0.8%), musculoskeletal pain (0.5%), and renal failure (0.5%) during adjuvant phase; and hepatitis (0.9%), pneumonitis (0.9%), musculoskeletal pain (0.6%), and renal failure (0.6%) during the single-agent adjuvant phase.

8 USE IN SPECIFIC POPULATIONS

8.1 Pregnancy

Risk Summary

Based on findings from animal studies and its mechanism of action, IMFINZI can cause fetal harm when administered to a pregnant woman [see Clinical Pharmacology (12.1)]. There are no available data on the use of IMFINZI in pregnant women.

In animal reproduction studies, administration of durvalumab to pregnant cynomolgus monkeys from the confirmation of pregnancy through delivery at exposure levels approximately 6 to 20 times higher than those observed at the clinical dose of 10 mg/kg based on area under the curve (AUC), resulted in an increase in premature delivery, fetal loss, and premature neonatal death (see Data). Human immunoglobulin G1 (IgG1) is known to cross the placental barrier; therefore, durvalumab has the potential to be transmitted from the mother to the developing fetus. Apprise pregnant women of the potential risk to a fetus.

In the U.S. general population, the estimated background risk of major birth defects and miscarriage in clinically recognized pregnancies is 2 to 4% and 15 to 20%, respectively.

Data

Animal Data

As reported in the literature, the PD-1/PD-L1 pathway plays a central role in preserving pregnancy by maintaining maternal immune tolerance to the fetus. In mouse allogeneic pregnancy models, disruption of PD-L1 signaling was shown to result in an increase in fetal loss. The effects of durvalumab on prenatal and postnatal development were evaluated in reproduction studies in cynomolgus monkeys. Durvalumab was administered from the confirmation of pregnancy through delivery at exposure levels approximately 6 to 20 times higher than those observed at a clinical dose of 10 mg/kg (based on AUC). Administration of durvalumab resulted in premature delivery, fetal loss (abortion and stillbirth), and increase in neonatal deaths. Durvalumab was detected in infant serum on postpartum Day 1, indicating the presence of placental transfer of durvalumab. Based on its mechanism of action, fetal exposure to durvalumab may increase the risk of developing immune-mediated disorders or altering the normal immune response and immune-mediated disorders have been reported in PD-1 knockout mice.

8.2 Lactation

Risk Summary

There are no data on the presence of durvalumab in human milk, its effects on the breastfed child, or the effects on milk production. Maternal IgG is known to be present in human milk. The effects of local gastrointestinal exposure and limited systemic exposure in the breastfed child to IMFINZI are unknown. Durvalumab was present in the milk of lactating cynomolgus monkeys and was associated with premature neonatal death (see Data).

Because of the potential for adverse reactions in a breastfed child, advise women not to breastfeed during treatment with IMFINZI and for 3 months after the last dose. Refer to the Prescribing Information for the agents administered in combination with IMFINZI for recommended duration to not breastfeed, as appropriate.

Data

In lactating cynomolgus monkeys, durvalumab was present in breast milk at about 0.15% of maternal serum concentrations after administration of durvalumab from the confirmation of pregnancy through delivery at exposure levels approximately 6 to 20 times higher than those observed at the recommended clinical dose of 10 mg/kg (based on AUC). Administration of durvalumab resulted in premature neonatal death.

8.3 Females and Males of Reproductive Potential

Pregnancy testing

Verify pregnancy status of females of reproductive potential prior to initiating treatment with IMFINZI.

Contraception

Females

IMFINZI can cause fetal harm when administered to a pregnant woman [see Use in Specific Populations (8.1)]. Advise females of reproductive potential to use effective contraception during treatment with IMFINZI and for 3 months following the last dose of IMFINZI. Refer to the Prescribing Information for the agents administered in combination with IMFINZI for recommended contraception duration, as appropriate.

8.4 Pediatric Use

The safety and effectiveness of IMFINZI have not been established in pediatric patients. Safety and efficacy were assessed but not established in a multi-center, open-label study (NCT03837899) in 45 pediatric patients aged 1 to < 17 years with advanced solid tumors. All 45 patients received at least a single dose of IMFINZI, and 41 patients received IMFINZI in combination with tremelimumab-actl. No new safety signals were observed in pediatric patients in this study.

Durvalumab systemic exposure in pediatric patients weighing ≥ 35 kg was within the range of values previously observed in adults given the same weight-based dose, whereas the systemic exposure in pediatric patients weighing < 35 kg was lower than that observed in adults.

8.5 Geriatric Use

Of the 401 patients with resectable NSCLC treated with IMFINZI in combination with chemotherapy in the AEGEAN study, 209 (52%) patients were 65 years or older and 49 (12%) patients were 75 years or older. There were no overall clinically meaningful differences in safety or efficacy between patients ≥ 65 years of age and younger patients.

Of the 476 patients with unresectable, Stage III NSCLC treated with IMFINZI in the PACIFIC study, 45% were 65 years or older, while 7.6% were 75 years or older. No overall differences in safety or effectiveness were observed between patients 65 years or older and younger patients. The PACIFIC study did not include sufficient numbers of patients aged 75 years and over to determine whether they respond differently from younger patients.

Of the 330 patients with metastatic NSCLC treated with IMFINZI in combination with tremelimumab-actl and platinum-based chemotherapy, 143 (43%) patients were 65 years or older and 35 (11%) patients were 75 years or older. There were no clinically meaningful differences in safety or efficacy between patients 65 years or older and younger patients.

Of the 262 patients with LS-SCLC treated with IMFINZI, 103 (39%) patients were 65 years or older and 15 (6%) patients were 75 years or older. There were no clinically meaningful differences in safety and efficacy between patients 65 years or older and younger patients.

Of the 265 patients with ES-SCLC treated with IMFINZI in combination with chemotherapy 101 (38%) patients were 65 years or older and 19 (7.2%) patients were 75 years or older. There were no clinically meaningful differences in safety or efficacy between patients 65 years or older and younger patients.

Of the 338 patients with BTC treated with IMFINZI in combination with chemotherapy in the TOPAZ-1 study, 158 (47%) patients were 65 years or older and 38 (11%) patients were 75 years or older. No overall differences in safety or effectiveness of IMFINZI have been observed between patients 65 years of age and older and younger adult patients.

Of the 393 patients with uHCC treated with IMFINZI in combination with tremelimumab-actl, 50% of patients were 65 years of age or older and 13% of patients were 75 years of age or older. No overall differences in safety or effectiveness of IMFINZI have been observed between patients 65 years of age and older and younger adult patients.

Of the 235 patients with endometrial cancer treated with IMFINZI with carboplatin and paclitaxel, 49% of patients were 65 years of age or older and 12% of patients were 75 years of age or older. No overall differences in safety or effectiveness of IMFINZI have been observed between patients 65 years of age and older and younger adult patients.

Of the 530 patients with MIBC treated with IMFINZI in combination with gemcitabine and cisplatin in the NIAGARA study, 272 (51%) patients were 65 years or older, and 57 (11%) patients were 75 years or older. No overall differences in safety or effectiveness of IMFINZI have been observed between patients 65 years of age and older and younger adult patients.

Of the 475 patients with resectable GC/GEJC treated with IMFINZI in combination with FLOT chemotherapy in the MATTERHORN study, 184 (39%) patients were 65 years or older and 37 (8%) patients were 75 years or older. No overall differences in safety or effectiveness were observed between patients ≥ 65 years of age and younger adult patients.

11 DESCRIPTION

Durvalumab is a programmed cell death ligand 1 (PD-L1) blocking antibody. Durvalumab is a human immunoglobulin G1 kappa (IgG1κ) monoclonal antibody that is produced by recombinant DNA technology in Chinese Hamster Ovary (CHO) cell suspension culture.

IMFINZI (durvalumab) Injection for intravenous use is a sterile, preservative-free, clear to opalescent, colorless to slightly yellow solution, free from visible particles.

Each 500 mg vial of IMFINZI contains 500 mg of durvalumab in 10 mL solution. Each mL contains durvalumab, 50 mg, L-histidine (2 mg), L-histidine hydrochloride monohydrate (2.7 mg), α,α-trehalose dihydrate (104 mg), Polysorbate 80 (0.2 mg), and Water for Injection, USP.

Each 120 mg vial of IMFINZI contains 120 mg of durvalumab in 2.4 mL solution. Each mL contains durvalumab, 50 mg, L-histidine (2 mg), L-histidine hydrochloride monohydrate (2.7 mg), α,α-trehalose dihydrate (104 mg), Polysorbate 80 (0.2 mg), and Water for Injection, USP.

12 CLINICAL PHARMACOLOGY

12.1 Mechanism of Action

Expression of programmed cell death ligand-1 (PD-L1) can be induced by inflammatory signals (e.g., IFN-gamma) and can be expressed on both tumor cells and tumor-associated immune cells in the tumor microenvironment. PD-L1 blocks T-cell function and activation through interaction with PD-1 and CD80 (B7.1). By binding to its receptors, PD-L1 reduces cytotoxic T-cell activity, proliferation, and cytokine production.

Durvalumab is a human immunoglobulin G1 kappa (IgG1κ) monoclonal antibody that binds to PD-L1 and blocks the interaction of PD-L1 with PD-1 and CD80 (B7.1). Blockade of PD-L1/PD-1 and PD-L1/CD80 interactions releases the inhibition of immune responses, without inducing antibody dependent cell-mediated cytotoxicity (ADCC).

PD-L1 blockade with durvalumab led to increased T-cell activation in vitro and decreased tumor size in co-engrafted human tumor and immune cell xenograft mouse models.

12.2 Pharmacodynamics

The steady state AUC, Ctrough, and Cmax in patients administered with 1,500 mg every 4 weeks are 6% higher, 19% lower, and 55% higher than those administered with 10 mg/kg every 2 weeks, respectively. Based on the modeling of pharmacokinetic data and exposure relationships for safety, there are no anticipated clinically meaningful differences in efficacy and safety for the doses of 1,500 mg every 4 weeks compared to 10 mg/kg every 2 weeks in patients weighing > 30 kg with NSCLC.

12.3 Pharmacokinetics

The pharmacokinetics of durvalumab as a single agent was studied in patients with doses ranging from 0.1 mg/kg (0.01 times the approved recommended dosage) to 20 mg/kg (2 times the approved recommended dosage) administered once every two, three, or four weeks.

PK exposure increased more than dose-proportionally at doses < 3 mg/kg (0.3 times the approved recommended dosage) and dose proportionally at doses ≥ 3 mg/kg every 2 weeks. Steady state was achieved at approximately 16 weeks.

The pharmacokinetics of durvalumab is similar when assessed as a single agent, when in combination with chemotherapy, when in combination with tremelimumab-actl and when in combination with tremelimumab-actl and platinum-based chemotherapy.

Distribution

The geometric mean (% coefficient of variation [CV%]) steady state volume of distribution (Vss) was 5.4 (13.1%) L.

Elimination

Durvalumab clearance decreases over time, with a mean maximal reduction (CV%) from baseline values of approximately 23% (57%) resulting in a geometric mean (CV%) steady state clearance (CLss) of 8 mL/h (39%) at day 365; the decrease in CLss is not considered clinically relevant. The geometric mean (CV%) terminal half-life, based on baseline CL was approximately 21 (26%) days.

Specific Populations

There were no clinically significant differences in the pharmacokinetics of durvalumab based on body weight (31 to 175 kg), age (18 to 96 years), sex, race (White, Black, Asian, Native Hawaiian, Pacific Islander, or Native American), albumin levels (4 to 57 g/L), lactate dehydrogenase levels (18 to 15,800 U/L), soluble PD-L1 (67 to 3,470 pg/mL), tumor type (NSCLC, SCLC, BTC and HCC), mild or moderate renal impairment (CLcr 30 to 89 mL/min), and mild or moderate hepatic impairment (bilirubin ≤ 3x ULN and any AST). The effect of severe renal impairment (CLcr 15 to 29 mL/min) or severe hepatic impairment (bilirubin > 3x ULN and any AST) on the pharmacokinetics of durvalumab is unknown.

12.6 Immunogenicity

The observed incidence of anti-drug antibodies (ADA) is highly dependent on the sensitivity and specificity of the assay. Differences in assay methods preclude meaningful comparison of the incidence of ADAs in the studies described below with the incidence of ADAs in other studies including those of IMFINZI or of other durvalumab products.

In clinical trials of patients who received IMFINZI for 10 to 48 weeks at dosages of 1,500 mg every 4 weeks, 10 mg/kg every 2 weeks, 20 mg/kg every 4 weeks as a single agent or 1,120 mg every 3 weeks, or 1,500 mg every 3 weeks in the combination therapies, 3.6% (199/5562) of evaluable patients tested positive for treatment-emergent anti-durvalumab antibodies, and 8.5% (17/199) of treatment-emergent ADA positive patients had neutralizing antibodies against durvalumab. There were no identified clinically significant effects of ADAs on durvalumab pharmacokinetics or safety; however, the effect of these ADAs on the effectiveness of IMFINZI is unknown.

13 NONCLINICAL TOXICOLOGY

13.1 Carcinogenesis, Mutagenesis, Impairment of Fertility

The carcinogenic and genotoxic potential of durvalumab have not been evaluated.

Animal fertility studies have not been conducted with durvalumab. In repeat-dose toxicology studies with durvalumab in sexually mature cynomolgus monkeys of up to 3 months duration, there were no notable effects on the male and female reproductive organs.

13.2 Animal Toxicology and/or Pharmacology

In animal models, inhibition of PD-L1/PD-1 signaling increased the severity of some infections and enhanced inflammatory responses. Mycobacterium tuberculosis-infected PD-1 knockout mice exhibit markedly decreased survival compared with wild-type controls, which correlated with increased bacterial proliferation and inflammatory responses in these animals. PD-1 blockade using a primate anti-PD-1 antibody was also shown to exacerbate M. tuberculosis infection in rhesus macaques. PD-L1 and PD-1 knockout mice and mice receiving PD-L1 blocking antibody have also shown decreased survival following infection with lymphocytic choriomeningitis virus.

14 CLINICAL STUDIES

14.1 Non-Small Cell Lung Cancer (NSCLC)

Neoadjuvant and Adjuvant Treatment of Resectable NSCLC – AEGEAN Study

The efficacy of IMFINZI in combination with neoadjuvant chemotherapy, followed by surgery and continued adjuvant treatment with IMFINZI as a single agent was investigated in AEGEAN (NCT03800134), a randomized, double-blind, placebo-controlled, multicenter trial conducted in 802 patients with previously untreated and resectable squamous or non-squamous NSCLC (Stage IIA to select Stage IIIB [AJCC, 8th edition]). Patients were enrolled regardless of tumor PD-L1 expression. Eligible patients had no prior exposure to immune-mediated therapy, a WHO/ECOG Performance status of 0 or 1, and at least one RECIST 1.1 target lesion.

Patients with active or prior documented autoimmune disease, or use of any immunosuppressive medication within 14 days of the first dose of IMFINZI were ineligible. The population for efficacy analyses was a modified intent-to-treat [mITT] which excluded patients with known EGFR mutations or ALK rearrangements.

Crossover between the study arms was not permitted. Randomization was stratified by disease stage (Stage II vs. Stage III) and by PD-L1 expression (TC < 1% vs. TC ≥ 1%) status. Patients were randomized 1:1 to one of the following treatment arms:

- Arm 1: Neoadjuvant IMFINZI 1,500 mg once every 3 weeks for up to 4 cycles in combination with:

Squamous tumor histology: carboplatin AUC 6 and paclitaxel 200 mg/m^2 on Day1 of each 3-week cycle, OR cisplatin 75 mg/m^2 on Day 1 and gemcitabine 1250 mg/m^2 on Day 1 and Day 8 of each 3-week cycle, for 4 cycles

Non-squamous tumor histology: pemetrexed 500 mg/m^2 and cisplatin 75 mg/m^2 on Day 1 of each 3-week cycle, for 4 cycles OR pemetrexed 500 mg/m^2 and carboplatin AUC 5 on Day 1 of each 3-week cycle, for 4 cycles.

Followed by adjuvant IMFINZI 1,500 mg as a single agent for up to 12 cycles post-surgery.

- Arm 2: Neoadjuvant placebo in combination with 4 cycles of chemotherapy (see above) prior to surgery.
- Followed by placebo for up to 12 cycles post-surgery.

All study medications were administered via intravenous infusion. In the event of unfavorable tolerability, patients who met the eligibility criteria were switched from cisplatin to carboplatin therapy at any point during the study. In patients with comorbidities or unable to tolerate cisplatin as per Investigators judgment, carboplatin AUC 5 could be administered from cycle 1. Treatment with IMFINZI or placebo continued until completion of the treatment, disease progression that precluded definitive surgery, inability to complete definitive surgery, disease recurrence in the adjuvant phase, or unacceptable toxicity. A RECIST 1.1 tumor assessment was performed at baseline, and upon completion of the neoadjuvant period (prior to surgery). Tumor assessments were conducted at 5 weeks postoperatively, prior to the start of adjuvant therapy and every 12 weeks until week 48, every 24 weeks for approximately 4 years, and then every 48 weeks thereafter until disease progression, consent withdrawal, or death.

The trial was not designed to isolate the effect of IMFINZI in each phase (neoadjuvant or adjuvant) of treatment.

The major efficacy outcome measures of the study were pathological complete response (pCR) by blinded central pathology review and event-free survival (EFS) by blinded independent central review (BICR) assessment. Additional efficacy outcome measures were major pathological response (MPR) by blinded central pathology review, DFS by BICR, and OS.

The demographics and baseline disease characteristics were as follows: male (72%); median age 65 years (range: 30 to 88); age ≥ 65 years (52%); WHO/ECOG PS 0 (68%), WHO/ECOG PS 1 (32); White (54%), Asian (41%), Black or African American (0.9%), American Indian or Alaska Native (1.4%), Other Race (2.6%); Not Hispanic or Latino (84%); current or past smokers (86%); squamous histology (49%) and non-squamous histology (51%); Stage II (28%), Stage III (71%); PD-L1 expression status TC ≥ 1% (67%), PD-L1 expression status TC < 1% (33%).

In the mITT population, 78% of patients in Arm 1 completed definitive surgery compared to 77% of patients in Arm 2.

The trial demonstrated statistically significant improvements in EFS and pCR rate (see Table 26 and Figure 1) in the IMFINZI in combination with chemotherapy arm compared to the placebo in combination with chemotherapy arm.

Table 26. Efficacy Results for the AEGEAN Study (mITT)
 | IMFINZI 1,500 mg every 3 weeks with chemotherapy/ IMFINZI (N = 366) | Placebo with Chemotherapy/ Placebo (N = 374)
EFS [Results are based on planned EFS interim analysis and pCR final analysis (DCO: 10 November 2022) which occurred 46.3 months after study initiation.]
Number of events, n (%) | 98 (27) | 138 (37)
Median EFS (95% CI) (months) | NR (31.9, NR) | 25.9 (18.9, NR)
Hazard ratio (95% CI) | 0.68 (0.53, 0.88)
2-sided p-value [Compared to a two-sided p-value boundary of 0.00989.] [The 2-sided p-value for pCR was calculated based on a stratified CMH test. The 2-sided p-value for EFS was calculated based on based on a stratified log-rank test. Stratification factors include PD-L1 and disease stage.] | 0.0039
pCR, [Based on a pre-specified pCR interim analysis (DCO: 14 January 2022) in n = 402, the pCR rate was statistically significant (p = 0.000036) compared to significance level of 0.0082%.] ,
Number of patients with response | 63 | 16
pCR rate, % (95% CI) | 17.2 (13.5, 21.5) | 4.3 (2.5, 6.8)
p-value | < 0.0001
Difference in proportions, % (95% CI) [Confidence interval for the difference in proportions was calculated based on stratified Miettinen and Nurminen method.] | 13.0 (8.7, 17.6)

Figure 1. Kaplan-Meier Curves of EFS in the AEGEAN Study

At the interim analysis, the trial demonstrated a statistically significant difference in MPR rate (34% vs. 14%; p < 0.0001). At the time of the prespecified interim analyses, overall survival (OS) was not formally tested for statistical significance.

Unresectable Stage III NSCLC - PACIFIC

The efficacy of IMFINZI was evaluated in the PACIFIC study (NCT02125461), a multicenter, randomized, double-blind, placebo-controlled study in patients with unresectable Stage III NSCLC who completed at least 2 cycles of concurrent platinum-based chemotherapy and definitive radiation within 42 days prior to initiation of the study drug and had a WHO performance status of 0 or 1. The study excluded patients who had progressed following concurrent chemoradiation, patients with active or prior documented autoimmune disease within 2 years of initiation of the study or patients with medical conditions that required systemic immunosuppression. Randomization was stratified by sex, age (< 65 years vs. ≥ 65 years), and smoking history (smoker vs. non-smoker). Patients were randomized 2:1 to receive IMFINZI 10 mg/kg or placebo intravenously every 2 weeks for up to 12 months or until unacceptable toxicity or confirmed RECIST v1.1-defined progression. Assessment of tumor status was performed every 8 weeks. The major efficacy outcome measures were progression-free survival (PFS) as assessed by a BICR RECIST v1.1, and overall survival (OS). Additional efficacy outcome measures included ORR and DoR assessed by BICR.

A total of 713 patients were randomized: 476 patients to the IMFINZI arm and 237 to the placebo arm. The study population characteristics were: median age of 64 years (range: 23 to 90); 70% male; 69% White and 27% Asian; 16% current smokers, 75% former smokers, and 9% never smokers; 51% WHO performance status of 1; 53% with Stage IIIA and 45% were Stage IIIB; 46% with squamous and 54% with non-squamous histology. All patients received definitive radiotherapy as per protocol, of which 92% received a total radiation dose of 54 Gy to 66 Gy; 99% of patients received concomitant platinum-based chemotherapy (55% cisplatin-based, 42% carboplatin-based chemotherapy, and 2% switched between cisplatin and carboplatin).

At a pre-specified interim analysis for OS based on 299 events (61% of total planned events), the study demonstrated a statistically significant improvement in OS in patients randomized to IMFINZI compared to placebo. The pre-specified interim analysis of PFS based on 371 events (81% of total planned events) demonstrated a statistically significant improvement in PFS in patients randomized to IMFINZI compared to placebo. Table 27 and Figure 2 summarizes the efficacy results for PACIFIC.

Table 27. Efficacy Results for the PACIFIC Study
Endpoint | IMFINZI (N = 476) [Among the ITT population, 7% in the IMFINZI arm and 10% in the placebo arm had non-measurable disease as assessed by BICR according to RECIST v1.1] | Placebo (N = 237)
Overall Survival (OS) [OS results are based on the interim OS analysis conducted at 299 OS events which occurred 46 months after study initiation.]
Number of deaths | 183 (38%) | 116 (49%)
Median in months (95% CI) | NR (34.7, NR) | 28.7 (22.9, NR)
Hazard Ratio (95% CI) [Two-sided p-value based on a log-rank test stratified by sex, age, and smoking history] | 0.68 (0.53, 0.87)
p-value [Compared with allocated α of 0.00274 (Lan‑DeMets spending function approximating O’Brien Fleming boundary) for interim analysis] | 0.0025
Progression-Free Survival (PFS) [As assessed by BICR RECIST v1.1] [PFS results are based on the interim PFS analysis conducted at 371 PFS events which occurred 33 months after study initiation.]
Number (%) of patients with event | 214 (45%) | 157 (66%)
Median in months (95% CI) | 16.8 (13.0, 18.1) | 5.6 (4.6, 7.8)
Hazard Ratio (95% CI) [Pike estimator] | 0.52 (0.42, 0.65)
p-value [Compared with allocated α of 0.011035 (Lan‑DeMets spending function approximating O’Brien Fleming boundary) for interim analysis] | < 0.0001

Figure 2. Kaplan-Meier Curves of OS in the PACIFIC Study

Metastatic NSCLC - POSEIDON

The efficacy of IMFINZI in combination with tremelimumab-actl and platinum-based chemotherapy in previously untreated metastatic NSCLC patients with no sensitizing epidermal growth factor receptor (EGFR) mutation or anaplastic lymphoma kinase (ALK) genomic tumor aberrations was investigated in POSEIDON, a randomized, multicenter, active-controlled, open-label study (NCT03164616). Eligible patients had Eastern Cooperative Oncology Group (ECOG) Performance Status of 0 or 1 and must have had no prior chemotherapy or any other systemic therapy for metastatic NSCLC. Choice of platinum-based chemotherapy was at the investigator’s discretion, taking into consideration the calculated creatinine clearance. Patients with active and/or untreated brain metastases; a history of active primary immunodeficiency; autoimmune disorders including active or prior documented autoimmune or inflammatory disorders; use of systemic immunosuppressants within 14 days before the first dose of the treatment except physiological dose of systemic corticosteroids were ineligible.

Randomization was stratified by tumor cells (TC) PD-L1 expression (TC ≥ 50% vs. TC < 50%), disease stage (Stage IVA vs. Stage IVB), and histology (non-squamous vs. squamous).

Patients were randomized 1:1:1 to receive IMFINZI in combination with tremelimumab-actl and platinum-based chemotherapy according to the regimens listed below, IMFINZI and platinum-based chemotherapy (an unapproved regimen for metastatic NSCLC), or platinum-based chemotherapy. The evaluation of efficacy for metastatic NSCLC relied on comparison between:

- IMFINZI 1,500 mg with tremelimumab-actl 75 mg (or 1 mg/kg for patients < 30 kg) and platinum-based chemotherapy every 3 weeks for 4 cycles, followed by IMFINZI 1,500 mg every 4 weeks as a single agent. A fifth dose of tremelimumab-actl 75 mg (or 1 mg/kg for patients < 30 kg) was given at Week 16 in combination with IMFINZI dose 6.
- Platinum-based chemotherapy every 3 weeks as monotherapy for 4 cycles. Patients could receive an additional 2 cycles (a total of 6 cycles post-randomization), as clinically indicated, at investigator’s discretion.

Patients received IMFINZI in combination with tremelimumab-actl with one of the following platinum-based chemotherapy regimens:

- Non-squamous NSCLC
  ∘ Pemetrexed 500 mg/m^2 with carboplatin AUC 5-6 or cisplatin 75 mg/m^2 every 3 weeks for 4 cycles.
- Squamous NSCLC
  ∘ Gemcitabine 1,000 or 1,250 mg/m^2 on Days 1 and 8 with cisplatin 75 mg/m^2 or carboplatin AUC 5-6 on Day 1 every 3 weeks for 4 cycles.
- Non-squamous and Squamous NSCLC
  ∘ Nab-paclitaxel 100 mg/m^2 on Days 1, 8, and 15 with carboplatin AUC 5-6 on Day 1 every 3 weeks for 4 cycles.

Tremelimumab-actl was given up to a maximum of 5 doses. IMFINZI and histology-based pemetrexed continued every 4 weeks until disease progression or unacceptable toxicity. Administration of IMFINZI monotherapy was permitted beyond disease progression if the patient was clinically stable and deriving clinical benefit as determined by the investigator. Patients with disease progression during IMFINZI monotherapy were given the option to be retreated with 4 additional cycles of tremelimumab-actl in combination with IMFINZI. Tumor assessments were performed at Week 6, Week 12, and then every 8 weeks thereafter.

The major efficacy outcome measures were progression free survival (PFS) and overall survival (OS) of IMFINZI and tremelimumab-actl in combination with platinum-based chemotherapy compared to platinum-based chemotherapy alone. Additional efficacy outcome measures were overall response rate (ORR) and duration of response (DoR). PFS, ORR, and DoR were assessed using Blinded Independent Central Review (BICR) according to RECIST v1.1.

A total of 675 patients were randomized to receive either IMFINZI with tremelimumab-actl and platinum-based-chemotherapy (n = 338) or platinum-based chemotherapy (n = 337). The median age was 63 years (range: 27 to 87), 46% of patients age ≥ 65 years, 77% male, 57% White, 34% Asian, 0.3% Native Hawaiian or Other Pacific Islander, 3% American Indian or Alaska Native, 2% Black or African American, 4% Other Race, 79% former or current smoker, 34% ECOG PS 0, and 66% ECOG PS 1. Thirty-six percent had squamous histology, 63% non-squamous histology, 29% PD-L1 expression TC ≥ 50%, 71% PD-L1 expression TC < 50%.

Efficacy results are summarized in Table 28 and Figure 3.

Table 28. Efficacy Results for the POSEIDON Study
 | IMFINZI with tremelimumab-actl and platinum-based chemotherapy (N = 338) | Platinum-based chemotherapy; (N = 337)
OS [PFS/OS results are based on planned analyses which occurred 25/45 months respectively after study initiation.]
Number of deaths (%) | 251 (74) | 285 (85)
Median OS (months) (95% CI) | 14.0; (11.7, 16.1) | 11.7; (10.5, 13.1)
HR (95% CI) | 0.77 (0.65, 0.92)
p-value [2-sided p-values based on log-rank tests stratified by PD-L1, histology and disease stage and compared to a boundary value of 0.00735 for PFS and 0.00797 for OS.] | 0.00304
PFS
Number of events (%) | 238 (70) | 258 (77)
Median PFS (months) (95% CI) | 6.2; (5.0, 6.5) | 4.8; (4.6, 5.8)
HR (95% CI) | 0.72 (0.60, 0.86)
p-value | 0.00031
ORR % (95% CI) [Confirmed responses with 95% Clopper-Pearson confidence interval.] | 39 (34, 44) | 24 (20, 29)
Median DoR (months); (95% CI) | 9.5; (7.2, NR) | 5.1; (4.4, 6.0)

NR=Not Reached, CI=Confidence Interval

Figure 3. Kaplan-Meier Curves of OS in the POSEIDON Study

14.2 Small Cell Lung Cancer (SCLC)

Limited-stage SCLC - ADRIATIC

The efficacy of IMFINZI was evaluated in the ADRIATIC Study (NCT03703297), a randomized, double-blind, placebo-controlled, multicenter study in 730 patients with histologically or cytologically confirmed LS-SCLC (Stage I to III according to AJCC, 8th edition) whose disease had not progressed following concurrent chemoradiation therapy (cCRT). Patients who had Stage I or II disease had to be medically inoperable as determined by the investigator. Eligible patients completed cCRT consisting of 4 cycles of platinum-based chemotherapy and either 60-66 Gy once daily over 6 weeks or 45 Gy twice daily over 3 weeks radiation therapy within 42 days prior to the first dose of IMFINZI or placebo. Prophylactic cranial irradiation (PCI) could be delivered at the discretion of the investigator after cCRT and had to be completed within 42 days prior to the first dose of IMFINZI or placebo. Patients with active or prior documented autoimmune disease within 5 years of initiation into the study; a history of active primary immunodeficiency; a history of Grade ≥ 2 pneumonitis or active tuberculosis or hepatitis B or C or HIV infection; active interstitial lung disease were ineligible. Patients with mixed SCLC and NSCLC histology were also ineligible. Randomization was stratified by stage (I/II versus III) and receipt of PCI (yes versus no).

Patients were randomized 1:1:1 to receive IMFINZI as a single agent, IMFINZI in combination with another agent, or placebo. All study medications were administered intravenously. The evaluation of efficacy for LS-SCLC relied on comparison between:

- Arm 1: IMFINZI 1,500 mg in combination with placebo every 4 weeks for 4 cycles, followed by IMFINZI 1,500 mg every 4 weeks.
- Arm 2: Placebo in combination with a second placebo every 4 weeks for 4 cycles, followed by a single placebo every 4 weeks.

A total of 530 patients were randomized between Arms 1 and 2, 264 patients to the IMFINZI arm and 266 patients to the placebo arm. Treatment continued until disease progression, until unacceptable toxicity, or for a maximum of 24 months. Tumor assessments were conducted every 8 weeks for the first 72 weeks, then every 12 weeks up to 96 weeks and then every 24 weeks thereafter.

The major efficacy outcome measures were OS and PFS assessed by BICR according to RECIST v1.1.

The baseline demographics and disease characteristics for patients in the IMFINZI and placebo arms were as follows: male (69%); age ≥ 65 years (39%); White (50%), Black or African-American (0.8%), Asian (48%), other race (1.3%); Hispanic or Latino (4.2%); current smoker (22%), past-smoker (68%), never smoker (9%); WHO/ECOG PS 0 (49%), WHO/ECOG PS 1 (51%); and Stage I (3.6%), Stage II (9%), Stage III (87%).

Prior to randomization, all patients received platinum-based chemotherapy (66% cisplatin-etoposide, 34% carboplatin-etoposide) with 88% of patients receiving 4 cycles; 72% of patients received once daily radiation (of which 92% received ≥ 60 - ≤ 66 Gy QD); 28% received twice daily radiation (of which 97% received 45 Gy twice daily) and 54% of patients received PCI.

Efficacy results are presented in Table 29 and Figure 4.

Table 279. Efficacy Results for the ADRIATIC Study
 | IMFINZI (N=264) | Placebo (N=266)
OS
Number of deaths (%) | 115 (44) | 146 (55)
Median OS (months) (95% CI) [Calculated using the Kaplan Meier technique. CI for median derived based on Brookmeyer-Crowley method.] | 55.9 (37.3, NR) | 33.4 (25.5, 39.9)
HR (95% CI) [Based on Cox proportional hazards model stratified by receipt of PCI.] | 0.73 (0.57, 0.93)
p-value [Compared with allocated alpha of 0.0168 for OS and 0.0280 for PFS (Lan‑DeMets spending function approximating O’Brien Fleming boundary) for interim analysis.] | 0.0104
PFS [Assessed by BICR according to RECIST v1.1.]
Number of events (%) | 139 (53) | 169 (64)
Median PFS (months) (95% CI) | 16.6 (10.2, 28.2) | 9.2 (7.4, 12.9)
HR (95% CI) [Based on Cox proportional hazards model stratified by TNM stage and receipt of PCI.] | 0.76 (0.61, 0.95)
p-value | 0.0161

Figure 4. Kaplan-Meier Curves of OS in the ADRIATIC Study

Extensive-stage SCLC – CASPIAN

The efficacy of IMFINZI in combination with etoposide and either carboplatin or cisplatin in previously untreated ES-SCLC was investigated in CASPIAN, a randomized, multicenter, active-controlled, open-label study (NCT03043872). Eligible patients had WHO Performance Status of 0 or 1 and were suitable to receive a platinum-based chemotherapy regimen as first-line treatment for SCLC. Patients with asymptomatic or treated brain metastases were eligible. Choice of platinum agent was at the investigator’s discretion, taking into consideration the calculated creatinine clearance. Patients with history of chest radiation therapy; a history of active primary immunodeficiency; autoimmune disorders including paraneoplastic syndrome; active or prior documented autoimmune or inflammatory disorders; use of systemic immunosuppressants within 14 days before the first dose of the treatment except physiological dose of systemic corticosteroids were ineligible.

Randomization was stratified by the planned platinum-based therapy in cycle 1 (carboplatin or cisplatin).

The evaluation of efficacy for ES-SCLC relied on comparison between:

IMFINZI 1,500 mg, and investigator’s choice of carboplatin (AUC 5 or 6 mg/mL/min) or cisplatin (75-80 mg/m^2) on Day 1 and etoposide (80-100 mg/m^2) intravenously on Days 1, 2, and 3 of each 21-day cycle for 4 cycles, followed by IMFINZI 1,500 mg every 4 weeks until disease progression or unacceptable toxicity, or

Investigator’s choice of carboplatin (AUC 5 or 6 mg/mL/min) or cisplatin (75-80 mg/m^2) on Day 1 and etoposide (80-100 mg/m^2) intravenously on Days 1, 2, and 3 of each 21-day cycle, up to 6 cycles. After completion of chemotherapy, PCI as administered per investigator discretion.

Administration of IMFINZI as a single agent was permitted beyond disease progression if the patient was clinically stable and deriving clinical benefit as determined by the investigator.

The major efficacy outcome measure was overall survival (OS) of IMFINZI plus chemotherapy vs. chemotherapy alone. Additional efficacy outcome measures were investigator-assessed progression-free survival (PFS) and objective response rate (ORR), per RECIST v1.1.

The study population characteristics were: median age of 63 years (range: 28 to 82); 40% age 65 or older; 70% male; 84% White, 15% Asian, and 0.9% Black; 65% WHO/ECOG PS of 1; and 93% were former/current smokers. Ninety percent of patients had Stage IV disease and 10% had brain metastasis at baseline. A total of 25% of the patients received cisplatin and 74% of the patients received carboplatin. In the chemotherapy alone arm, 57% of the patients received 6 cycles of chemotherapy, and 8% of the patients received PCI.

The OS results are summarized in Table 30 and Figure 5.

Table 30. OS Results for the CASPIAN Study
Endpoint | IMFINZI with Etoposide and either Carboplatin or Cisplatin; (N = 268) | Etoposide and either Carboplatin or Cisplatin; (N = 269)
Overall Survival (OS)
Number of deaths (%) [At a pre-specified interim analysis, 336 OS events (79% of total planned events) were observed, and the boundary for declaring efficacy (0.0178) was determined by a Lan-Demets alpha spending function with O’Brien Fleming type boundary.] | 155 (58) | 181 (67)
Median OS (months) (95% CI) | 13.0; (11.5, 14.8) | 10.3; (9.3, 11.2)
Hazard Ratio (95% CI) [The analysis was performed using the stratified log-rank test, adjusting for planned platinum therapy in Cycle 1 (carboplatin or cisplatin) and using the rank tests of association approach.] | 0.73 (0.59, 0.91)
p-value | 0.0047

Figure 5. Kaplan-Meier Curves of OS in the CASPIAN Study

Investigator-assessed PFS (96% of total planned events) showed a HR of 0.78 (95% CI: 0.65, 0.94), with median PFS of 5.1 months (95% CI: 4.7, 6.2) in the IMFINZI plus chemotherapy arm and 5.4 months (95% CI: 4.8, 6.2) in the chemotherapy alone arm. The investigator-assessed confirmed ORR was 68% (95% CI: 62%, 73%) in the IMFINZI plus chemotherapy arm and 58% (95% CI: 52%, 63%) in the chemotherapy alone arm.

In the exploratory subgroup analyses of OS based on the planned platinum chemotherapy received at cycle 1, the HR was 0.70 (95% CI 0.55, 0.89) in patients who received carboplatin, and the HR was 0.88 (95% CI 0.55, 1.41) in patients who received cisplatin.

14.3 Biliary Tract Cancer (BTC)

Locally Advanced or Metastatic BTC - TOPAZ-1

The efficacy of IMFINZI in combination with gemcitabine and cisplatin in patients with locally advanced or metastatic BTC was investigated in TOPAZ-1 (NCT03875235), a randomized, double-blind, placebo-controlled, multicenter study that enrolled 685 patients with histologically confirmed locally advanced unresectable or metastatic BTC who have not previously received systemic therapy. Patients with recurrent disease > 6 months after surgery and/or completion of adjuvant therapy were eligible. Patients had an ECOG Performance status of 0 and 1 and at least one target lesion by RECIST v1.1. Patients with ampullary carcinoma; active or prior documented autoimmune or inflammatory disorders; HIV infection or active infections, including tuberculosis or hepatitis C; current or prior use of immunosuppressive medication within 14 days before the first dose of IMFINZI were ineligible.

Randomization was stratified by disease status (recurrent vs. initially unresectable) and primary tumor location (intrahepatic cholangiocarcinoma [ICCA] vs. extrahepatic cholangiocarcinoma [ECCA] vs. gallbladder cancer [GBC]). Patients were randomized 1:1 to receive:

- IMFINZI 1,500 mg on Day 1+ gemcitabine 1,000 mg/m^2 and cisplatin 25 mg/m^2 on Days 1 and 8 of each 21-day cycle up to 8 cycles, followed by IMFINZI 1,500 mg every 4 weeks, or
- Placebo on Day 1+ gemcitabine 1,000 mg/m^2 and cisplatin 25 mg/m^2 on Days 1 and 8 of each 21-day cycle up to 8 cycles, followed by placebo every 4 weeks.

Treatment with IMFINZI or placebo continued until disease progression, or unacceptable toxicity. Treatment beyond disease progression was permitted if the patient was clinically stable and deriving clinical benefit as determined by the investigator.

The major efficacy outcome measure was overall survival (OS). Additional efficacy outcome measures were investigator-assessed progression-free survival (PFS), objective response rate (ORR) and duration of response (DoR). Tumor assessments were conducted every 6 weeks for the first 24 weeks after the date of randomization, and then every 8 weeks until confirmed objective disease progression.

The study population characteristics were: 50% male, median age of 64 years (range 20-85), 47% age 65 or older; 56% Asian, 37% White, 2% Black or African American, 0.1% American Indian or Alaskan Native, and 4% other; 51% had an ECOG PS of 1; primary tumor location was ICCA 56%, ECCA 18% and GBC 25%; 20% of patients had recurrent disease; 86% of patients had metastatic and 14% had locally advanced disease.

At a pre-specified interim analysis, the study demonstrated a statistically significant improvement in OS and PFS in patients randomized to IMFINZI in combination with chemotherapy compared to placebo in combination with chemotherapy. Table 31 summarizes the efficacy results for TOPAZ-1.

Table 31. Efficacy Results for the TOPAZ-1 Study
Endpoint | IMFINZI with Gemcitabine and Cisplatin (N = 341) | Placebo with Gemcitabine and Cisplatin (N = 344)
Overall Survival (OS)
Number of deaths (%) | 198 (58) | 226 (66)
Median OS (months) (95% CI) [Kaplan-Meier estimated median with 95% CI derived using Brookmeyer-Crowley method] | 12.8 (11.1, 14) | 11.5 (10.1, 12.5)
Hazard Ratio (95% CI) [Based on Cox proportional hazards model stratified by disease status and primary tumor location] | 0.80 (0.66, 0.97)
p-value [2-sided p-value based on a stratified log-rank test compared with alpha boundary of 0.030] | 0.021
Progression-Free Survival (PFS)
Number of patients with event (%) | 276 (81) | 297 (86)
Median in months (95% CI) | 7.2 (6.7, 7.4) | 5.7 (5.6, 6.7)
Hazard Ratio (95% CI) | 0.75 (0.63, 0.89)
p-value [2-sided p-value based on a stratified log-rank test compared with alpha boundary of 0.048] | 0.001

The investigator-assessed ORR was 27% (95% CI: 22% - 32%) in the IMFINZI plus chemotherapy arm and 19% (95% CI: 15%-23%) in the chemotherapy alone arm.

Figure 6. Kaplan-Meier Curves of OS in the TOPAZ-1 Study

14.4 Hepatocellular Carcinoma (HCC)

Unresectable HCC - HIMALAYA

The efficacy of IMFINZI in combination with tremelimumab-actl was evaluated in the HIMALAYA study (NCT03298451), a randomized (1:1:1), open-label, multicenter study in patients with confirmed uHCC who had not received prior systemic treatment for HCC. Patients were randomized to one of two investigational arms (IMFINZI plus tremelimumab-actl or IMFINZI) or sorafenib. Study treatment consisted of IMFINZI 1,500 mg in combination with tremelimumab-actl as a one-time single intravenous infusion of 300 mg on the same day, followed by IMFINZI every 4 weeks; IMFINZI 1,500 mg every 4 weeks; or sorafenib 400 mg given orally twice daily, until disease progression or unacceptable toxicity. The efficacy assessment of IMFINZI is based on patients randomized to the IMFINZI plus tremelimumab-actl arm versus the sorafenib arm. Randomization was stratified by macrovascular invasion (MVI) (yes or no), etiology of liver disease (hepatitis B virus vs. hepatitis C virus vs. others) and ECOG performance status (0 vs. 1).

The study enrolled patients with BCLC Stage C or B (not eligible for locoregional therapy). The study excluded patients with co-infection of viral hepatitis B and hepatitis C; active or prior documented gastrointestinal (GI) bleeding within 12 months; ascites requiring non-pharmacologic intervention within 6 months; hepatic encephalopathy within 12 months before the start of treatment; active or prior documented autoimmune or inflammatory disorders. Esophagogastroduodenoscopy was not mandated prior to enrollment but adequate endoscopic therapy, according to institutional standards, was required for patients with history of esophageal variceal bleeding or those assessed as high risk for esophageal variceal bleeding by the treating physician.

Study treatment was permitted beyond disease progression if the patient was clinically stable and deriving clinical benefit as determined by the investigator.

The major efficacy outcome measure was overall survival (OS) between the IMFINZI plus tremelimumab-actl arm versus the sorafenib arm. Additional efficacy outcomes were investigator-assessed progression-free survival (PFS), objective response rate (ORR) and duration of response (DoR) according to RECIST v1.1. Tumor assessments were conducted every 8 weeks for the first 12 months and then every 12 weeks thereafter.

The baseline demographics of the IMFINZI plus tremelimumab-actl and sorafenib arms were as follows: male (85%), age < 65 years (50%), median age of 65 years (range: 18 to 88 years), White (46%), Asian (49%), Black or African American (2%), Native Hawaiian or other Pacific Islander (0.1%), race Unknown (2%), Hispanic or Latino (5%), Not Hispanic or Latino (94%), ethnicity Unknown (1%), ECOG PS 0 (62%); Child-Pugh Class score A (99%), macrovascular invasion (26%), extrahepatic spread (53%), viral etiology; hepatitis B (31%), hepatitis C (27%), and uninfected (42%).

Efficacy results are presented in Table 32 and Figure 7.

Table 32. Efficacy Results for the HIMALAYA Study
Endpoint | IMFINZI and Tremelimumab-actl (N = 393) | Sorafenib (N = 389)
OS
Number of deaths (%) | 262 (66.7) | 293 (75.3)
Median OS (months); (95% CI) | 16.4; (14.2, 19.6) | 13.8; (12.3, 16.1)
HR (95% CI) [HR (IMFINZI and tremelimumab-actl vs. sorafenib) based on the stratified Cox proportional hazard model.] | 0.78 (0.66, 0.92)
p-value [Based on a stratified log-rank test.] [Based on a Lan-DeMets alpha spending function with O'Brien Fleming type boundary and the actual number of events observed, the boundary for declaring statistical significance for IMFINZI and tremelimumab-actl vs. sorafenib was 0.0398 (Lan and DeMets 1983).] | 0.0035
PFS
Number of events (%) | 335 (85.2) | 327 (84.1)
Median in (months); (95% CI) | 3.8; (3.7, 5.3) | 4.1; (3.7, 5.5)
HR (95% CI) | 0.90 (0.77, 1.05)
ORR
ORR % (95% CI) [Confirmed complete response or partial response.] [Based on Clopper-Pearson method.] | 20.1 (16.3, 24.4) | 5.1 (3.2, 7.8)
Complete Response n (%) | 12 (3.1) | 0
Partial Response n (%) | 67 (17.0) | 20 (5.1)
DoR
Median DoR (months) (95% CI) | 22.3 (13.7, NR) | 18.4 (6.5, 26.0)
% with duration ≥ 6 months | 82.3 | 78.9
% with duration ≥ 12 months | 65.8 | 63.2

CI=Confidence Interval, HR=Hazard Ratio, NR=Not Reached

Figure 7. Kaplan-Meier Curves of OS in the Himalaya Study

14.5 Endometrial cancer

Advanced or Recurrent dMMR Endometrial Cancer - DUO-E

IMFINZI was evaluated in combination with carboplatin and paclitaxel in DUO-E (NCT04269200), a randomized, multicenter, double-blind, placebo-controlled study in patients with advanced or recurrent endometrial cancer. The trial enrolled patients with newly diagnosed Stage III disease (with measurable disease per RECIST v1.1), or newly diagnosed Stage IV disease. The trial also enrolled patients with recurrent disease with a low potential for cure by radiation therapy or surgery. For patients with recurrent disease, prior chemotherapy was allowed only if it was administered in the adjuvant setting and at least 12 months had elapsed from the date of last dose of chemotherapy to the date of relapse. The trial included patients with epithelial endometrial carcinomas of all histologies, including carcinosarcomas. Patients with endometrial sarcoma were excluded, and patients who had active autoimmune disease or a medical condition that required immunosuppression were ineligible.

Randomization was stratified by tumor mismatch repair (MMR) status (proficient or deficient), disease status (recurrent or newly diagnosed), and geographic region (Asia or rest of the world). MMR status was assessed using an FDA-approved test.

Patients were randomized (1:1:1) to one of the following treatment arms:

- IMFINZI 1,120 mg in combination with carboplatin and paclitaxel every 3 weeks for a maximum of 6 cycles. Following completion of chemotherapy treatment, patients received IMFINZI 1,500 mg every 4 weeks as maintenance treatment until disease progression.
- Placebo in combination with carboplatin and paclitaxel every 3 weeks for a maximum of 6 cycles. Following completion of chemotherapy treatment, patients received placebo every 4 weeks as maintenance treatment until disease progression.
- An additional investigational combination regimen.

Treatment was continued until Response Evaluation Criteria in Solid Tumors (RECIST) v1.1-defined progression of disease or unacceptable toxicity. Assessment of tumor status was performed every 9 weeks for the first 18 weeks and every 12 weeks thereafter.

The major efficacy outcome measure was progression-free survival (PFS), determined by investigator assessment using RECIST 1.1. Additional efficacy outcome measures included overall response rate (ORR), duration of response (DOR) and overall survival (OS).

Among 95 patients with dMMR tumor, the baseline characteristics were median age of 63 years (range: 34 to 85); 47% age 65 or older; 62% White, 31% Asian, 2% Black or African American; 7% Hispanic or Latino, 1% American Indian or Alaska Native, and 4% other or not reported; ECOG PS of 0 (55%) or 1 (45%); 48% newly diagnosed (11% Stage III and 38% Stage IV) and 52% recurrent disease. The histologic subtypes were endometrioid (78%), mixed epithelial (6%), carcinosarcoma (5%), serous (4%), undifferentiated (1%), and other (5%).

While a statistically significant improvement in PFS was observed in the overall population for IMFINZI with carboplatin and paclitaxel compared to carboplatin and paclitaxel alone, based on an exploratory analysis by MMR status, the PFS improvement in the overall population was primarily attributed to patients with dMMR tumors.

Efficacy results for DUO-E are summarized in Table 33 and Figure 8 for patients with dMMR tumors. OS data in this subpopulation at the time of PFS analysis were immature with 26% of patients who died.

Table 33. Efficacy Results for Patients with dMMR Tumors in the DUO-E Study
Endpoint | IMFINZI with Carboplatin and Paclitaxel; N=46 | Carboplatin and Paclitaxel; N=49
PFS [Investigator assessed.]
Number of events (%) | 15 (32.6) | 25 (51.0)
Median in months (95% CI) [Calculated using the Kaplan-Meier technique.] | NR; (NR, NR) | 7.0; (6.7, 14.8)
HR (95% CI) | 0.42 (0.22, 0.80)
ORR | N=42 | N=42
ORR % (95% CI) | 71.4; (55.4, 84.3) | 40.5; (25.6, 56.7)
Complete response % | 12 (28.6) | 4 (9.5)
Partial response | 18 (42.9) | 13 (31.0)
DOR
Median in months (range) | NR; (2.4+, 26.9+) | 10.5; (2.1+, 25.2+)

CI=Confidence Interval, HR=Hazard Ratio, NR=Not Reached, + = response ongoing at last assessment.

Figure 8. Kaplan-Meier curves of PFS for Patients with dMMR Tumors in the DUO-E Study

14.6 Muscle invasive bladder cancer (MIBC)

MIBC – NIAGARA Study

The efficacy of neoadjuvant IMFINZI in combination with gemcitabine and cisplatin followed by adjuvant IMFINZI as a single agent in patients with MIBC was evaluated in NIAGARA (NCT03732677), a randomized, open-label, multicenter study. The study randomized (1:1) 1,063 patients who were candidates for radical cystectomy and who had not received prior systemic chemotherapy or immune-mediated therapy for the treatment of NMIBC or MIBC. The study excluded patients with pure non-urothelial histology, any small cell histology and primary non-bladder (i.e., ureter, urethral, or renal pelvis) cancer of the urothelium.

Randomization was stratified by clinical tumor stage T2N0 vs. > T2N0 (including T2N1, T3, and T4a), renal function (creatinine clearance [CrCl] ≥ 60 mL/min vs. CrCl ≥ 40 mL/min to < 60 mL/min), and PD-L1 expression (high vs. low/negative). Patients received:

- Neoadjuvant IMFINZI 1,500 mg plus gemcitabine 1,000 mg/m^2 and cisplatin 70 mg/m^2 every 3 weeks for 4 cycles prior to surgery, followed by IMFINZI 1,500 mg every 4 weeks as a single agent adjuvant treatment for up to 8 cycles after surgery, or
- Neoadjuvant gemcitabine 1,000 mg/m^2 and cisplatin 70 mg/m^2 every 3 weeks for 4 cycles prior to surgery, without adjuvant treatment.

Patients with CrCl ≥ 40 mL/min to < 60 mL/min in both arms received split-dose cisplatin of 35 mg/m^2 on days 1 and 8 of each cycle.

A RECIST 1.1 tumor assessment was performed at baseline and upon completion of neoadjuvant therapy (prior to surgery). After surgery, tumor assessments were performed every 12 weeks for the first 24 months, then every 24 weeks for 36 months, and then every 52 weeks thereafter until progression, the end of study, or death.

The major efficacy outcome measure was EFS by BICR assessment. OS was an additional efficacy outcome measure.

Baseline demographics were: male (82%), median age 65 years (range: 32 to 84), age ≥65 years (53%), White (67%), Asian (28%), Black or African American (0.9%), other (0.8%), Hispanic or Latino (8%), and ECOG PS 0 (78%) vs. PS 1 (22%). Disease characteristics were: tumor stage T2N0 (40%) and >T2N0 (60%), regional lymph nodes N0 (95%) and N1 (5%), adequate renal function (81%) and borderline renal function (19%). The histologic subtypes included urothelial carcinoma (85%) and urothelial carcinoma with variant histology (15%).

In the overall population, 469 (88%) patients in the IMFINZI plus gemcitabine and cisplatin arm and 441 (83%) patients in the gemcitabine and cisplatin arm underwent radical cystectomy.

At a pre-specified interim analysis, the study demonstrated a statistically significant improvement in EFS and OS in the IMFINZI plus gemcitabine and cisplatin arm compared to the gemcitabine and cisplatin arm. The trial was not designed to isolate the effect of IMFINZI in each phase (neoadjuvant or adjuvant) of treatment. See Table 34 and Figures 9 and 10.

Table 34. Efficacy Results for the NIAGARA Study
 | IMFINZI plus gemcitabine and cisplatin; (N=533) | Gemcitabine and cisplatin; (N = 530)
EFS [EFS is defined as the time from randomization to the first recurrence of disease after radical cystectomy, the time of first documented progression in patients who are medically precluded from a radical cystectomy, or time of expected surgery in patients who refuse to undergo a radical cystectomy or failure to undergo a radical cystectomy in participants with residual disease, or the time of death due to any cause, whichever occurs first.]
Number of events (%) | 187. (35.1) | 246 (46.4)
Median EFS (months) (95% CI) | NR (NR, NR) | 46.1 (32.2, NR)
HR (95% CI) [Based on stratified Cox proportional hazard model.] | 0.68 (0.56, 0.82)
2-sided p-value [Based on stratified log-rank test.] , [Alpha allocated at the interim analysis was 0.0412 for EFS and 0.0154 for OS.] | <0.0001
Overall Survival (OS)
Number of events (%) | 136.(25.5) | 169 (31.9
Median OS (months) (95% CI) | NR (NR, NR) | NR (NR, NR)
HR (95% CI) | 0.75 (0.59, 0.93)
2-sided p-value, | 0.0106

CI = Confidence Interval, HR = Hazard Ratio, NR = Not Reached

Figure 9. Kaplan-Meier Curve of EFS

Figure 10. Kaplan-Meier Curve of OS

14.7 Gastric or gastroesophageal junction adenocarcinoma (GC/GEJC)

Neoadjuvant and Adjuvant Treatment of Resectable GC/GEJC – MATTERHORN Study

The efficacy of IMFINZI with FLOT as neoadjuvant and adjuvant treatment, followed by IMFINZI as a single agent, was investigated in MATTERHORN (NCT04592913), a randomized, double-blind, placebo-controlled, multicenter study conducted in 948 patients with previously untreated and resectable GC/GEJC (Stage II to Stage IVA [AJCC, 8th edition]). Eligible patients had no prior exposure to immune-mediated therapy and a WHO/ECOG performance status of 0 or 1. Patients with active or prior documented autoimmune or inflammatory disorders, or use of immunosuppressive medication within 14 days of the first dose of durvalumab were ineligible.

Randomization was stratified by geographic region (Asia vs. non-Asia), clinical lymph node status (positive vs. negative), and PD-L1 expression status (TAP < 1% vs. TAP ≥ 1%).

Patients were randomized in a 1:1 ratio to one of the following treatment arms. Crossover between the study arms was not permitted.

- IMFINZI 1,500 mg on Day 1 + FLOT on Days 1 and 15 of every 4-week cycle for 2 cycles in the neoadjuvant phase and 2 cycles in the adjuvant phase followed by IMFINZI 1,500 mg on Day 1 every 4 weeks for up to 10 additional cycles for a total of 12 cycles (1 dose per cycle)
- Placebo on Day 1 + FLOT on Days 1 and 15 of every 4-week cycle for 2 cycles in the neoadjuvant phase and 2 cycles in the adjuvant phase followed by placebo on Day 1 every 4 weeks for up to 10 additional cycles for a total of 12 cycles (1 dose per cycle)

Tumor assessment per RECIST was performed prior to the start of neoadjuvant therapy, prior to surgery, before starting adjuvant treatment and then every 12 weeks for 2 years and every 24 weeks until RECIST 1.1 defined radiological progression, consent withdrawal, or death.

The major efficacy outcome measure of the study was EFS by BICR assessment. EFS was defined as the earliest of one of the following: disease progression according to RECIST 1.1 that precluded surgery or that required non-protocol therapy during the neoadjuvant treatment period; progression (after R1/R2 resection) or recurrence (after R0 resection), according to RECIST 1.1, during the adjuvant treatment period; non-RECIST progression (according to investigator assessment or confirmed by local pathology testing) that precluded surgery or that required non-protocol therapy during the neoadjuvant treatment period, or that was discovered during surgery; progression or recurrence confirmed by local pathology testing after surgery; or death.

Additional efficacy outcome measures were OS and pCR rate by blinded central pathology review. The trial was not designed to isolate the effect of IMFINZI in each phase (neoadjuvant or adjuvant) of treatment.

The demographics were as follows: median age 62 years (range: 26 to 84), age ≥65 years (41%), male (72%), White (68%), Asian (20%), American Indian or Alaska Native (4%), Black or African American (1.1%), other race (1.7%), Hispanic or Latino (20%), and WHO/ECOG PS 0 (74%). Disease characteristics were as follows: Stage II (29%), Stage III (62%), Stage IVA (9%), gastric (68%), gastroesophageal junction (32%), Siewert type 1 (10%), Siewert type 2 (15%), Siewert type 3 (7%), intestinal type (51%), diffuse type (26%), indeterminate type (23%), clinical lymph node status positive (70%), clinical lymph node status negative (29%), PD-L1 expression status TAP ≥1% (90%), and PD-L1 expression status TAP <1% (10%).

There were 412 (87%) patients in the IMFINZI arm who completed curative intent surgery compared to 400 (84%) patients in the placebo arm. Surgery was delayed (defined as surgery attempt >8 weeks from last dose of neoadjuvant therapy) in 48 (10%) patients in the IMFINZI arm and 51 (11%) patients in the placebo arm. In the IMFINZI arm, 248 (52%) and 291 (61%) patients completed the two cycles of adjuvant IMFINZI and two cycles of adjuvant FLOT, respectively. In the placebo arm, 245 (52%) and 303 (64%) patients completed the two cycles of adjuvant placebo and two cycles of adjuvant FLOT, respectively. There were 344 (73%) patients in the IMFINZI arm who initiated adjuvant IMFINZI monotherapy compared to 332 (70%) patients in the placebo arm.

The study demonstrated a statistically significant improvement in EFS in the IMFINZI arm compared to the placebo arm. See Table 35, Figure 11, and Figure 12.

Table 35. Efficacy Results for the MATTERHORN Study
 | IMFINZI + FLOT chemotherapy (N = 474) | Placebo + FLOT chemotherapy (N = 474)
Event Free Survival (EFS)
Number of events, n (%) | 167 (35) | 218 (46)
Median EFS (months) (95% CI) | NR (40.7, NE) | 32.8 (27.9, NE)
HR (95% CI) | 0.71 (0.58, 0.86)
p-value | <0.001
Overall Survival (OS)
Number of events (%) | 160 (33.8) | 192 (40.5)
Median OS (months) (95% CI) | NR (NE, NE) | NR (NE, NE)
HR (95% CI) | 0.78 (0.63, 0.96)
p-value | 0.021
pCR [Results for EFS are based on a pre-specified interim analysis (DCO: 20 December 2024), results for OS are based on a pre-specified final analysis (DCO: 01 September 2025), and results for pCR are based on a pre-specified final analysis (DCO: 01 February 2023).]
Number of patients with response | 91 | 34
Response rate, (%) (95% CI) | 19.2 (15.7, 23.0) | 7.2 (5.0, 9.9)
p-value | <0.001

CI=Confidence Interval, HR=Hazard Ratio, NE=Not estimable, NR=Not reached

Figure 11. Kaplan-Meier Curve of EFS

Figure 12. Kaplan-Meier Curve of OS

16 HOW SUPPLIED/STORAGE AND HANDLING

IMFINZI (durvalumab) Injection is a clear to opalescent, colorless to slightly yellow solution supplied in a carton containing one single-dose vial either as:

- 500 mg/10 mL (50 mg/mL) (NDC 0310-4611-50)
- 120 mg/2.4 mL (50 mg/mL) (NDC 0310-4500-12)

Store in a refrigerator at 2°C to 8°C (36°F to 46°F) in original carton to protect from light.

Do not freeze. Do not shake.

17 PATIENT COUNSELING INFORMATION

Advise the patient to read the FDA-approved patient labeling (Medication Guide).

Immune-Mediated Adverse Reactions

Inform patients of the risk of immune-mediated adverse reactions that may require corticosteroid treatment and interruption or discontinuation of IMFINZI [see Warnings and Precautions (5.1)], including:

- Pneumonitis: Advise patients to contact their healthcare provider immediately for any new or worsening cough, chest pain, or shortness of breath.
- Hepatitis: Advise patients to contact their healthcare provider immediately for jaundice, severe nausea or vomiting, pain on the right side of abdomen, lethargy, or easy bruising or bleeding.
- Colitis: Advise patients to contact their healthcare provider immediately for diarrhea, blood or mucus in stools, or severe abdominal pain.
- Endocrinopathies: Advise patients to contact their healthcare provider immediately for signs or symptoms of hypothyroidism, hyperthyroidism, adrenal insufficiency, type 1 diabetes mellitus, or hypophysitis.
- Nephritis: Advise patients to contact their healthcare provider immediately for signs or symptoms of nephritis.
- Dermatological Reactions: Advise patients to contact their healthcare provider immediately for signs or symptoms of severe dermatological reactions.
- Pancreatitis: Advise patients to contact their healthcare provider immediately for signs or symptoms of pancreatitis.
- Other Immune-Mediated Adverse Reactions: Advise patients to contact their healthcare provider immediately for signs or symptoms of pancreatitis, aseptic meningitis, encephalitis, immune thrombocytopenia, myocarditis, hemolytic anemia, myositis, uveitis, keratitis, and myasthenia gravis.

Infusion-Related Reactions:

- Advise patients to contact their healthcare provider immediately for signs or symptoms of infusion-related reactions [see Warnings and Precautions (5.2)].

Complications of Allogeneic HSCT:

- Advise patients of potential risk of post-transplant complications [see Warnings and Precautions (5.3)].

Embryo-Fetal Toxicity:

- Advise females of reproductive potential that IMFINZI can cause harm to a fetus and to inform their healthcare provider of a known or suspected pregnancy [see Warnings and Precautions (5.4) and Use in Specific Populations (8.1,8.3)].
- Advise females of reproductive potential to use effective contraception during treatment and for 3 months after the last dose of IMFINZI [see Use in Specific Populations (8.3)].

Lactation:

- Advise female patients not to breastfeed while taking IMFINZI and for 3 months after the last dose [see Warnings and Precautions (5.4) and Use in Specific Populations (8.2)].

Manufactured for:

AstraZeneca Pharmaceuticals LP
Wilmington, DE 19850

MEDICATION GUIDE

IMFINZI® (im-FIN-zee)

(durvalumab)

injection

What is the most important information I should know about IMFINZI?

IMFINZI is a medicine that may treat certain cancers by working with your immune system.

IMFINZI can cause your immune system to attack normal organs and tissues in any area of your body and can affect the way they work. These problems can sometimes become severe or life-threatening and can lead to death. You can have more than one of these problems at the same time. These problems may happen anytime during treatment or even after your treatment has ended.

Call or see your healthcare provider right away if you develop any new or worsening signs or symptoms, including:

- Lung problems.

∘ cough

∘ shortness of breath

∘ chest pain

- Intestinal problems.

∘ diarrhea (loose stools) or more frequent bowel movements than usual
∘ stools that are black, tarry, sticky, or have blood or mucus

∘ severe stomach-area (abdomen) pain or tenderness

- Liver problems.

∘ yellowing of your skin or the whites of your eyes
∘ severe nausea or vomiting
∘ pain on the right side of your stomach-area (abdomen)

∘ dark urine (tea colored)
∘ bleeding or bruising more easily than normal

- Hormone and gland problems.

∘ headaches that will not go away or unusual headaches
∘ eye sensitivity to light
∘ eye problems
∘ rapid heartbeat
∘ increase sweating
∘ extreme tiredness
∘ weight gain or weight loss
∘ feeling more hungry or thirsty than usual

∘ urinating more often than usual
∘ hair loss
∘ feeling cold
∘ constipation
∘ your voice gets deeper
∘ dizziness or fainting
∘ changes in mood or behavior, such as decreased sex drive, irritability, or forgetfulness

- Kidney problems.

∘ decrease in your amount of urine
∘ blood in your urine

∘ swelling of your ankles
∘ loss of appetite

- Skin problems.

∘ rash
∘ itching
∘ skin blistering or peeling

∘ painful sores or ulcers in mouth or nose, throat, or genital area
∘ fever or flu-like symptoms
∘ swollen lymph nodes

- Pancreas problems.

∘ pain in your upper stomach area (abdomen)
∘ severe nausea or vomiting

∘ loss of appetite

- Problems can also happen in other organs and tissues. These are not all of the signs and symptoms of immune system problems that can happen with IMFINZI. Call or see your healthcare provider right away for any new or worsening signs or symptoms, which may include:

∘ chest pain, irregular heartbeats, shortness of breath or swelling of ankles
∘ confusion, sleepiness, memory problems, changes in mood or behavior, stiff neck, balance problems
∘ tingling, numbness or weakness of the arms or legs
∘ double vision, blurry vision, sensitivity to light, eye pain, changes in eye-sight
∘ persistent or severe muscle pain or weakness, muscle cramps, joint pain, joint stiffness or swelling
∘ low red blood cells, bruising

- Infusion reactions that can sometimes be severe or life-threatening. Signs and symptoms of infusion reactions may include:

∘ chills or shaking
∘ itching or rash
∘ flushing
∘ shortness of breath or wheezing

∘ dizziness
∘ feel like passing out
∘ fever
∘ back or neck pain

- Rejection of a transplanted organ or tissue. Your healthcare provider should tell you what signs and symptoms you should report and monitor you depending on the type of organ or tissue transplant that you have had.
- Complications, including graft-versus-host disease (GVHD), in people who have received a bone marrow (stem cell) transplant that uses donor stem cells (allogeneic). These complications can be serious and can lead to death. These complications may happen if you underwent transplantation either before or after being treated with IMFINZI. Your healthcare provider will monitor you for these complications.

Getting medical treatment right away may help keep these problems from becoming more serious.

Your healthcare provider will check you for these problems during your treatment with IMFINZI. Your healthcare provider may treat you with corticosteroid or hormone replacement medicines. Your healthcare provider may also need to delay or completely stop treatment with IMFINZI, if you have severe side effects.

What is IMFINZI?

IMFINZI is a prescription medicine used to treat adults with:

- a type of lung cancer called non-small cell lung cancer (NSCLC).
  ∘ IMFINZI may be used in combination with chemotherapy that contains platinum prior to surgery and alone after surgery when your NSCLC:
    - can be removed by surgery, and
    - is not known to have an abnormal “EGFR” or “ALK” gene.
  ∘ IMFINZI may be used alone when your NSCLC:
    - has not spread outside your chest
    - cannot be removed by surgery, and
    - has responded or stabilized with initial treatment with chemotherapy that contains platinum, given at the same time as radiation therapy.
  ∘ IMFINZI may be used in combination with tremelimumab-actl and chemotherapy that contains platinum when your NSCLC:
    - has spread to other parts of your body (metastatic), and
    - does not have an abnormal “EGFR” or “ALK” gene.
- a type of lung cancer called small cell lung cancer (SCLC).
  ∘ for limited-stage small cell lung cancer (LS-SCLC), IMFINZI may be used alone when your LS-SCLC cannot be removed by surgery, and
  ∘ has responded or stabilized after initial treatment with chemotherapy that contains platinum, given at the same time as radiation therapy.
  ∘ for extensive-stage small cell lung cancer (ES-SCLC), IMFINZI may be used with the chemotherapy medicines etoposide and either carboplatin or cisplatin as your first treatment when your ES-SCLC has spread within your lungs or to other parts of the body.
- a type of cancer called biliary tract cancer (BTC), including cancer of the bile ducts (cholangiocarcinoma) and gallbladder cancer. IMFINZI may be used in combination with chemotherapy medicines gemcitabine and cisplatin when your BTC:
  ∘ has spread to nearby tissues (locally advanced), or
  ∘ has spread to other parts of the body (metastatic).
- a type of liver cancer that cannot be removed by surgery (unresectable hepatocellular carcinoma or uHCC). IMFINZI is used in combination with tremelimumab-actl to treat uHCC.
- a type of uterine cancer called endometrial cancer. IMFINZI may be used in combination with chemotherapy medicines carboplatin and paclitaxel followed by IMFINZI alone when your endometrial cancer:
  ∘ has spread (advanced) or has come back (recurrent), and
  ∘ a laboratory test shows that your tumor is mismatch repair deficient (dMMR).
- a type of bladder cancer called muscle invasive bladder cancer (MIBC) that has spread into the muscle layer of the bladder but not to other parts of the body. IMFINZI may be used in combination with gemcitabine and cisplatin (neoadjuvant treatment) prior to the surgical removal of your bladder followed by IMFINZI alone after surgery (adjuvant treatment).
- A type of stomach cancer called gastric cancer (GC) or gastro-esophageal junction adenocarcinoma (GEJC) that can be removed by surgery. IMFINZI is used in combination with fluorouracil, leucovorin, oxaliplatin and docetaxel (FLOT) prior to and after surgery followed by IMFINZI alone.

It is not known if IMFINZI is safe and effective in children.

Before you receive IMFINZI, tell your healthcare provider about all of your medical conditions, including if you:

- have immune system problems such as Crohn's disease, ulcerative colitis, or lupus
- have received an organ or tissue transplant, including corneal transplant
- have received or plan to receive a stem cell transplant that uses donor stem cells (allogeneic)
- have received radiation treatment to your chest area
- have a condition that affects your nervous system, such as myasthenia gravis or Guillain-Barré syndrome
- are pregnant or plan to become pregnant. IMFINZI can harm your unborn baby

Females who are able to become pregnant:

  ∘ Your healthcare provider will give you a pregnancy test before you start treatment with IMFINZI.
  ∘ You should use an effective method of birth control during your treatment and for 3 months after the last dose of IMFINZI. Talk to your healthcare provider about birth control methods that you can use during this time.
  ∘ Tell your healthcare provider right away if you become pregnant or think you may be pregnant during treatment with IMFINZI.
- are breastfeeding or plan to breastfeed. It is not known if IMFINZI passes into your breast milk. Do not breastfeed during treatment and for 3 months after the last dose of IMFINZI.

Tell your healthcare provider about all the medicines you take, including prescription and over-the-counter medicines, vitamins, and herbal supplements.

How will I receive IMFINZI?

- Your healthcare provider will give you IMFINZI into your vein through an intravenous (IV) line over 60 minutes.
- IMFINZI is usually given every 2, 3 or 4 weeks.
- Your healthcare provider will decide how many treatments you need.
- Your healthcare provider will test your blood to check you for certain side effects.
- If you miss any appointments, call your healthcare provider as soon as possible to reschedule your appointment.

What are the possible side effects of IMFINZI?

IMFINZI can cause serious side effects, including:

See “What is the most important information I should know about IMFINZI?”

The most common side effects of IMFINZI when used with platinum-containing chemotherapy in adults with NSCLC that can be removed by surgery include:

- low red blood cells (anemia)
- nausea
- constipation

- feeling tired
- muscle or bone pain
- rash

The most common side effects of IMFINZI when used alone in adults with NSCLC that cannot be removed by surgery include:

- cough
- feeling tired
- inflammation in the lungs

- upper respiratory tract infections
- shortness of breath
- rash

The most common side effects of IMFINZI when used with tremelimumab-actl and platinum-containing chemotherapy in adults with metastatic NSCLC include:

- nausea
- feeling tired or weak
- muscle or bone pain

- decreased appetite
- rash
- diarrhea

The most common side effects of IMFINZI when used alone in adults with LS-SCLC include:

- inflammation in the lungs

- feeling tired or weak

The most common side effects of IMFINZI when used with etoposide and either carboplatin or cisplatin in adults with ES-SCLC include:

- nausea
- hair loss

- feeling tired or weak

The most common side effects of IMFINZI when used with gemcitabine and cisplatin in adults with BTC include:

- feeling tired
- nausea
- constipation
- decreased appetite

- stomach (abdominal) pain
- rash
- fever

The most common side effects of IMFINZI when used with tremelimumab-actl in adults with uHCC include:

- rash
- diarrhea
- feeling tired

- itchiness
- muscle or bone pain
- stomach (abdominal) pain

The most common side effects of IMFINZI when used with carboplatin and paclitaxel in adults with endometrial cancer include:

- inflammation of the nerves causing numbness, weakness, tingling or burning pain of the arms and legs
- muscle or bone pain
- nausea
- hair loss
- feeling tired
- stomach (abdominal) pain
- constipation
- rash

- decreased level of magnesium in the blood
- increased liver function tests
- diarrhea
- vomiting
- cough
- decreased level of potassium in the blood
- shortness of breath
- headache
- increased level of alkaline phosphatase in the blood

The most common side effects of IMFINZI when used with gemcitabine and cisplatin in adults with MIBC include:

- decreased red blood cells (anemia)
- decreased white blood cells
- increased level of creatinine in the blood
- decreased level of sodium in the blood
- nausea
- increased liver function tests
- decreased level of calcium in the blood
- decreased blood platelet counts
- feeling tired
- increased level of potassium in the blood

- decreased lymphocyte counts
- constipation
- decreased level of magnesium in the blood
- decreased appetite
- increased level of alkaline phosphatase in the blood
- rash
- fever
- diarrhea
- vomiting
- stomach (abdominal) pain

The most common side effects of IMFINZI when used with FLOT in adults with GC or GEJC include:

Tell your healthcare provider if you have any side effect that bothers you or that does not go away.

These are not all of the possible side effects of IMFINZI. Ask your healthcare provider or pharmacist for more information.

Call your doctor for medical advice about side effects. You may report side effects to FDA at 1-800-FDA-1088.

General information about the safe and effective use of IMFINZI.

Medicines are sometimes prescribed for purposes other than those listed in a Medication Guide. If you would like more information about IMFINZI, talk with your healthcare provider. You can ask your healthcare provider for information about IMFINZI that is written for health professionals.

What are the ingredients in IMFINZI?

Active ingredient: durvalumab

Inactive ingredients: L-histidine, L-histidine hydrochloride monohydrate, α,α-trehalose dihydrate, polysorbate 80, Water for Injection, USP.

Manufactured for: AstraZeneca Pharmaceuticals LP, Wilmington, DE 19850

By: AstraZeneca UK Limited, 1 Francis Crick Ave. Cambridge, England CB2 0AA
US License No. 2043

IMFINZI is a registered trademark of AstraZeneca group of companies.

For more information, call 1-800-236-9933 or go to www.IMFINZI.com

© AstraZeneca 2025

This Medication Guide has been approved by the U.S. Food and Drug Administration. Revised: 11/2025

PACKAGE/LABEL PRINCIPAL DISPLAY PANEL

NDC 0310-4500-12

Rx only

IMFINZI™
(durvalumab)
Injection

120 mg/2.4 mL
(50 mg/mL)

For Intravenous Infusion After Dilution
Single-dose vial. Discard unused portion.
Store at 2° to 8°C (36° to 46°F).
Do not freeze or shake.
Keep vial in original carton to protect from light.
Attention Pharmacist: Dispense the accompanying Medication Guide to each patient.
Do not use if vial seal is broken or missing.

Must dilute before use.
See prescribing information.

AstraZeneca

PACKAGE/LABEL DISPLAY PANEL

NDC 0310-4611-50

Rx only

IMFINZI™
(durvalumab)
Injection

500 mg/10 mL
(50 mg/mL)

For Intravenous Infusion After Dilution
Single-dose vial. Discard unused portion.
Store at 2° to 8°C (36° to 46°F).
Do not freeze or shake.
Keep vial in original carton to protect from light.
Attention Pharmacist: Dispense the accompanying Medication Guide to each patient.
Do not use if vial seal is broken or missing.

Must dilute before use.
See prescribing information.

AstraZeneca